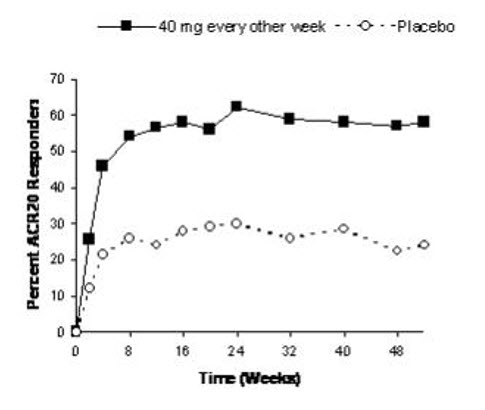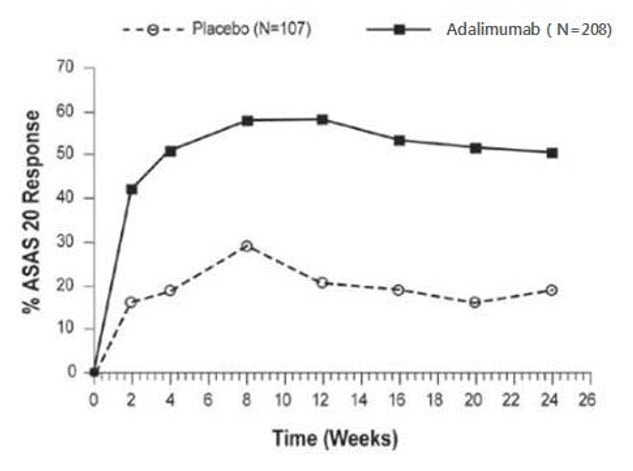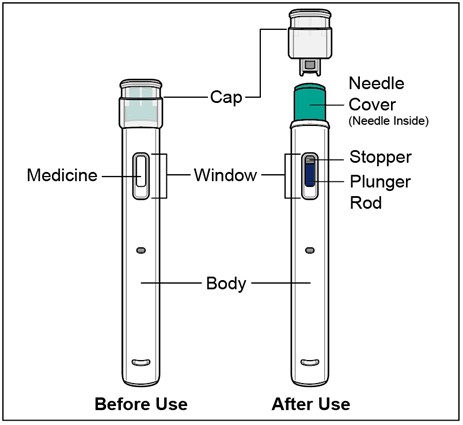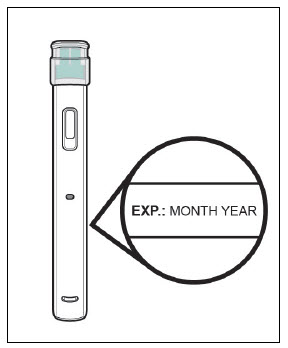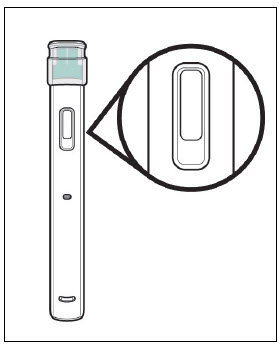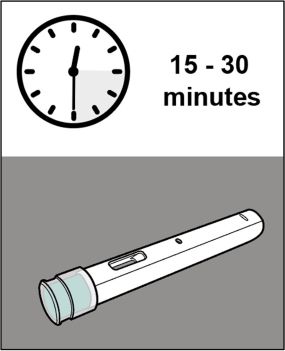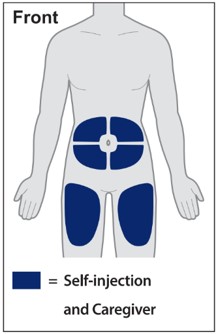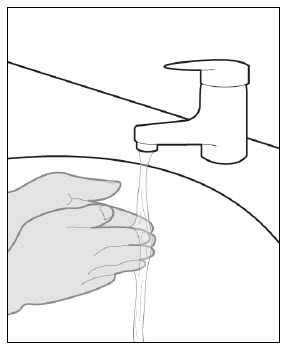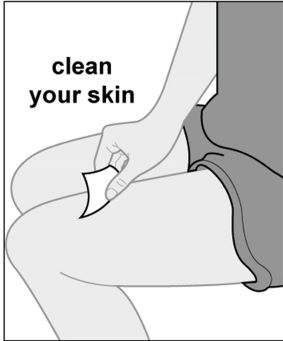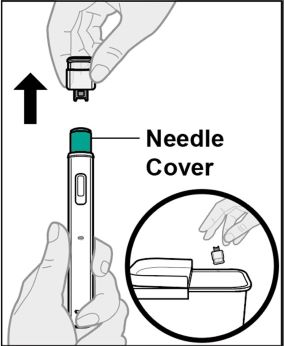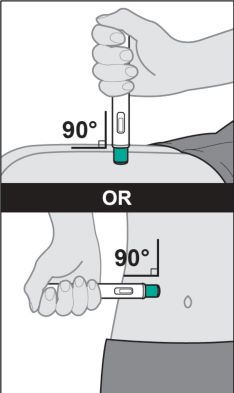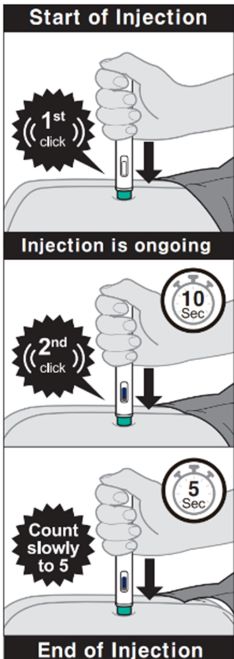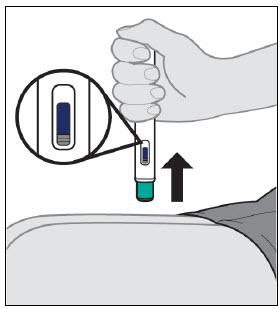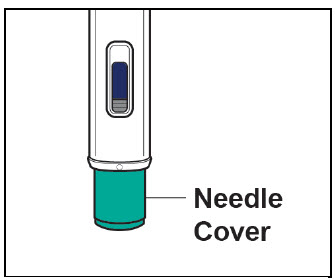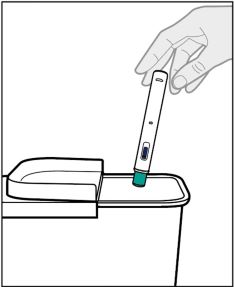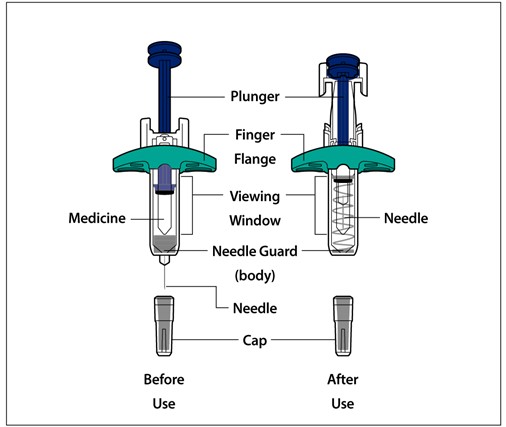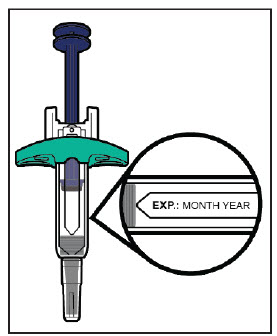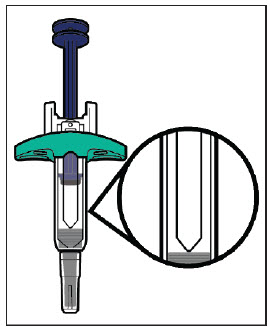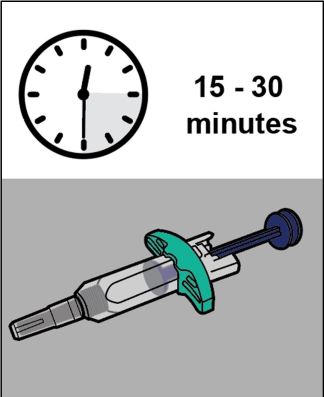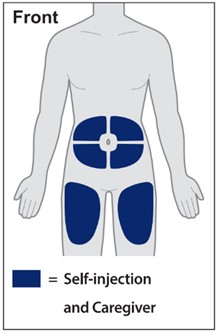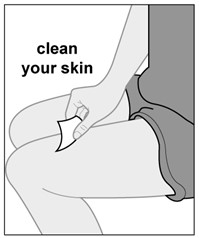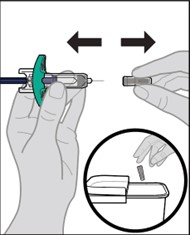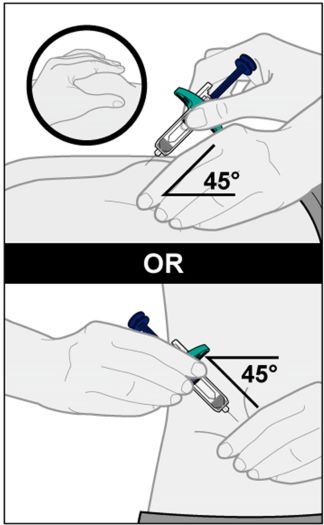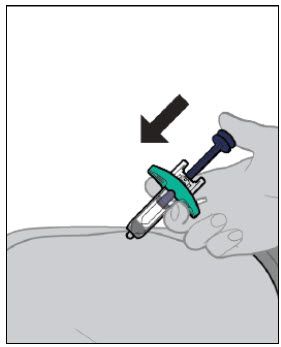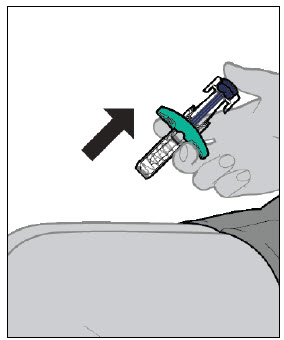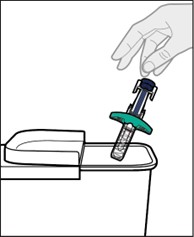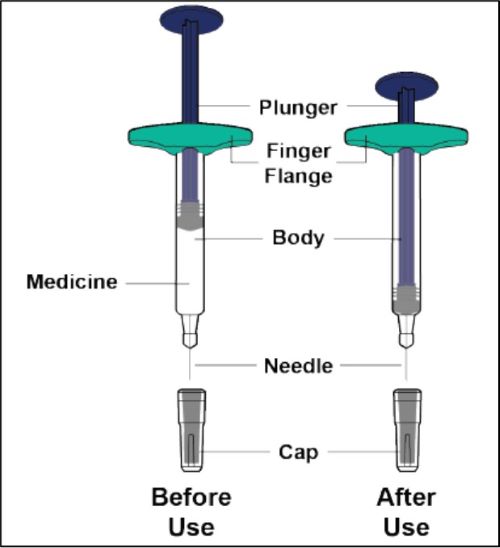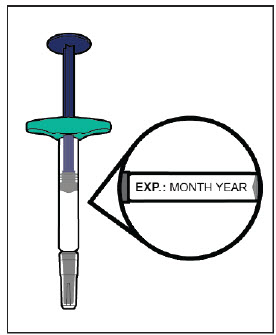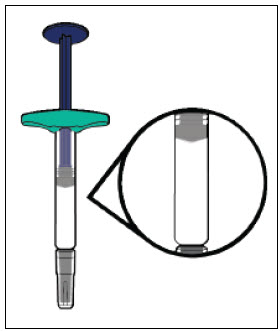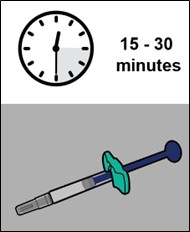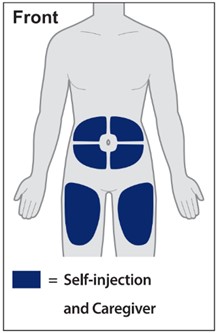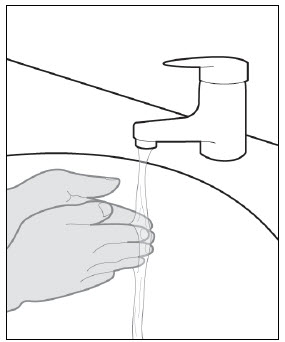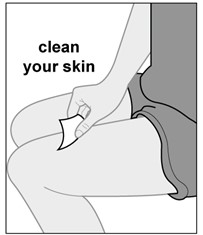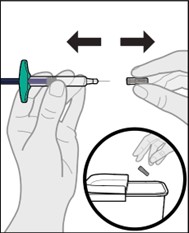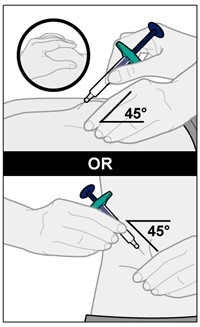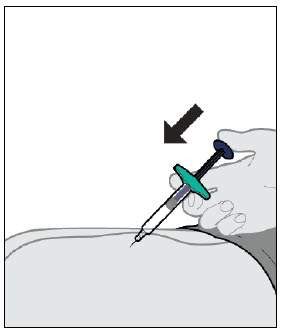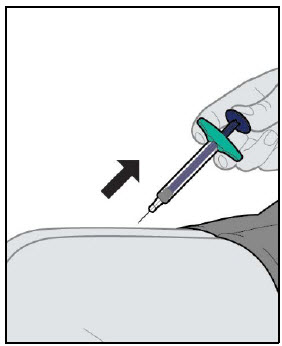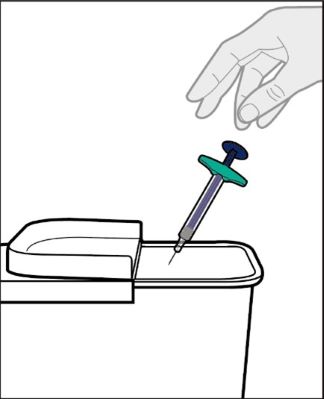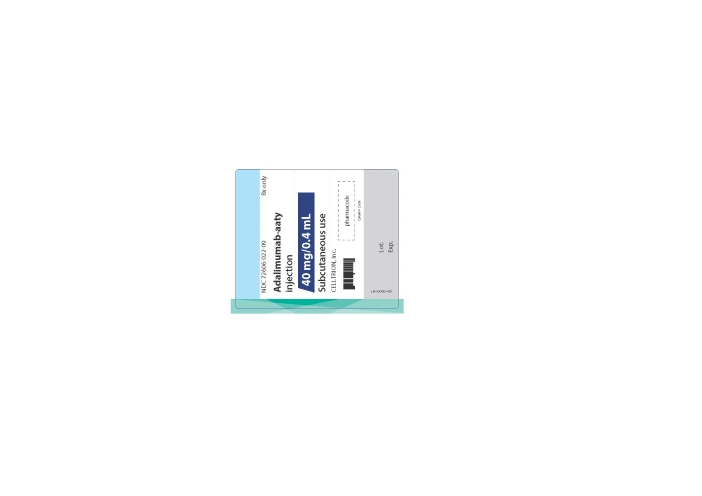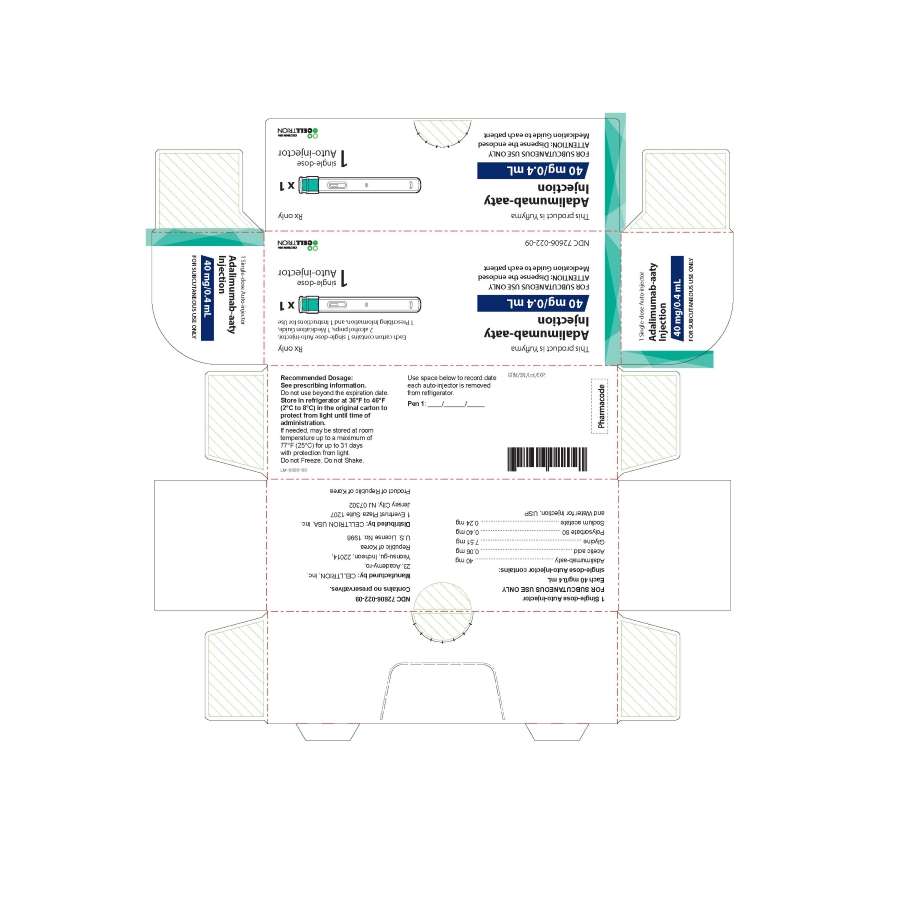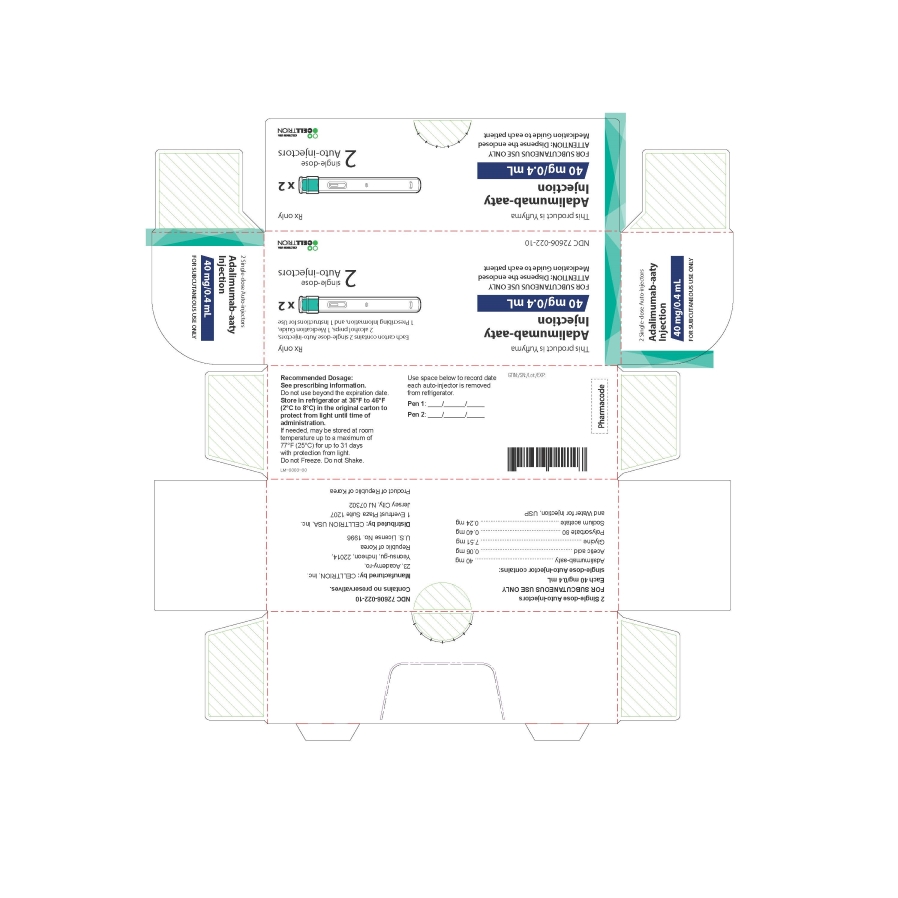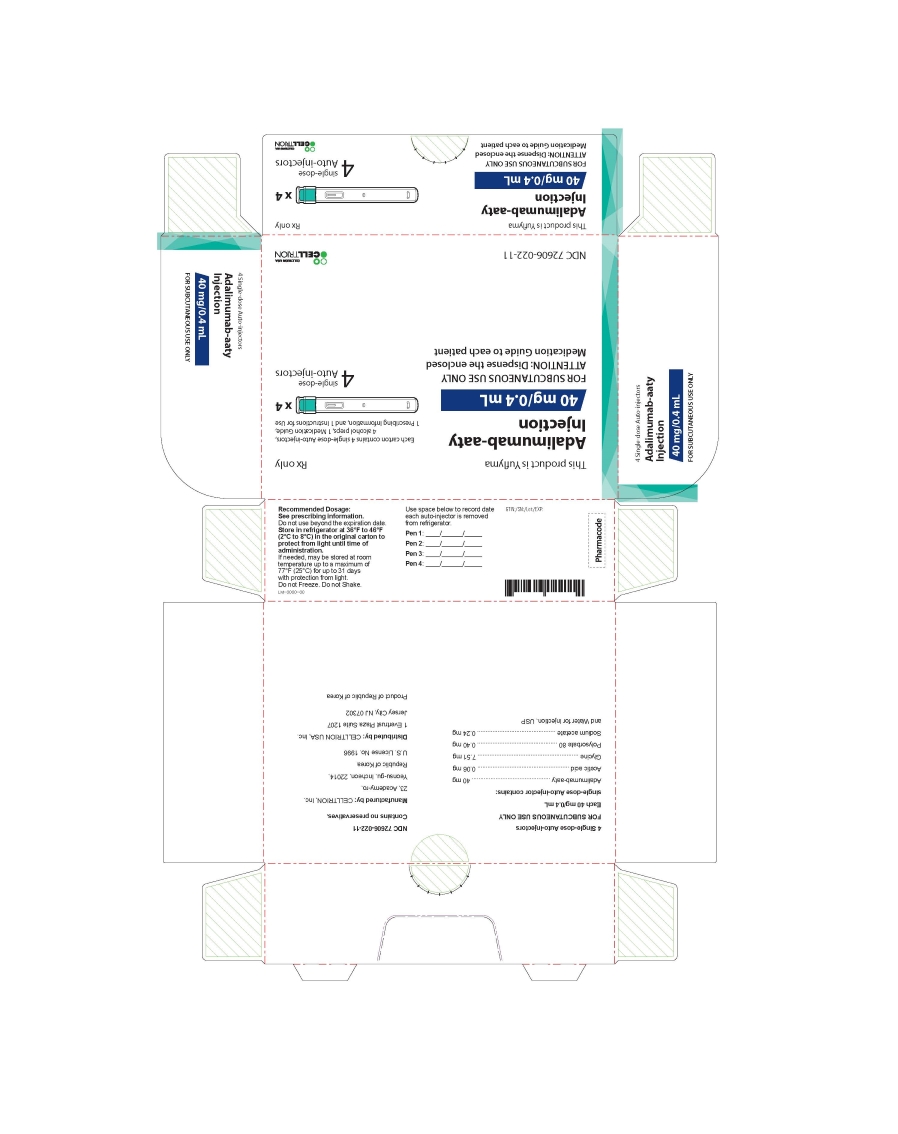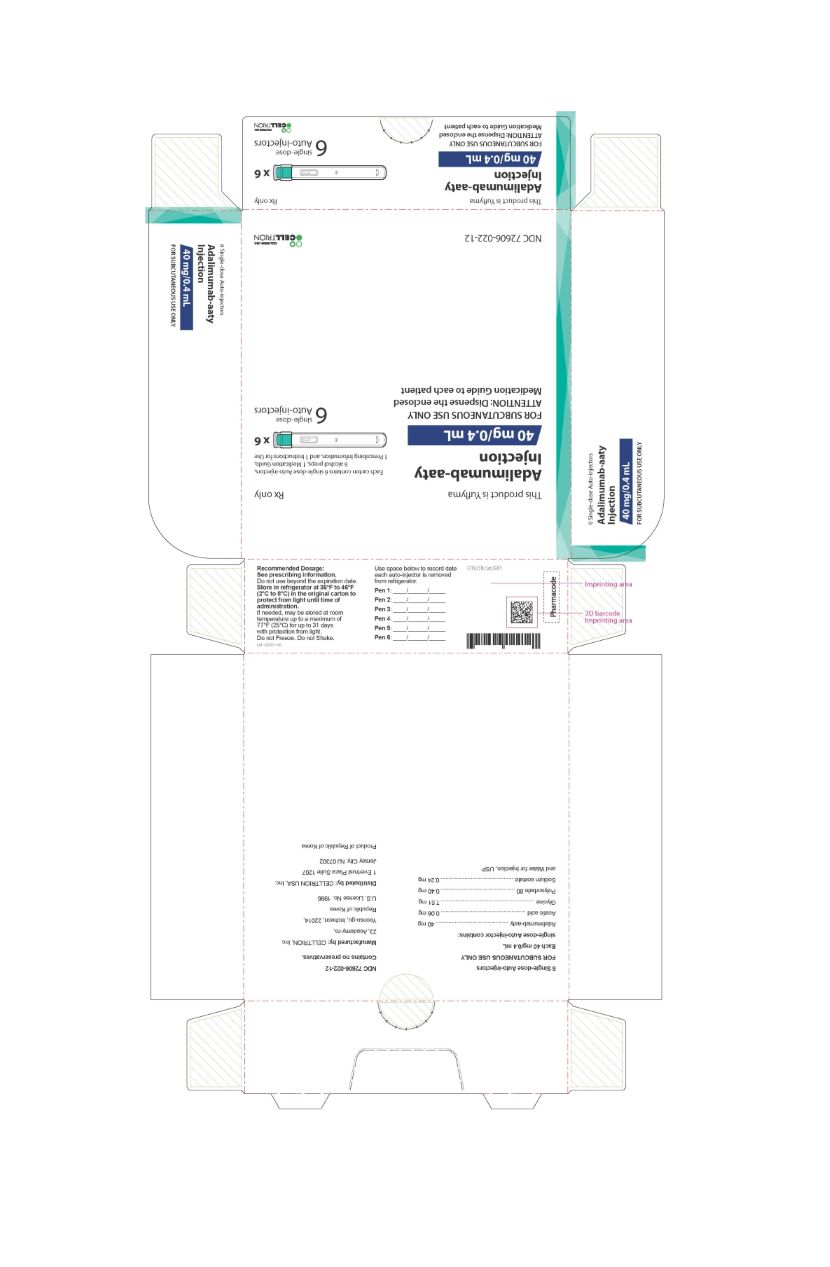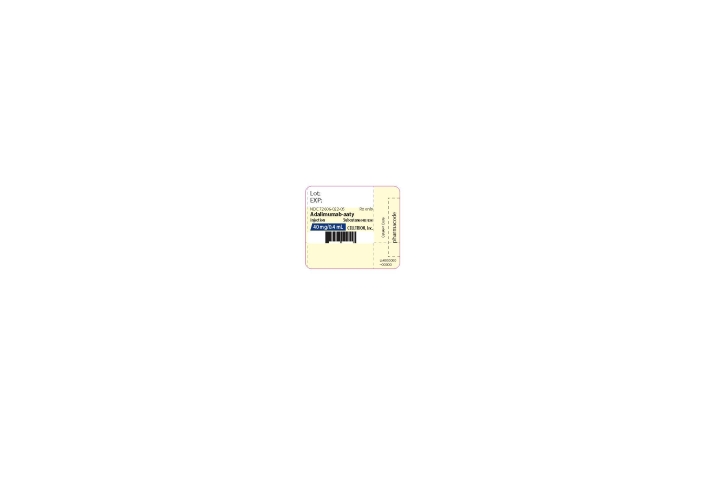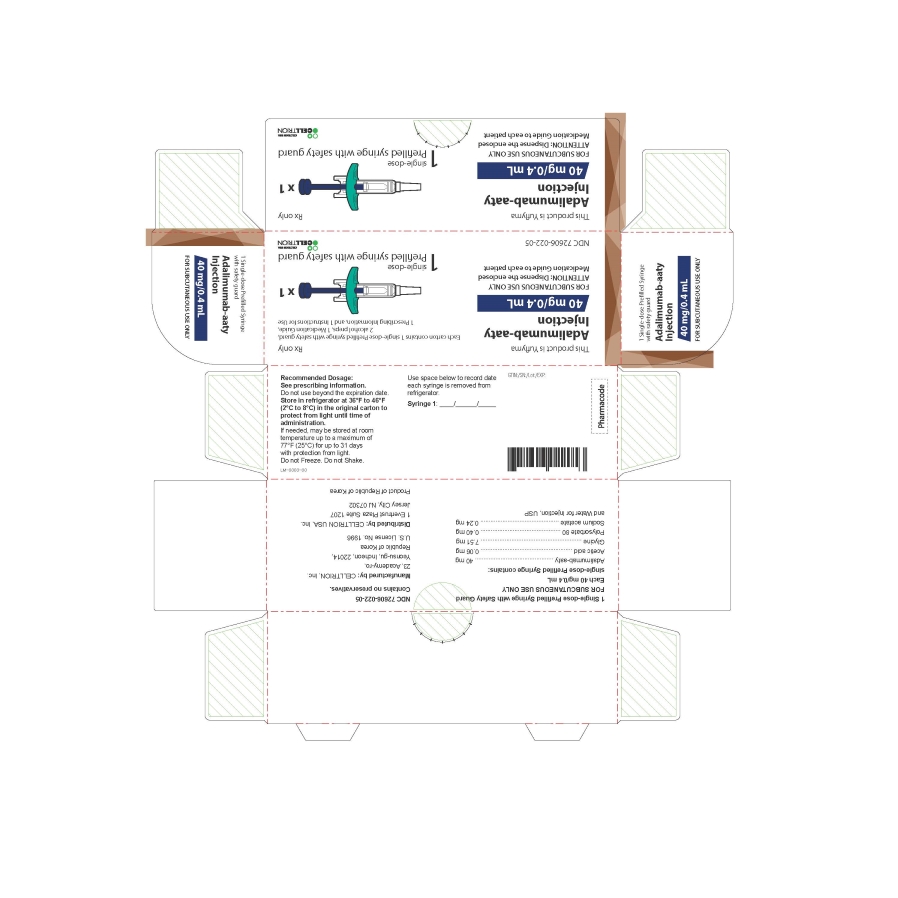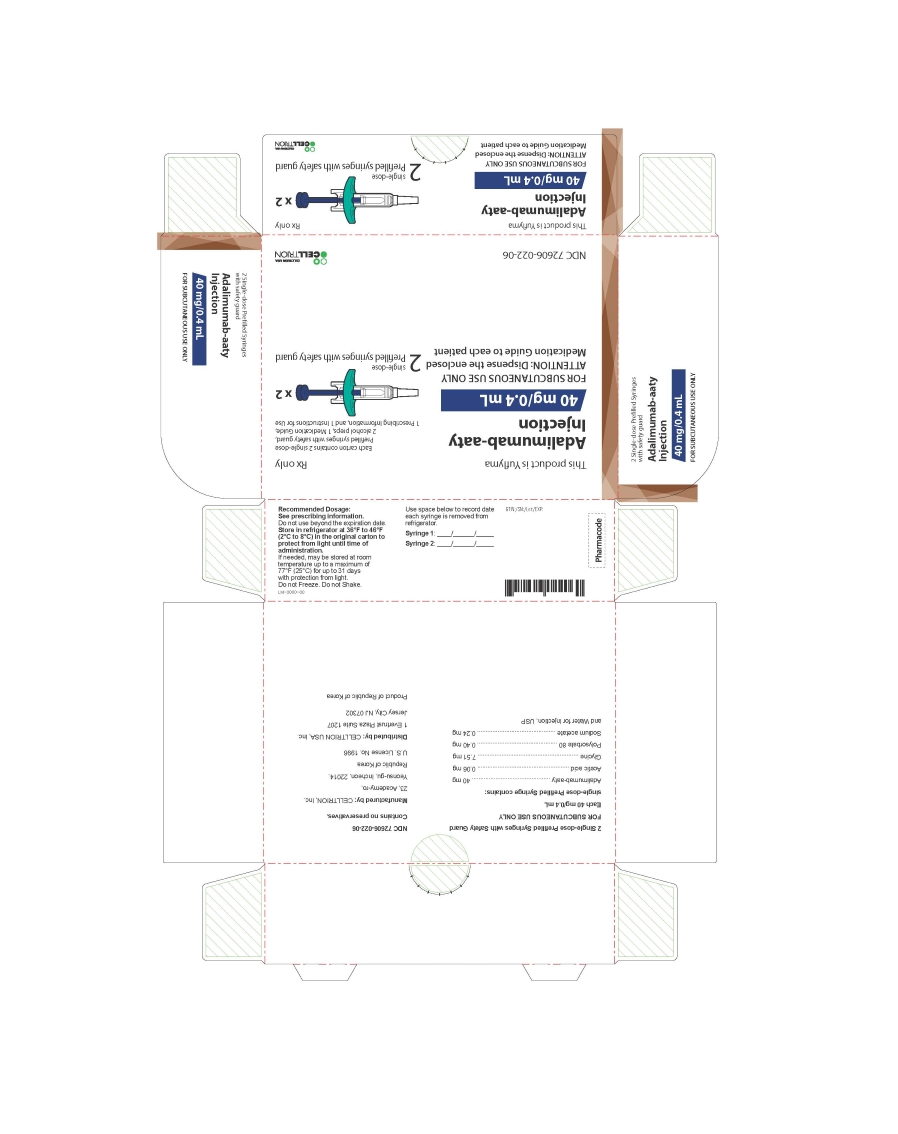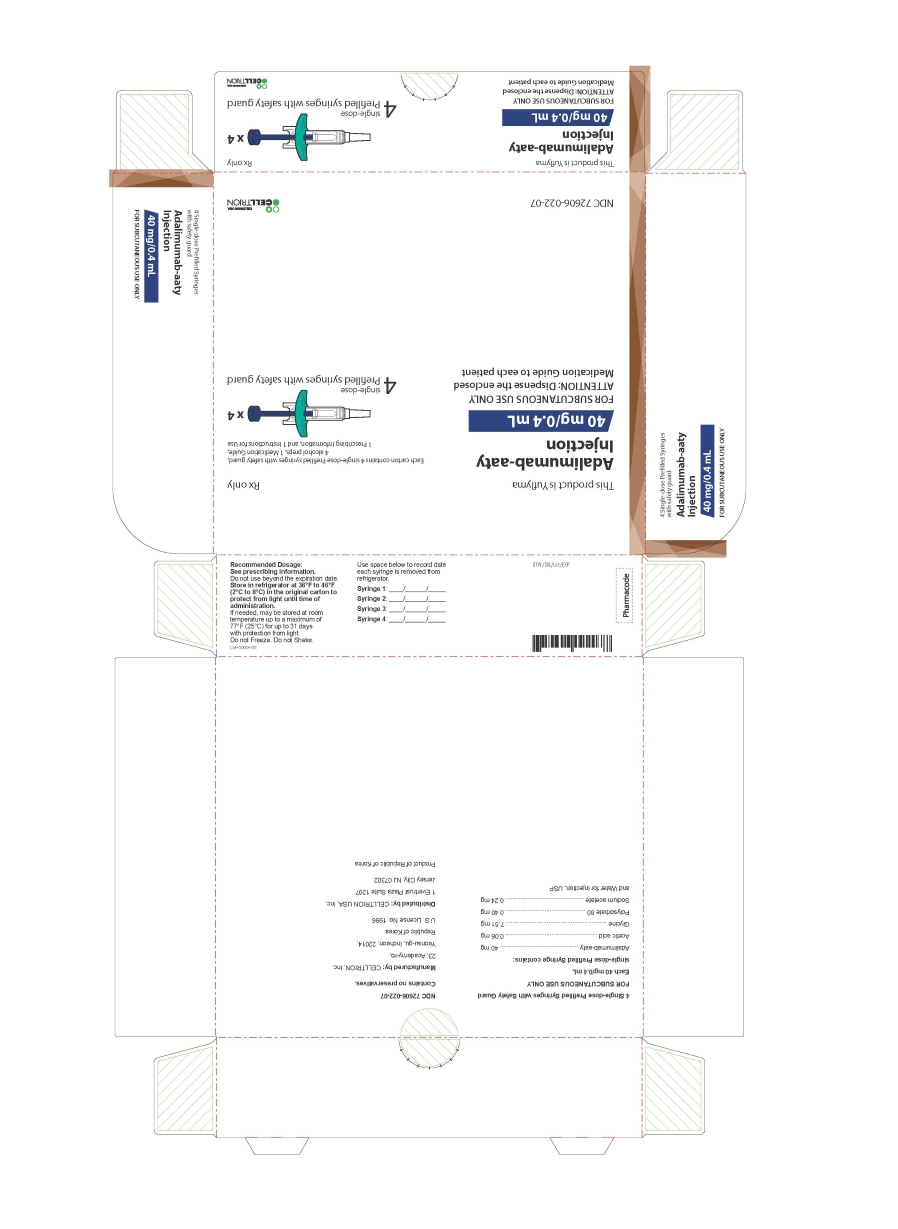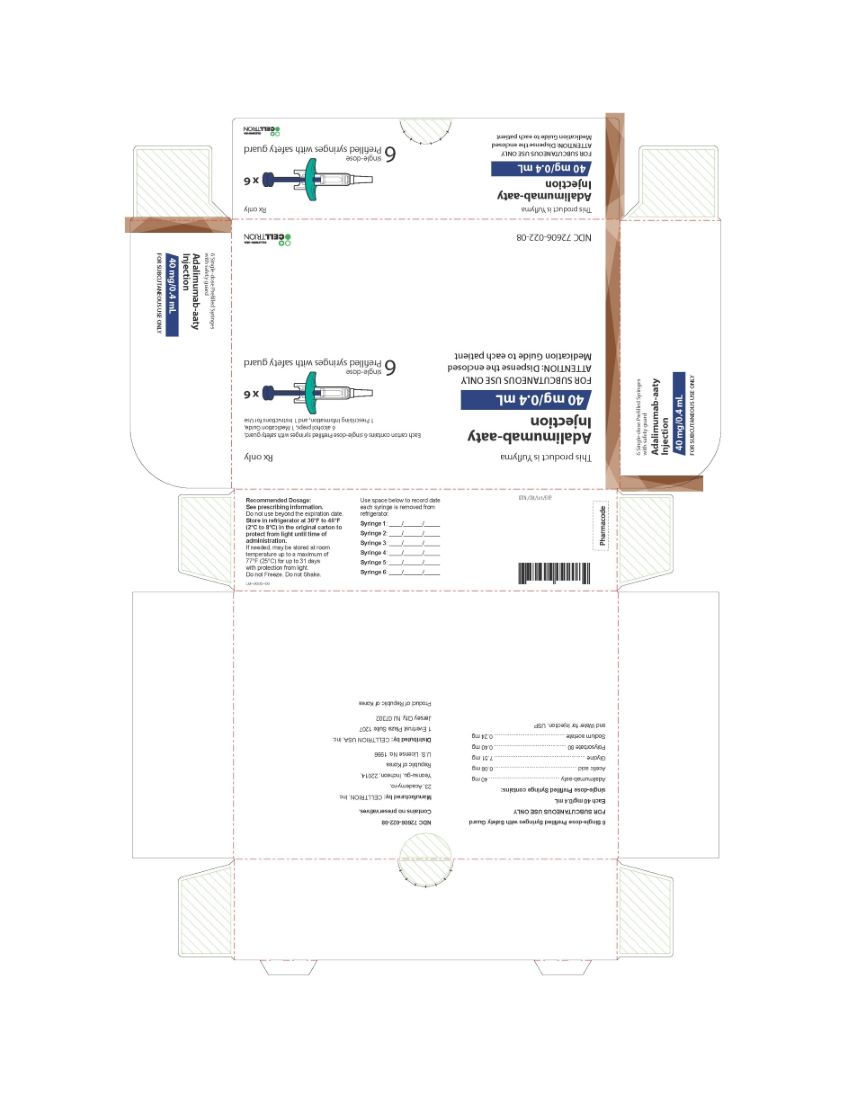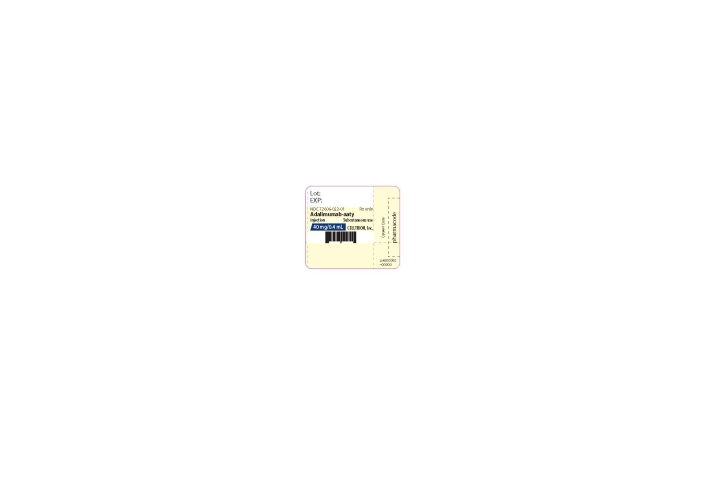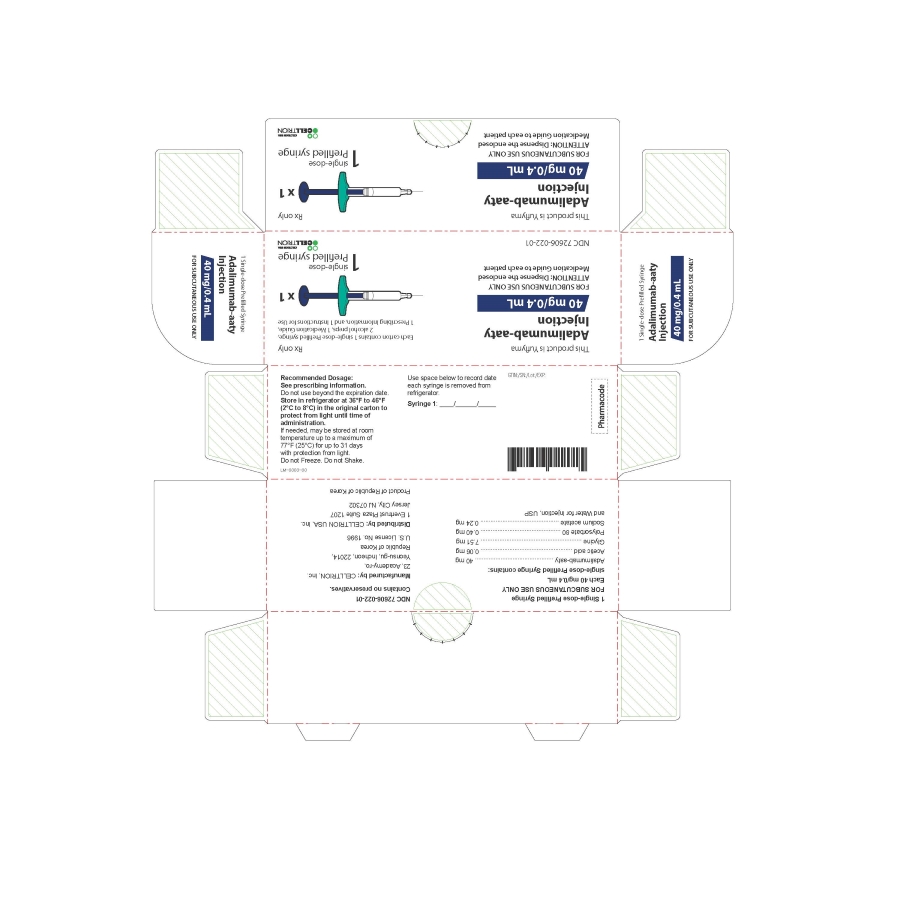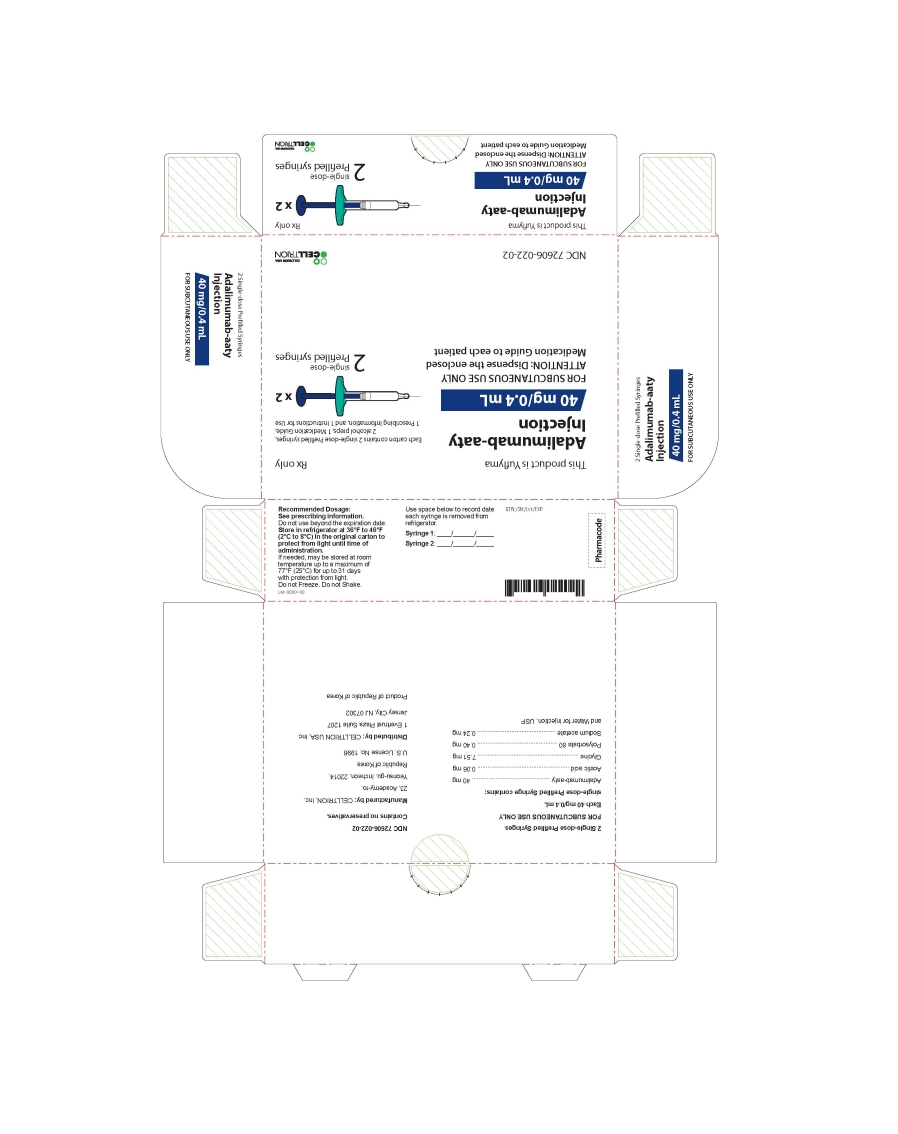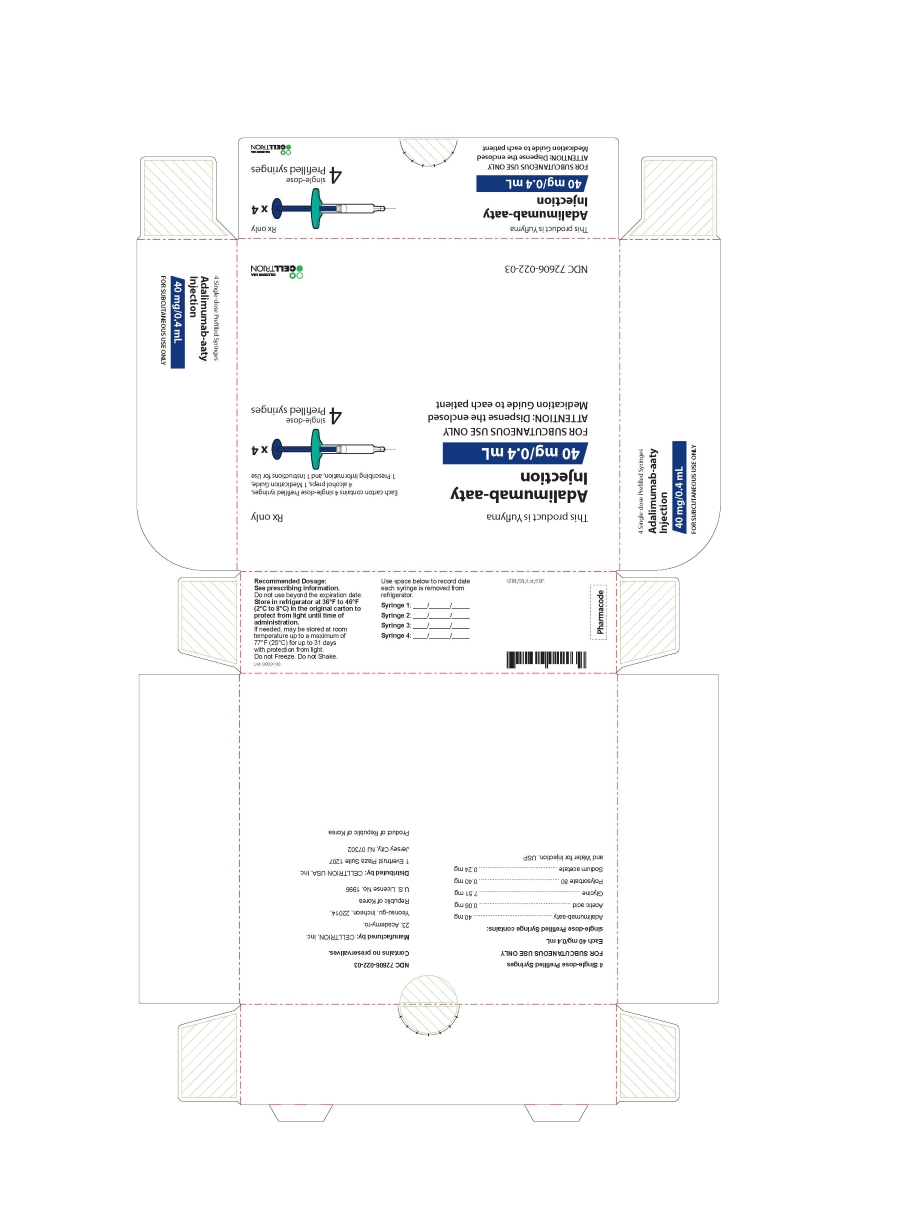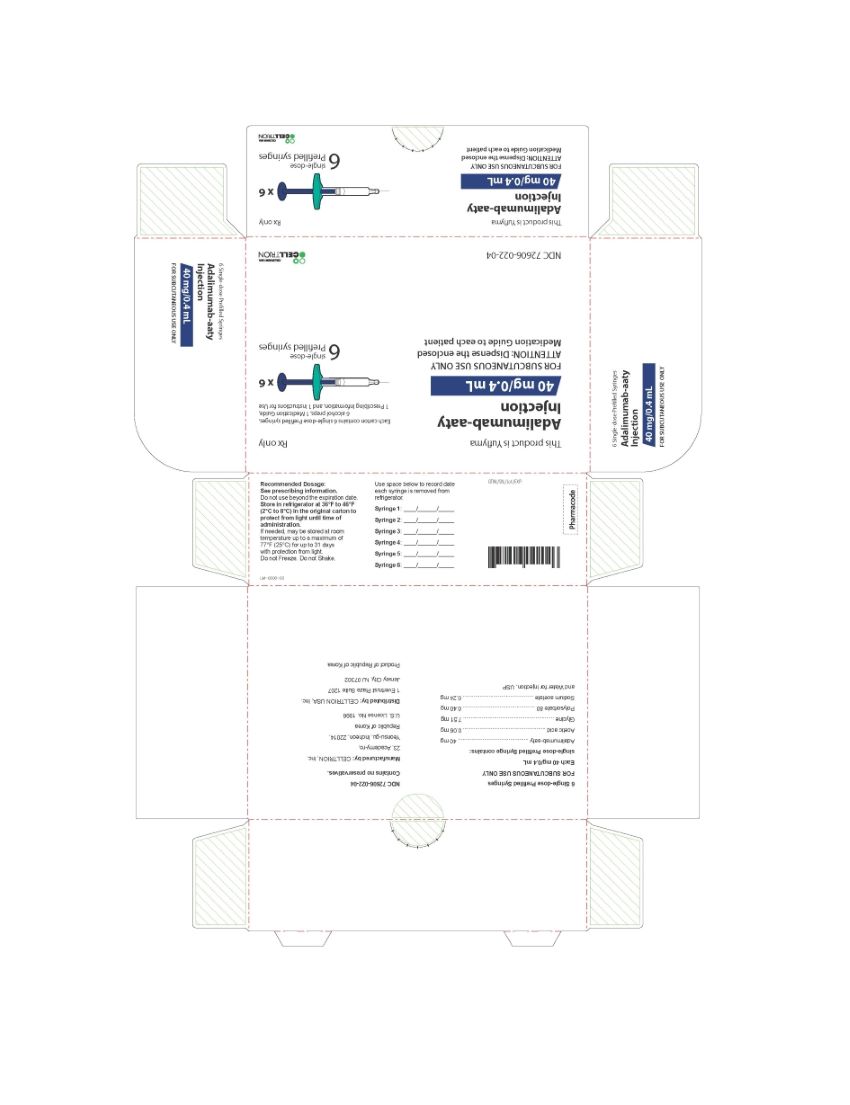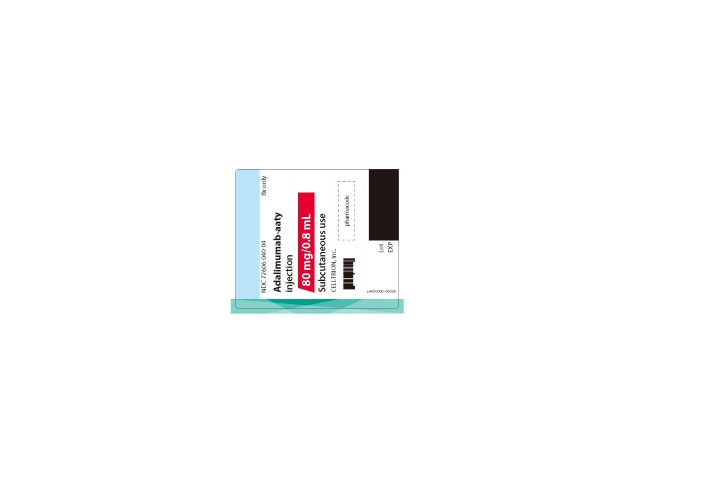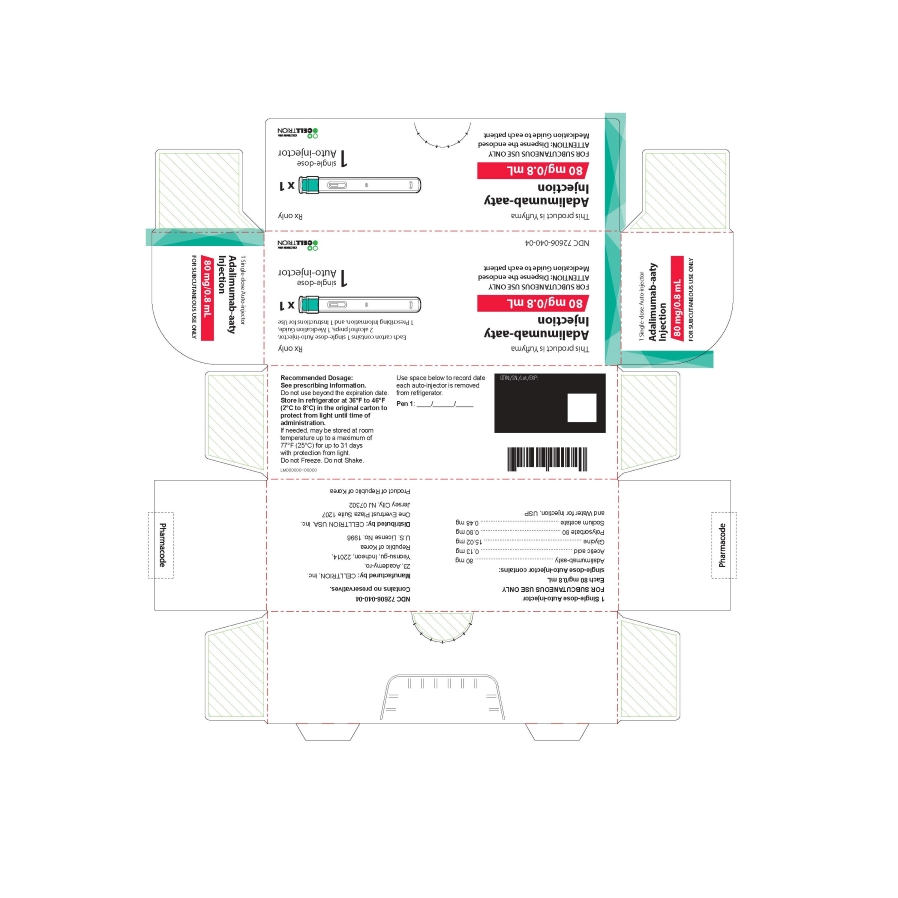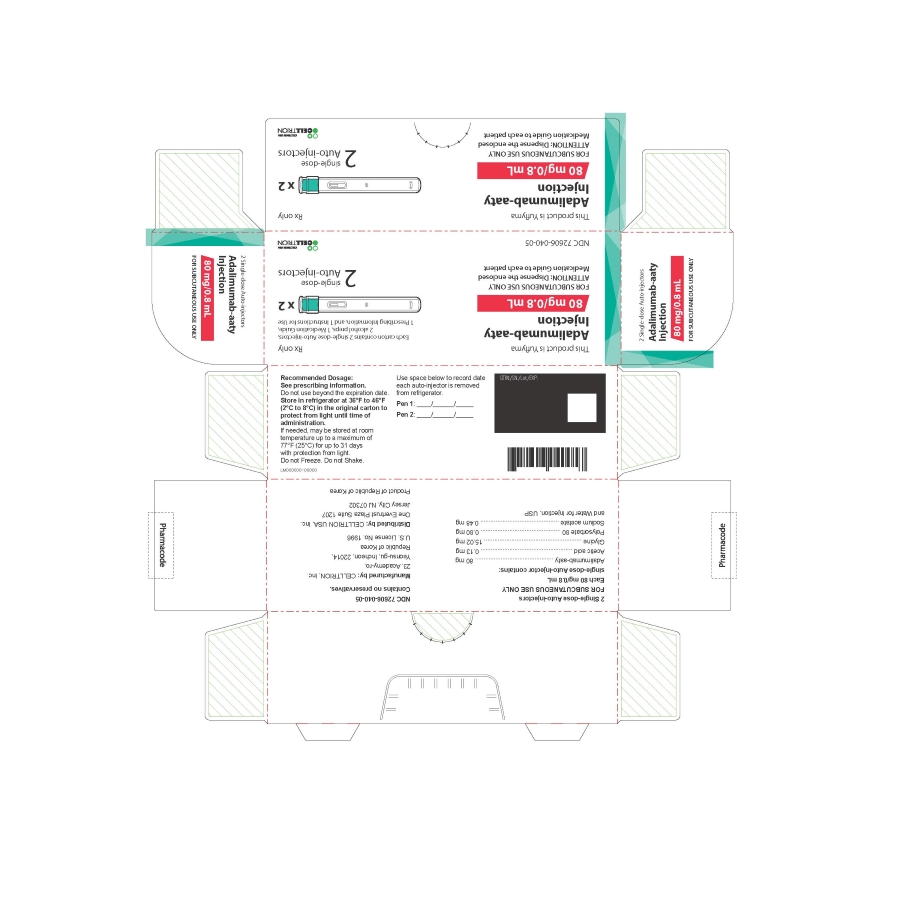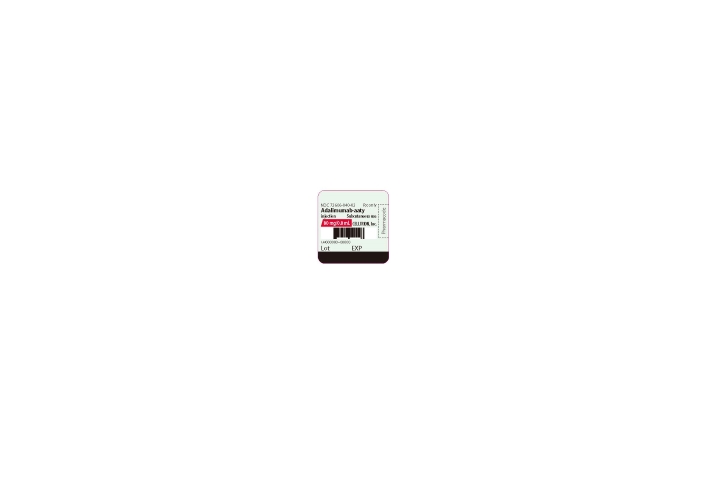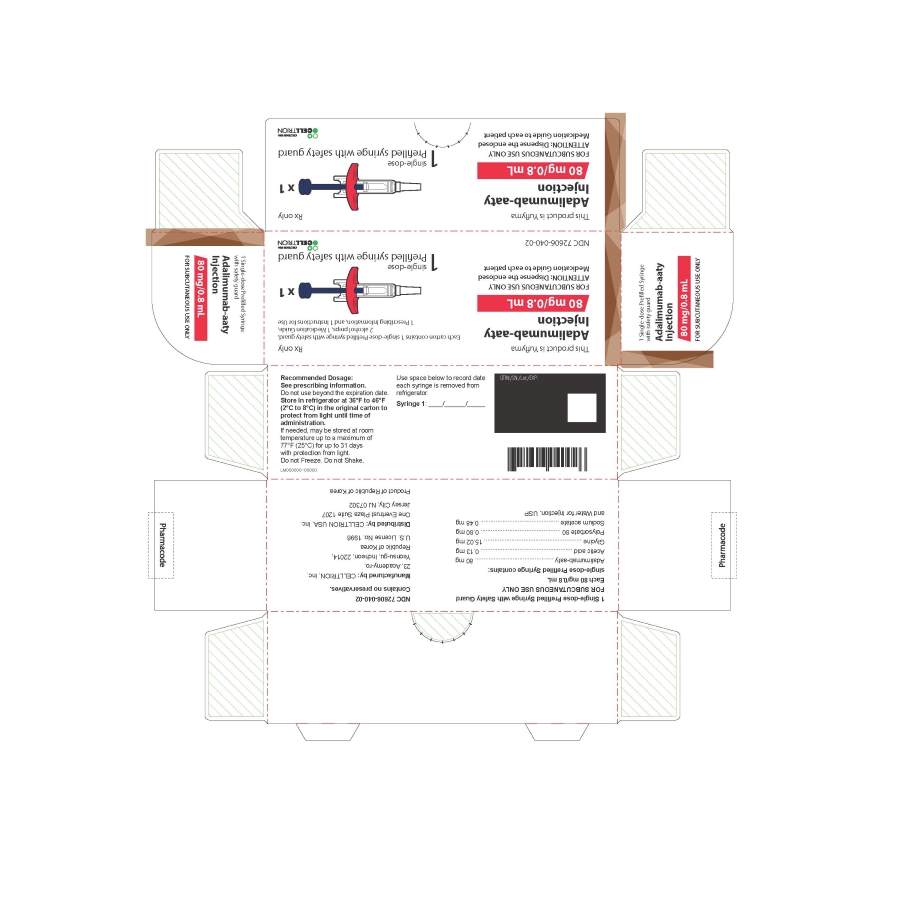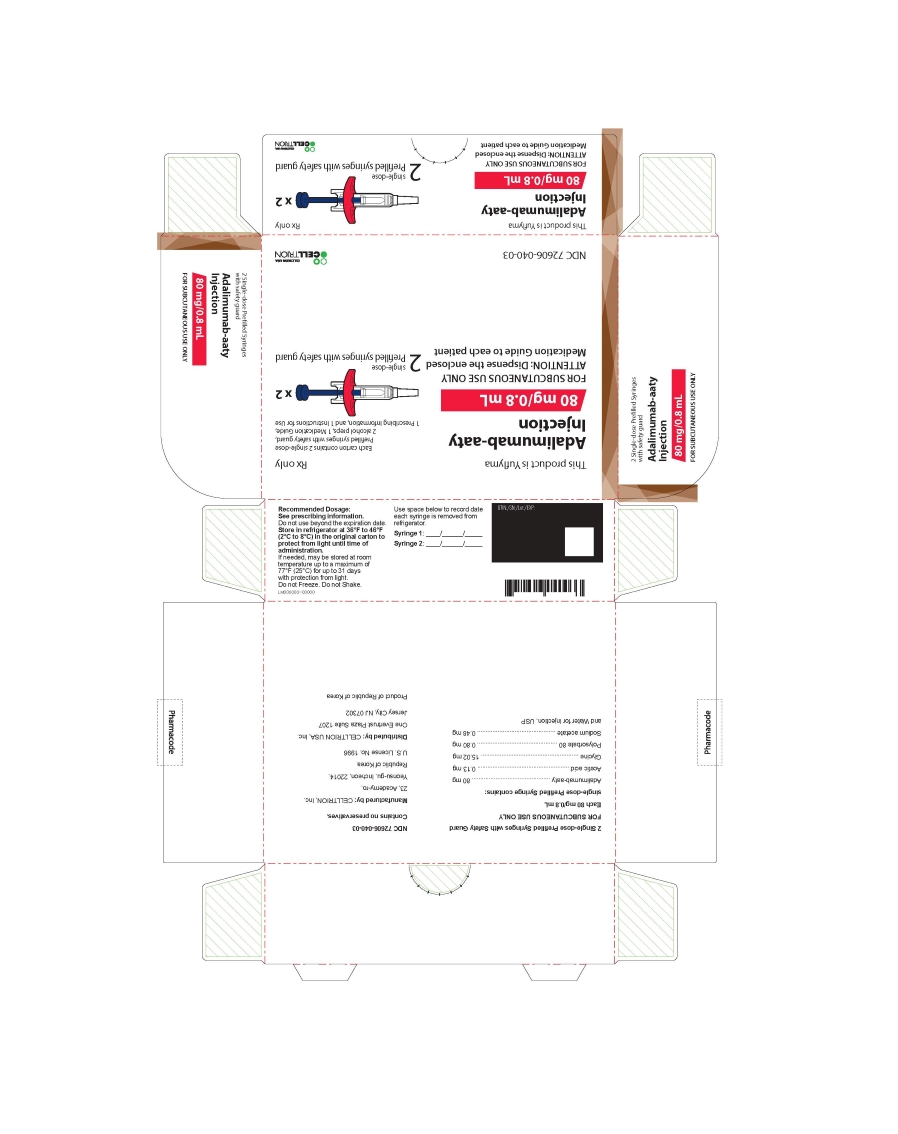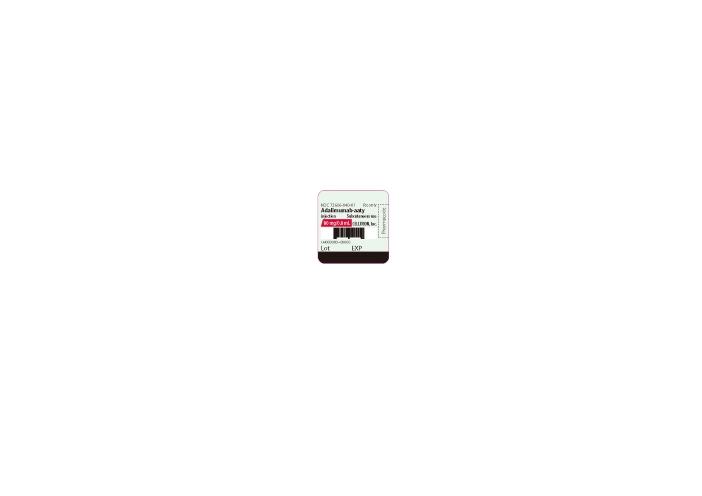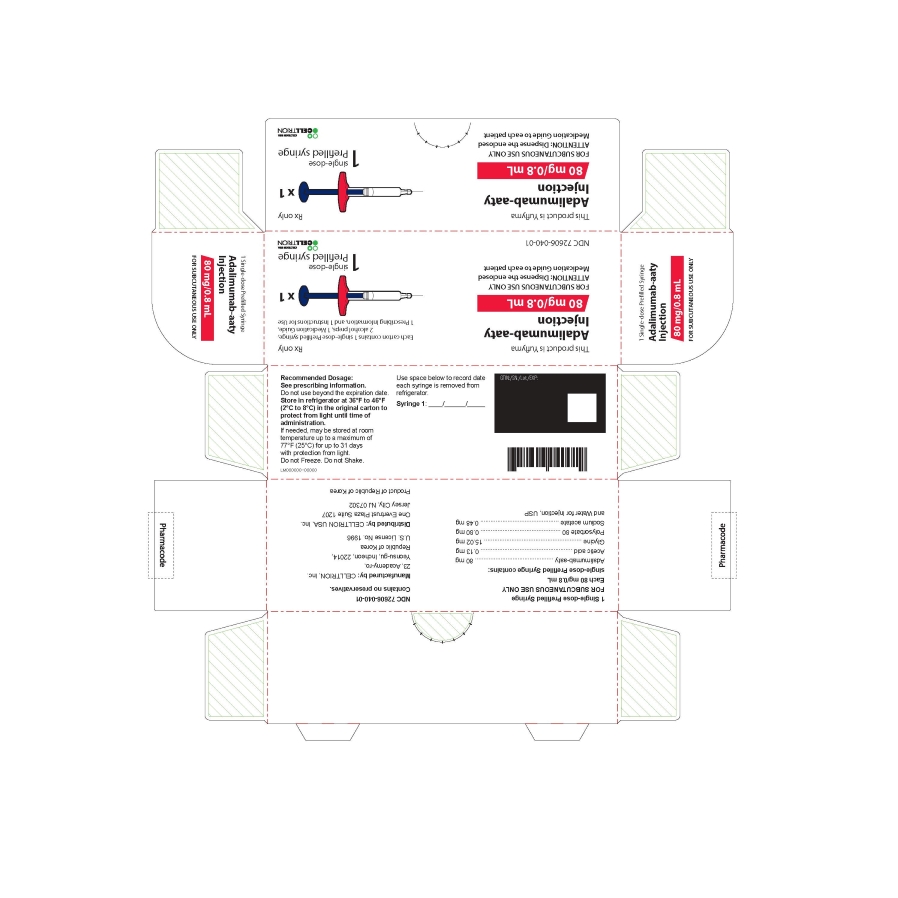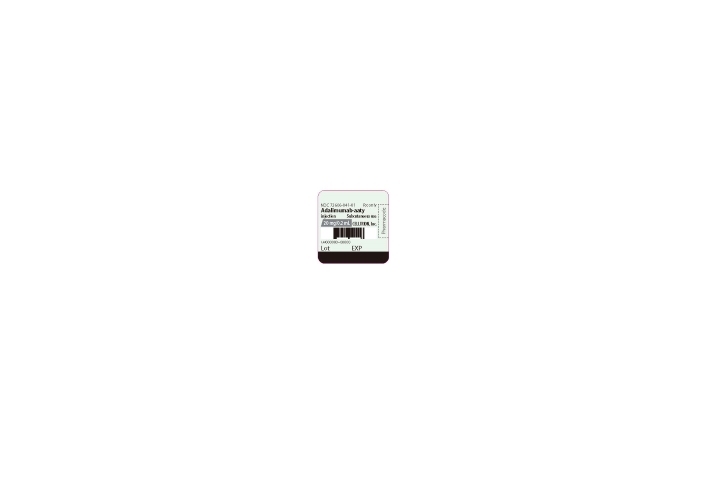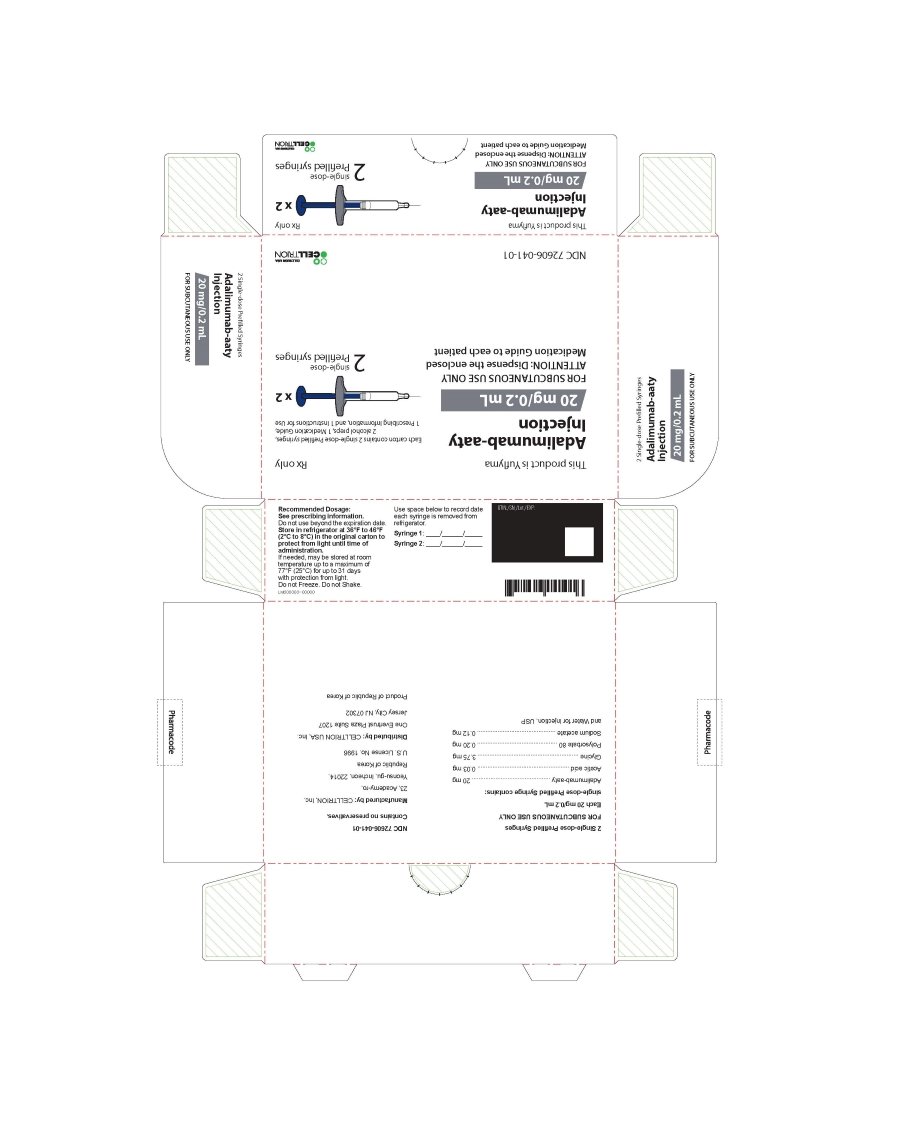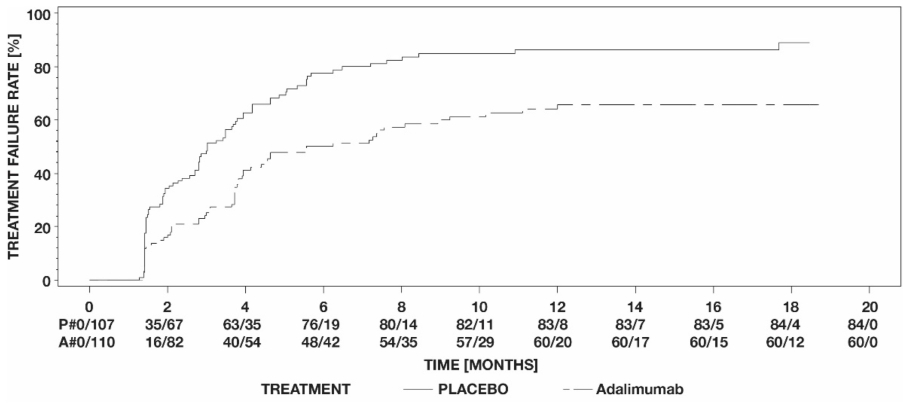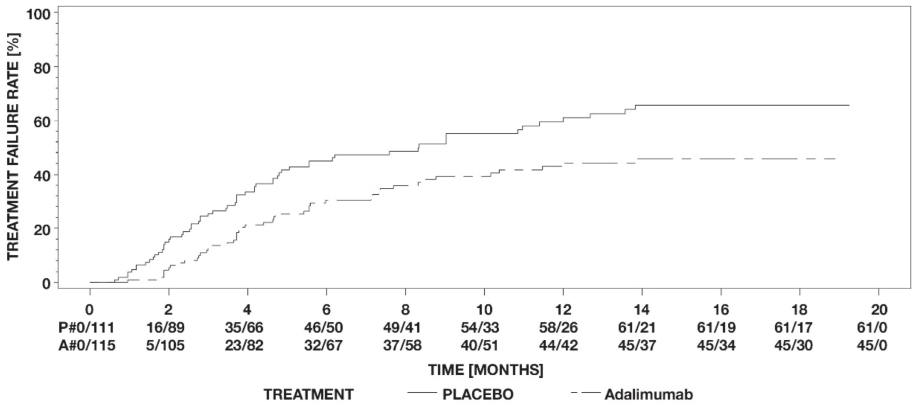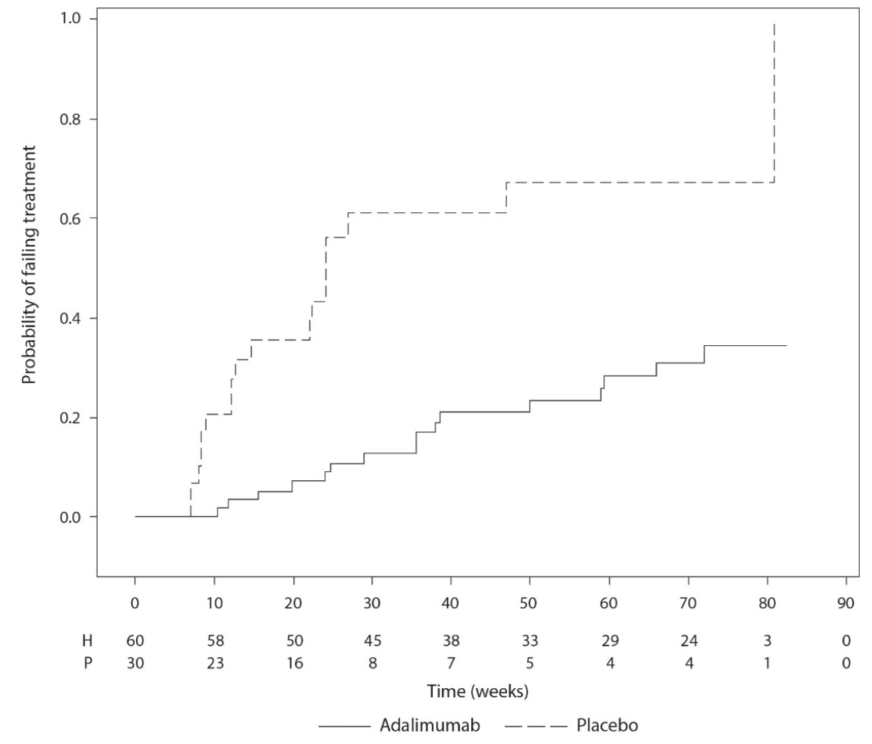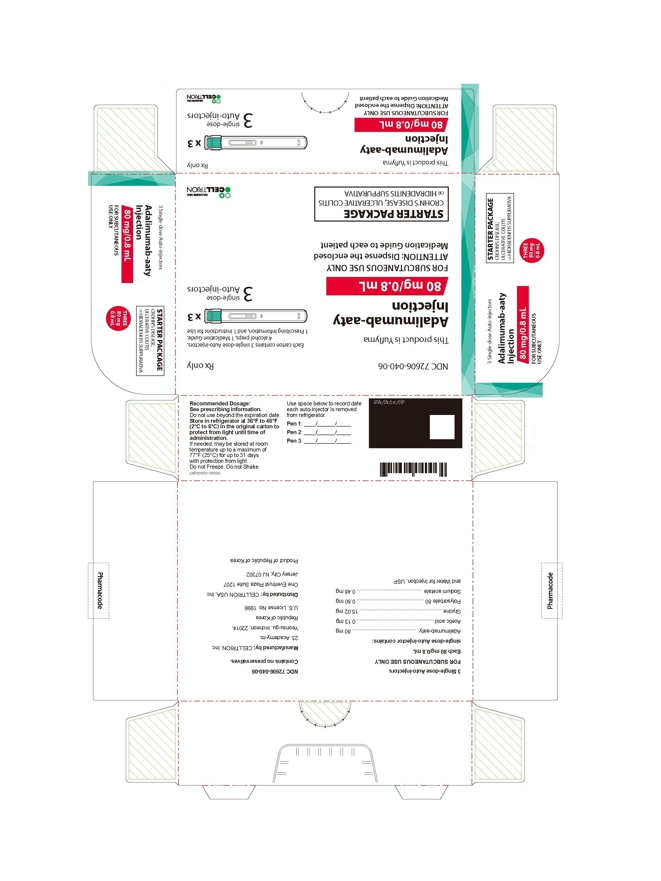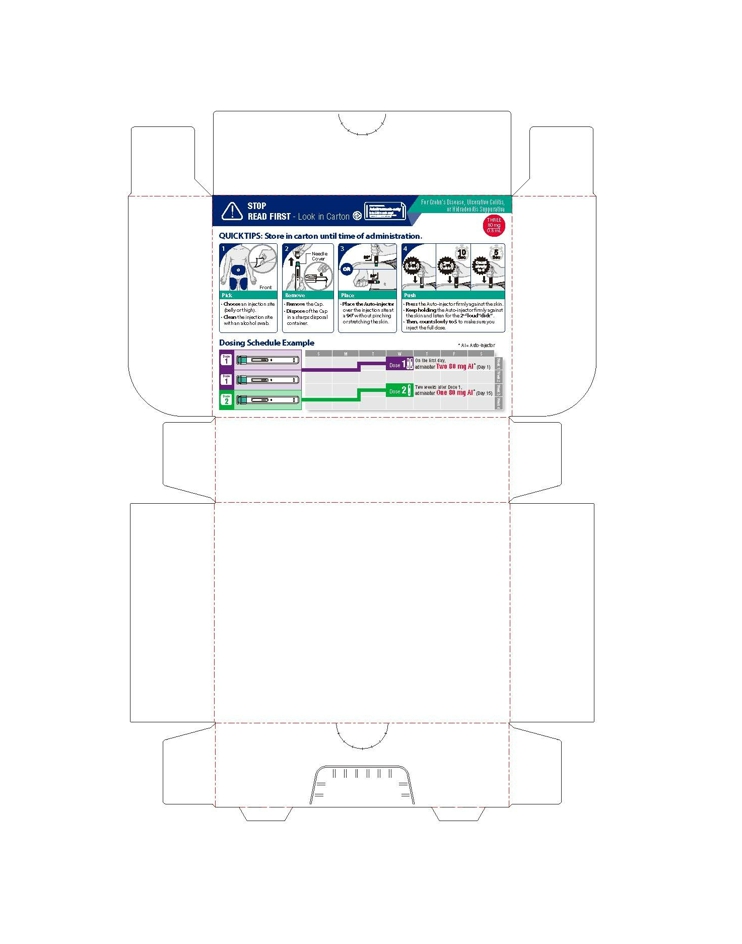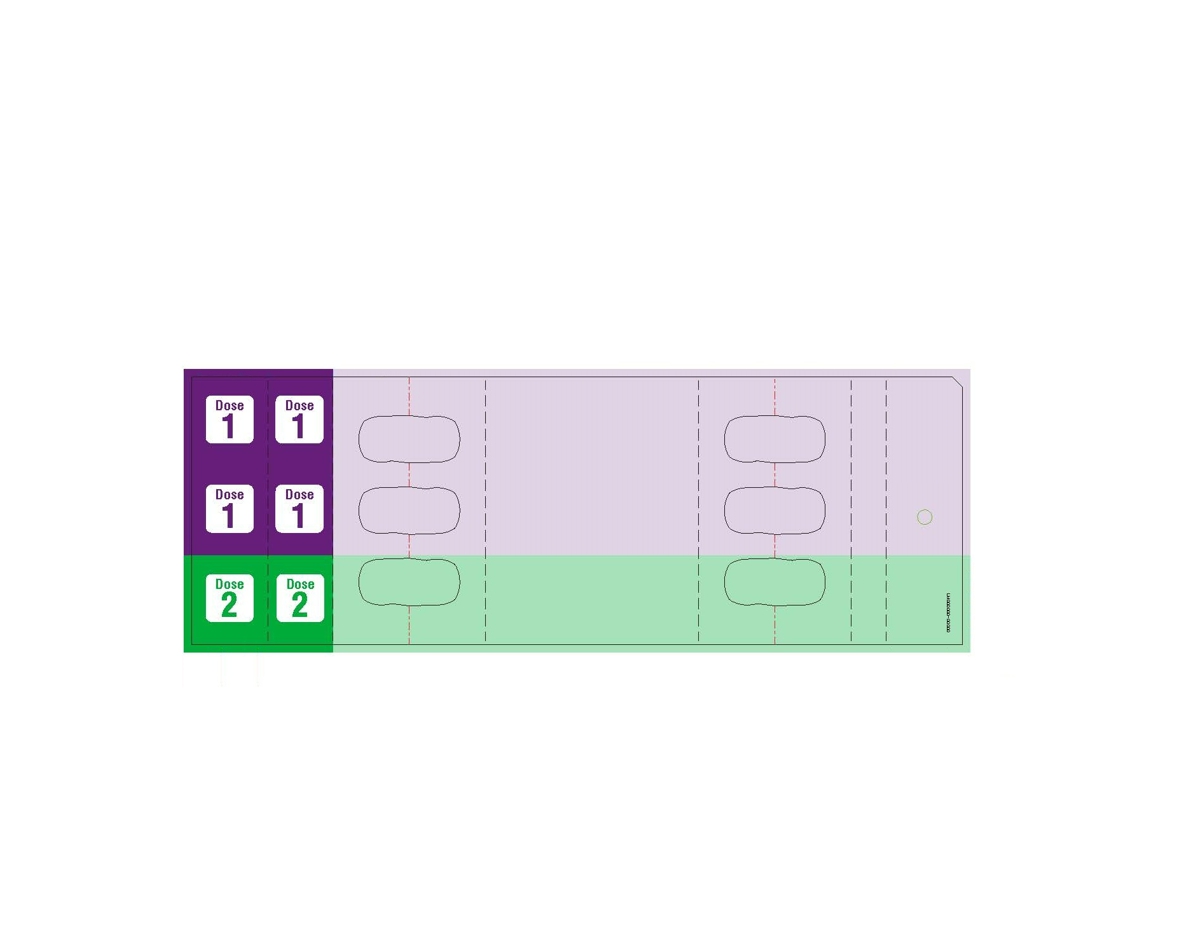 DRUG LABEL: Adalimumab
NDC: 72606-022 | Form: KIT | Route: SUBCUTANEOUS
Manufacturer: CELLTRION USA, Inc.
Category: prescription | Type: HUMAN PRESCRIPTION DRUG LABEL
Date: 20251028

ACTIVE INGREDIENTS: adalimumab-aaty 40 mg/0.4 mL; isopropyl alcohol 0.70 mL/1 mL
INACTIVE INGREDIENTS: water; water

HIGHLIGHTS OF PRESCRIBING INFORMATION

These highlights do not include all the information needed to use ADALIMUMAB-AATY safely and effectively. See full prescribing information for ADALIMUMAB-AATY.
ADALIMUMAB-AATY injection, for subcutaneous use
Initial U.S. Approval: 2023
This product is YUFLYMA (adalimumab-aaty). Adalimumab-aaty is biosimilar* to HUMIRA (adalimumab).

WARNING: SERIOUS INFECTIONS and MALIGNANCY

See full prescribing information for complete boxed warning.

SERIOUS INFECTIONS (5.1, 6.1):

- Increased risk of serious infections leading to hospitalization or death, including tuberculosis (TB), bacterial sepsis, invasive fungal infections (such as histoplasmosis), and infections due to other opportunistic pathogens.
- Discontinue Adalimumab-aaty if a patient develops a serious infection or sepsis during treatment.
- Perform test for latent TB; if positive, start treatment for TB prior to starting Adalimumab-aaty.
- Monitor all patients for active TB during treatment, even if initial latent TB test is negative.

MALIGNANCY (5.2):

- Lymphoma and other malignancies, some fatal, have been reported in children and adolescent patients treated with TNF blockers including adalimumab products.
- Post-marketing cases of hepatosplenic T-cell lymphoma (HSTCL), a rare type of T-cell lymphoma, have occurred in adolescent and young adults with inflammatory bowel disease treated with TNF blockers including adalimumab products.

RECENT MAJOR CHANGES

Indications and Usage, Hidradenitis Suppurativa (1.8) | 10/2025
Indications and Usage, Uveitis (1.9) | 10/2025
Dosage and Administration, Recommended Dosage in Juvenile Idiopathic Arthritis or Pediatric Uveitis (2.3) | 10/2025
Dosage and Administration, Recommended Dosage in Hidradenitis Suppurativa (2.7) | 10/2025
Warnings and Precautions, Autoimmunity (5.9) | 10/2025

1 INDICATIONS AND USAGE

Adalimumab-aaty is a tumor necrosis factor (TNF) blocker indicated for:

- Reducing signs and symptoms, inducing major clinical response, inhibiting the progression of structural damage, and improving physical function in adult patients with moderately to severely active rheumatoid arthritis. (1.1)
- Reducing signs and symptoms of moderately to severely active polyarticular juvenile idiopathic arthritis in patients 2 years of age and older. (1.2)
- Reducing signs and symptoms, inhibiting the progression of structural damage, and improving physical function in adult patients with active psoriatic arthritis. (1.3)
- Reducing signs and symptoms in adult patients with active ankylosing spondylitis. (1.4)
- Treatment of moderately to severely active Crohn's disease in adults and pediatric patients 6 years of age and older. (1.5)
- Treatment of moderately to severely active ulcerative colitis in adult patients. (1.6)
  Limitations of Use: Effectiveness has not been established in patients who have lost response to or were intolerant to TNF blockers.
- Treatment of adult patients with moderate to severe chronic plaque psoriasis who are candidates for systemic therapy or phototherapy, and when other systemic therapies are medically less appropriate. (1.7)
- Treatment of moderate to severe hidradenitis suppurativa in patients 12 years of age and older. (1.8)
- Treatment of non-infectious intermediate, posterior, and panuveitis in adults and pediatric patients 2 years of age and older. (1.9)

2 DOSAGE AND ADMINISTRATION

- Administer by subcutaneous injection (2)

Rheumatoid Arthritis, Psoriatic Arthritis, Ankylosing Spondylitis (2.2):

- Adults:40 mg every other week.
  - Some patients with RA not receiving methotrexate may benefit from increasing the dosage to 40 mg every week or 80 mg every other week.

Juvenile Idiopathic Arthritis or Pediatric Uveitis (2.3):

Pediatric Weight 2 Years of Age and Older | Recommended Dosage
15 kg (33 lbs) to less than 30 kg (66 lbs) | 20 mg every other week
30 kg (66 lbs) and greater | 40 mg every other week

Crohn's Disease (2.4):

- Adults: 160 mg on Day 1 (given in one day or split over two consecutive days); 80 mg on Day 15; and 40 mg every other week starting on Day 29.
- Pediatric Patients 6 Years of Age and Older:

Pediatric Weight | Recommended Dosage
Pediatric Weight | Days 1 and 15 | Starting on Day 29
17 kg (37 lbs) to less than 40 kg (88 lbs) | Day 1: 80 mg Day 15: 40 mg | 20 mg every other week
40 kg (88 lbs) and greater | Day 1: 160 mg (single dose or split over two consecutive days) Day 15: 80 mg | 40 mg every other week

Ulcerative Colitis (2.5):

- Adults: 160 mg on Day 1 (given in one day or split over two consecutive days), 80 mg on Day 15 and 40 mg every other week starting on Day 29. Discontinue in patients without evidence of clinical remission by eight weeks (Day 57).

Plaque Psoriasis or Adult Uveitis (2.6):

- Adults: 80 mg initial dose followed by 40 mg every other week starting one week after initial dose.

Hidradenitis Suppurativa (2.7):

- Adults:
  - Day 1: 160 mg (given in one day or split over two consecutive days)
  - Day 15: 80 mg
  - Day 29 and subsequent doses: 40 mg every week or 80 mg every other week
- Adolescents 12 years of age and older:

Adolescent Weight | Recommended Dosage
30 kg (66 lbs) to less than 60 kg (132 lbs) | Day 1: 80 mg Day 8 and subsequent doses: 40 mg every other week
60 kg (132 lbs) and greater | Day 1: 160 mg (given in one day or split over two consecutive days) Day 15: 80 mg Day 29 and subsequent doses: 40 mg every week or 80 mg every other week

3 DOSAGE FORMS AND STRENGTHS

Injection:

- Single-dose prefilled auto-injector (Adalimumab-aaty AI): 80 mg/0.8 mL, 40 mg/0.4 mL (3)
- Single-dose prefilled syringe with safety guard : 80 mg/0.8 mL, 40 mg/0.4 mL (3)
- Single-dose prefilled syringe: 80 mg/0.8 mL, 40 mg/0.4 mL, 20 mg/0.2 mL (3)

4 CONTRAINDICATIONS

None (4)

5 WARNINGS AND PRECAUTIONS

- Serious infections: Do not start Adalimumab-aaty during an active infection. If an infection develops, monitor carefully, and stop Adalimumab-aaty if infection becomes serious (5.1)
- Invasive fungal infections: For patients who develop a systemic illness on Adalimumab-aaty, consider empiric antifungal therapy for those who reside or travel to regions where mycoses are endemic (5.1)
- Malignancies: Incidence of malignancies was greater in adalimumab-treated patients than in controls (5.2)
- Anaphylaxis or serious hypersensitivity reactions may occur (5.3)
- Hepatitis B virus reactivation: Monitor HBV carriers during and several months after therapy. If reactivation occurs, stop Adalimumab-aaty and begin anti-viral therapy (5.4)
- Demyelinating disease: Exacerbation or new onset, may occur (5.5)
- Cytopenias, pancytopenia: Advise patients to seek immediate medical attention if symptoms develop, and consider stopping Adalimumab-aaty (5.6)
- Heart failure: Worsening or new onset, may occur (5.8)
- Autoimmunity: Stop Adalimumab-aaty if lupus-like syndrome or autoimmune hepatitis develop (5.9)

6 ADVERSE REACTIONS

Most common adverse reactions (> 10%) are: infections (e.g. upper respiratory, sinusitis), injection site reactions, headache and rash (6.1)

To report SUSPECTED ADVERSE REACTIONS, contact CELLTRION USA Inc., at 1-800-560-9414 or FDA at 1-800-FDA-1088 or www.fda.gov/medwatch.

7 DRUG INTERACTIONS

- Abatacept: Increased risk of serious infection (5.1, 5.11, 7.2)
- Anakinra: Increased risk of serious infection (5.1, 5.7, 7.2)
- Live vaccines: Avoid use with Adalimumab-aaty (5.10, 7.3)

FULL PRESCRIBING INFORMATION

WARNING: SERIOUS INFECTIONS and MALIGNANCY

SERIOUS INFECTIONS

Patients treated with adalimumab products, including Adalimumab-aaty, are at increased risk for developing serious infections that may lead to hospitalization or death [see Warnings and Precautions (5.1)]. Most patients who developed these infections were taking concomitant immunosuppressants such as methotrexate or corticosteroids.

Discontinue Adalimumab-aaty if a patient develops a serious infection or sepsis.

Reported infections include:

- Active tuberculosis (TB), including reactivation of latent TB. Patients with TB have frequently presented with disseminated or extrapulmonary disease. Test patients for latent TB before Adalimumab-aaty use and during therapy. Initiate treatment for latent TB prior to Adalimumab-aaty use.
- Invasive fungal infections, including histoplasmosis, coccidioidomycosis, candidiasis, aspergillosis, blastomycosis, and pneumocystosis. Patients with histoplasmosis or other invasive fungal infections may present with disseminated, rather than localized, disease. Antigen and antibody testing for histoplasmosis may be negative in some patients with active infection. Consider empiric anti-fungal therapy in patients at risk for invasive fungal infections who develop severe systemic illness.
- Bacterial, viral and other infections due to opportunistic pathogens, including Legionella and Listeria.

Carefully consider the risks and benefits of treatment with Adalimumab-aaty prior to initiating therapy in patients with chronic or recurrent infection.

Monitor patients closely for the development of signs and symptoms of infection during and after treatment with Adalimumab-aaty, including the possible development of TB in patients who tested negative for latent TB infection prior to initiating therapy [see Warnings and Precautions (5.1) and Adverse Reactions (6.1)].

MALIGNANCY

Lymphoma and other malignancies, some fatal, have been reported in children and adolescent patients treated with TNF blockers including adalimumab products [see Warnings and Precautions (5.2)]. Post-marketing cases of hepatosplenic T-cell lymphoma (HSTCL), a rare type of T-cell lymphoma, have been reported in patients treated with TNF blockers including adalimumab products. These cases have had a very aggressive disease course and have been fatal. The majority of reported TNF blocker cases have occurred in patients with Crohn's disease or ulcerative colitis and the majority were in adolescent and young adult males. Almost all these patients had received treatment with azathioprine or 6-mercaptopurine (6–MP) concomitantly with a TNF blocker at or prior to diagnosis. It is uncertain whether the occurrence of HSTCL is related to use of a TNF blocker or a TNF blocker in combination with these other immunosuppressants [see Warnings and Precautions (5.2)].

1 INDICATIONS AND USAGE

1.1 Rheumatoid Arthritis

Adalimumab-aaty is indicated for reducing signs and symptoms, inducing major clinical response, inhibiting the progression of structural damage, and improving physical function in adult patients with moderately to severely active rheumatoid arthritis. Adalimumab-aaty can be used alone or in combination with methotrexate or other non-biologic disease-modifying anti-rheumatic drugs (DMARDs).

1.2 Juvenile Idiopathic Arthritis

Adalimumab-aaty is indicated for reducing signs and symptoms of moderately to severely active polyarticular juvenile idiopathic arthritis in patients 2 years of age and older. Adalimumab-aaty can be used alone or in combination with methotrexate.

1.3 Psoriatic Arthritis

Adalimumab-aaty is indicated for reducing signs and symptoms, inhibiting the progression of structural damage, and improving physical function in adult patients with active psoriatic arthritis. Adalimumab-aaty can be used alone or in combination with non-biologic DMARDs.

1.4 Ankylosing Spondylitis

Adalimumab-aaty is indicated for reducing signs and symptoms in adult patients with active ankylosing spondylitis.

1.5 Crohn's Disease

Adalimumab-aaty is indicated for the treatment of moderately to severely active Crohn's disease in adults and pediatric patients 6 years of age and older.

1.6 Ulcerative Colitis

Adalimumab-aaty is indicated for the treatment of moderately to severely active ulcerative colitis in adult patients.

Limitations of Use

The effectiveness of adalimumab products has not been established in patients who have lost response to or were intolerant to TNF blockers [see Clinical Studies (14.7)].

1.7 Plaque Psoriasis

Adalimumab-aaty is indicated for the treatment of adult patients with moderate to severe chronic plaque psoriasis who are candidates for systemic therapy or phototherapy, and when other systemic therapies are medically less appropriate. Adalimumab-aaty should only be administered to patients who will be closely monitored and have regular follow-up visits with a physician [see Warnings and Precautions (5)].

1.8 Hidradenitis Suppurativa

Adalimumab-aaty is indicated for the treatment of moderate to severe hidradenitis suppurativa in patients 12 years of age and older.

1.9 Uveitis

Adalimumab-aaty is indicated for the treatment of non-infectious intermediate, posterior, and panuveitis in adults and pediatric patients 2 years of age and older.

2 DOSAGE AND ADMINISTRATION

2.1 Recommended Tuberculosis Evaluation

Prior to initiating Adalimumab-aaty and periodically during therapy, evaluate patients for active tuberculosis and test for latent infection [see Warnings and Precautions (5.1)].

2.2 Recommended Dosage in Rheumatoid Arthritis, Psoriatic Arthritis, and Ankylosing Spondylitis

The recommended subcutaneous dosage of Adalimumab-aaty for adult patients with rheumatoid arthritis (RA), psoriatic arthritis (PsA), or ankylosing spondylitis (AS) [see Indications and Usage (1.1, 1.3, 1.4)] is 40 mg administered every other week. Methotrexate (MTX), other non-biologic DMARDS, glucocorticoids, nonsteroidal anti-inflammatory drugs (NSAIDs), and/or analgesics may be continued during treatment with Adalimumab-aaty. In the treatment of RA, some patients not taking concomitant MTX may derive additional benefit from increasing the dosage of Adalimumab-aaty to 40 mg every week or 80 mg every other week.

2.3 Recommended Dosage in Juvenile Idiopathic Arthritis or Pediatric Patients with Uveitis

The recommended subcutaneous dosage of Adalimumab-aaty for pediatric patients 2 years of age and older with polyarticular juvenile idiopathic arthritis (JIA) or pediatric uveitis [see Indications and Usage (1.2, 1.9)], based on weight, is shown below. MTX, glucocorticoids, NSAIDs, and/or analgesics may be continued during treatment with Adalimumab-aaty.

Pediatric Weight (2 years of age and older) | Recommended Dosage
15 kg (33 lbs) to less than 30 kg (66 lbs) | 20 mg every other week
30 kg (66 lbs) and greater | 40 mg every other week

There is no dosage form for Adalimumab-aaty that allows weight-based dosing for pediatric patients below 15 kg.

Adalimumab products have not been studied in patients with polyarticular JIA or pediatric uveitis less than 2 years of age or in patients with a weight below 10 kg.

2.4 Recommended Dosage in Crohn's Disease

Subcutaneous Adult Dosage Regimen

The recommended subcutaneous dosage of Adalimumab-aaty for adult patients with moderately to severely active Crohn's disease (CD) is 160 mg initially on Day 1 (given in one day or split over two consecutive days), followed by 80 mg two weeks later (Day 15). Two weeks later (Day 29) begin a dosage of 40 mg every other week. Aminosalicylates and/or corticosteroids may be continued during treatment with Adalimumab-aaty. Azathioprine, 6-mercaptopurine (6-MP) [see Warnings and Precautions (5.2)] or MTX may be continued during treatment with Adalimumab-aaty if necessary.

Subcutaneous Pediatric Dosage Regimen

The recommended subcutaneous dosage of Adalimumab-aaty for pediatric patients 6 years of age and older with moderately to severely active Crohn's disease (CD), based on body weight, is shown below:

Pediatric Weight | Recommended Dosage
Pediatric Weight | Days 1 through 15 | Starting on Day 29
17 kg (37 lbs) to less than 40 kg (88 lbs) | Day 1: 80 mg Day 15: 40 mg | 20 mg every other week
40 kg (88 lbs) and greater | Day 1: 160 mg (single dose or split over two consecutive days) Day 15: 80 mg | 40 mg every other week

2.5 Recommended Dosage in Ulcerative Colitis

Subcutaneous Adult Dosage Regimen

The recommended subcutaneous dosage of Adalimumab-aaty for adult patients with moderately to severely active ulcerative colitis is 160 mg initially on Day 1 (given in one day or split over two consecutive days), followed by 80 mg two weeks later (Day 15). Two weeks later (Day 29) continue with a dosage of 40 mg every other week.

Discontinue Adalimumab-aaty in adult patients without evidence of clinical remission by eight weeks (Day 57) of therapy. Aminosalicylates and/or corticosteroids may be continued during treatment with Adalimumab-aaty. Azathioprine and 6-mercaptopurine (6-MP) [see Warnings and Precautions (5.2)] may be continued during treatment with Adalimumab-aaty if necessary.

2.6 Recommended Dosage in Plaque Psoriasis or Adults with Uveitis

The recommended subcutaneous dosage of Adalimumab-aaty for adult patients with plaque psoriasis (Ps) or uveitis (UV) [see Indications and Usage (1.7, 1.9)] is an initial dose of 80 mg, followed by 40 mg given every other week starting one week after the initial dose. The use of adalimumab products in moderate to severe chronic Ps beyond one year has not been evaluated in controlled clinical studies.

2.7 Recommended Dosage in Hidradenitis Suppurativa

Subcutaneous Adult Dosage Regimen

The recommended subcutaneous dosage of Adalimumab-aaty for adult patients with moderate to severe hidradenitis suppurativa (HS) is an initial dose of 160 mg (given in one day or split over two consecutive days), followed by 80 mg two weeks later (Day 15). Begin 40 mg weekly or 80 mg every other week dosing two weeks later (Day 29).

Subcutaneous Pediatric Dosage Regimen

The recommended subcutaneous dosage of Adalimumab-aaty for pediatric patients 12 years of age and older weighing at least 30 kg with moderate to severe hidradenitis suppurativa (HS), based on body weight, is shown below [see Use in Specific Populations (8.4) and Clinical Pharmacology (12.3)]:

Body Weight of Pediatric Patients (12 years of age and older) | Recommended Dosage
30 kg (66 lbs) to less than 60 kg (132 lbs) | Day 1: 80 mg Day 8 and subsequent doses: 40 mg every other week
60 kg (132 lbs) and greater | Day 1: 160 mg (given in one day or split over two consecutive days) Day 15: 80 mg Day 29 and subsequent doses: 40 mg every week or 80 mg every other week

2.8 General Considerations for Administration

Adalimumab-aaty is intended for use under the guidance and supervision of a physician. A patient may self-inject Adalimumab-aaty or a caregiver may inject Adalimumab-aaty using either the Adalimumab-aaty AI or Adalimumab-aaty prefilled syringe if a physician determines that it is appropriate, and with medical follow-up, as necessary, after proper training in subcutaneous injection technique.

Adalimumab-aaty can be taken out of the refrigerator for about 15 to 30 minutes before injecting to allow the liquid to come to room temperature. Do not remove the cap or cover while allowing it to reach room temperature. Do not shake. Carefully inspect the solution in the Adalimumab-aaty AI or Adalimumab-aaty prefilled syringe for particulate matter and discoloration prior to subcutaneous administration. If particulates and discolorations are noted, do not use the product. Adalimumab-aaty does not contain preservatives; therefore, discard unused portions of drug remaining from the syringe.

Instruct patients using the Adalimumab-aaty AI or Adalimumab-aaty prefilled syringe to inject the full amount in the syringe, according to the directions provided in the Instructions for Use [see Instructions for Use].

Injections should occur at separate sites in the thigh or abdomen. Rotate injection sites and do not give injections into areas where the skin is tender, bruised, red or hard.

If a dose is missed, administer the dose as soon as possible. Thereafter, resume dosing at the regular scheduled time.

3 DOSAGE FORMS AND STRENGTHS

Adalimumab-aaty is a clear to opalescent, and colorless to pale brown solution available as:

- Auto-injector (Adalimumab-aaty AI)
  Injection: 80 mg/0.8 mL in a single-dose auto-injector.
  Injection: 40 mg/0.4 mL in a single-dose auto-injector.
- Prefilled Syringe with Safety Guard
  Injection: 80 mg/0.8 mL in a single-dose prefilled syringe with safety guard.
  Injection: 40 mg/0.4 mL in a single-dose prefilled syringe with safety guard.
- Prefilled Syringe
  Injection: 80 mg/0.8 mL in a single-dose prefilled syringe.
  Injection: 40 mg/0.4 mL in a single-dose prefilled syringe.
  Injection: 20 mg/0.2 mL in a single-dose prefilled syringe.

4 CONTRAINDICATIONS

None.

5 WARNINGS AND PRECAUTIONS

5.1 Serious Infections

Patients treated with adalimumab products, including Adalimumab-aaty, are at increased risk for developing serious infections involving various organ systems and sites that may lead to hospitalization or death. Opportunistic infections due to bacterial, mycobacterial, invasive fungal, viral, parasitic, or other opportunistic pathogens including aspergillosis, blastomycosis, candidiasis, coccidioidomycosis, histoplasmosis, legionellosis, listeriosis, pneumocystosis and tuberculosis have been reported with TNF blockers. Patients have frequently presented with disseminated rather than localized disease.

The concomitant use of a TNF blocker and abatacept or anakinra was associated with a higher risk of serious infections in patients with rheumatoid arthritis (RA); therefore, the concomitant use of Adalimumab-aaty and these biologic products is not recommended in the treatment of patients with RA [see Warnings and Precautions (5.7, 5.11) and Drug Interactions (7.2)].

Treatment with Adalimumab-aaty should not be initiated in patients with an active infection, including localized infections. Patients 65 years of age and older, patients with co-morbid conditions and/or patients taking concomitant immunosuppressants (such as corticosteroids or methotrexate), may be at greater risk of infection. Consider the risks and benefits of treatment prior to initiating therapy in patients:

- with chronic or recurrent infection;
- who have been exposed to tuberculosis;
- with a history of an opportunistic infection;
- who have resided or traveled in areas of endemic tuberculosis or endemic mycoses, such as histoplasmosis, coccidioidomycosis, or blastomycosis; or
- with underlying conditions that may predispose them to infection.

Tuberculosis

Cases of reactivation of tuberculosis and new onset tuberculosis infections have been reported in patients receiving adalimumab products, including patients who have previously received treatment for latent or active tuberculosis. Reports included cases of pulmonary and extrapulmonary (i.e., disseminated) tuberculosis. Evaluate patients for tuberculosis risk factors and test for latent infection prior to initiating Adalimumab-aaty and periodically during therapy.

Treatment of latent tuberculosis infection prior to therapy with TNF blocking agents has been shown to reduce the risk of tuberculosis reactivation during therapy. Prior to initiating Adalimumab-aaty, assess if treatment for latent tuberculosis is needed; and consider an induration of ≥ 5 mm a positive tuberculin skin test result, even for patients previously vaccinated with Bacille Calmette-Guerin (BCG).

Consider anti-tuberculosis therapy prior to initiation of Adalimumab-aaty in patients with a past history of latent or active tuberculosis in whom an adequate course of treatment cannot be confirmed, and for patients with a negative test for latent tuberculosis but having risk factors for tuberculosis infection. Despite prophylactic treatment for tuberculosis, cases of reactivated tuberculosis have occurred in patients treated with adalimumab products. Consultation with a physician with expertise in the treatment of tuberculosis is recommended to aid in the decision whether initiating anti-tuberculosis therapy is appropriate for an individual patient.

Strongly consider tuberculosis in the differential diagnosis in patients who develop a new infection during Adalimumab-aaty treatment, especially in patients who have previously or recently traveled to countries with a high prevalence of tuberculosis, or who have had close contact with a person with active tuberculosis.

Monitoring

Closely monitor patients for the development of signs and symptoms of infection during and after treatment with Adalimumab-aaty, including the development of tuberculosis in patients who tested negative for latent tuberculosis infection prior to initiating therapy. Tests for latent tuberculosis infection may also be falsely negative while on therapy with Adalimumab-aaty.

Discontinue Adalimumab-aaty if a patient develops a serious infection or sepsis. For a patient who develops a new infection during treatment with Adalimumab-aaty, closely monitor them, perform a prompt and complete diagnostic workup appropriate for an immunocompromised patient, and initiate appropriate antimicrobial therapy.

Invasive Fungal Infections

If patients develop a serious systemic illness and they reside or travel in regions where mycoses are endemic, consider invasive fungal infection in the differential diagnosis. Antigen and antibody testing for histoplasmosis may be negative in some patients with active infection. Consider appropriate empiric antifungal therapy, taking into account both the risk for severe fungal infection and the risks of antifungal therapy, while a diagnostic workup is being performed. To aid in the management of such patients, consider consultation with a physician with expertise in the diagnosis and treatment of invasive fungal infections.

5.2 Malignancies

Consider the risks and benefits of TNF-blocker treatment including Adalimumab-aaty prior to initiating therapy in patients with a known malignancy other than a successfully treated non-melanoma skin cancer (NMSC) or when considering continuing a TNF blocker in patients who develop a malignancy.

Malignancies in Adults

In the controlled portions of clinical trials of some TNF-blockers, including adalimumab products, more cases of malignancies have been observed among TNF-blocker-treated adult subjects compared to control-treated adult subjects. During the controlled portions of 39 global adalimumab clinical trials in adult patients with rheumatoid arthritis (RA), psoriatic arthritis (PsA), ankylosing spondylitis (AS), Crohn's disease (CD), ulcerative colitis (UC), plaque psoriasis (Ps), hidradenitis suppurativa (HS) and uveitis (UV), malignancies, other than non-melanoma (basal cell and squamous cell) skin cancer, were observed at a rate (95% confidence interval) of 0.7 (0.48, 1.03) per 100 patient-years among 7973 adalimumab-treated subjects versus a rate of 0.7 (0.41, 1.17) per 100 patient-years among 4848 control-treated subjects (median duration of treatment of 4 months for adalimumab-treated subjects and 4 months for control-treated subjects). In 52 global controlled and uncontrolled clinical trials of adalimumab in adult patients with RA, PsA, AS, CD, UC, Ps, HS and UV, the most frequently observed malignancies, other than lymphoma and NMSC, were breast, colon, prostate, lung, and melanoma. The malignancies in adalimumab-treated subjects in the controlled and uncontrolled portions of the studies were similar in type and number to what would be expected in the general U.S. population according to the SEER database (adjusted for age, gender, and race).^1

In controlled trials of other TNF blockers in adult patients at higher risk for malignancies (i.e., subjects with COPD with a significant smoking history and cyclophosphamide-treated patients with Wegener's granulomatosis), a greater portion of malignancies occurred in the TNF blocker group compared to the control group.

Non-Melanoma Skin Cancer

During the controlled portions of 39 global adalimumab clinical trials in adult patients with RA, PsA, AS, CD, UC, Ps, HS and UV, the rate (95% confidence interval) of NMSC was 0.8 (0.52, 1.09) per 100 patient-years among adalimumab-treated subjects and 0.2 (0.10, 0.59) per 100 patient-years among control-treated subjects. Examine all patients, and in particular patients with a medical history of prior prolonged immunosuppressant therapy or psoriasis patients with a history of PUVA treatment for the presence of NMSC prior to and during treatment with Adalimumab-aaty.

Lymphoma and Leukemia

In the controlled portions of clinical trials of all the TNF-blockers in adults, more cases of lymphoma have been observed among TNF-blocker-treated subjects compared to control-treated subjects. In the controlled portions of 39 global adalimumab clinical trials in adult patients with RA, PsA, AS, CD, UC, Ps, HS and UV, 2 lymphomas occurred among 7973 adalimumab-treated subjects versus 1 among 4848 control-treated subjects. In 52 global controlled and uncontrolled clinical trials of adalimumab in adult patients with RA, PsA, AS, CD, UC, Ps, HS and UV with a median duration of approximately 0.7 years, including 24,605 subjects and over 40,215 patient-years of adalimumab, the observed rate of lymphomas was approximately 0.11 per 100 patient-years. This is approximately 3-fold higher than expected in the general U.S. population according to the SEER database (adjusted for age, gender, and race).^1 Rates of lymphoma in clinical trials of adalimumab cannot be compared to rates of lymphoma in clinical trials of other TNF blockers and may not predict the rates observed in a broader patient population. Patients with RA and other chronic inflammatory diseases, particularly those with highly active disease and/or chronic exposure to immunosuppressant therapies, may be at a higher risk (up to several fold) than the general population for the development of lymphoma, even in the absence of TNF blockers. Post-marketing cases of acute and chronic leukemia have been reported in association with TNF-blocker use in RA and other indications. Even in the absence of TNF-blocker therapy, patients with RA may be at a higher risk (approximately 2-fold) than the general population for the development of leukemia.

Malignancies in Pediatric Patients and Young Adults

Malignancies, some fatal, have been reported among children, adolescents, and young adults who received treatment with TNF-blockers (initiation of therapy ≤ 18 years of age), of which Adalimumab-aaty is a member. Approximately half the cases were lymphomas, including Hodgkin's and non-Hodgkin's lymphoma. The other cases represented a variety of different malignancies and included rare malignancies usually associated with immunosuppression and malignancies that are not usually observed in children and adolescents. The malignancies occurred after a median of 30 months of therapy (range 1 to 84 months). Most of the patients were receiving concomitant immunosuppressants. These cases were reported post-marketing and are derived from a variety of sources including registries and spontaneous postmarketing reports.

Postmarketing cases of hepatosplenic T-cell lymphoma (HSTCL), a rare type of T-cell lymphoma, have been reported in patients treated with TNF blockers including adalimumab products. These cases have had a very aggressive disease course and have been fatal. The majority of reported TNF blocker cases have occurred in patients with Crohn's disease or ulcerative colitis and the majority were in adolescent and young adult males. Almost all of these patients had received treatment with the immunosuppressants azathioprine or 6-mercaptopurine (6–MP) concomitantly with a TNF blocker at or prior to diagnosis. It is uncertain whether the occurrence of HSTCL is related to use of a TNF blocker or a TNF blocker in combination with these other immunosuppressants. The potential risk with the combination of azathioprine or 6-mercaptopurine and Adalimumab-aaty should be carefully considered.

5.3 Hypersensitivity Reactions

Anaphylaxis and angioneurotic edema have been reported following administration of adalimumab products. If an anaphylactic or other serious allergic reaction occurs, immediately discontinue administration of Adalimumab-aaty and institute appropriate therapy. In clinical trials of adalimumab, hypersensitivity reactions (e.g., rash, anaphylactoid reaction, fixed drug reaction, non-specified drug reaction, urticaria) have been observed.

5.4 Hepatitis B Virus Reactivation

Use of TNF blockers, including Adalimumab-aaty, may increase the risk of reactivation of hepatitis B virus (HBV) in patients who are chronic carriers of this virus. In some instances, HBV reactivation occurring in conjunction with TNF blocker therapy has been fatal. The majority of these reports have occurred in patients concomitantly receiving other medications that suppress the immune system, which may also contribute to HBV reactivation. Evaluate patients at risk for HBV infection for prior evidence of HBV infection before initiating TNF blocker therapy. Exercise caution in prescribing TNF blockers for patients identified as carriers of HBV. Adequate data are not available on the safety or efficacy of treating patients who are carriers of HBV with anti-viral therapy in conjunction with TNF blocker therapy to prevent HBV reactivation. For patients who are carriers of HBV and require treatment with TNF blockers, closely monitor such patients for clinical and laboratory signs of active HBV infection throughout therapy and for several months following termination of therapy. In patients who develop HBV reactivation, stop Adalimumab-aaty and initiate effective anti-viral therapy with appropriate supportive treatment. The safety of resuming TNF blocker therapy after HBV reactivation is controlled is not known. Therefore, exercise caution when considering resumption of Adalimumab-aaty therapy in this situation and monitor patients closely.

5.5 Neurologic Reactions

Use of TNF blocking agents, including adalimumab products, has been associated with rare cases of new onset or exacerbation of clinical symptoms and/or radiographic evidence of central nervous system demyelinating disease, including multiple sclerosis (MS) and optic neuritis, and peripheral demyelinating disease, including Guillain-Barré syndrome. Exercise caution in considering the use of Adalimumab-aaty in patients with preexisting or recent-onset central or peripheral nervous system demyelinating disorders; discontinuation of Adalimumab-aaty should be considered if any of these disorders develop. There is a known association between intermediate uveitis and central demyelinating disorders.

5.6 Hematological Reactions

Rare reports of pancytopenia including aplastic anemia have been reported with TNF blocking agents. Adverse reactions of the hematologic system, including medically significant cytopenia (e.g., thrombocytopenia, leukopenia) have been infrequently reported with adalimumab products. The causal relationship of these reports to adalimumab products remains unclear. Advise all patients to seek immediate medical attention if they develop signs and symptoms suggestive of blood dyscrasias or infection (e.g., persistent fever, bruising, bleeding, pallor) while on Adalimumab-aaty. Consider discontinuation of Adalimumab-aaty therapy in patients with confirmed significant hematologic abnormalities.

5.7 Increased Risk of Infection when Used with Anakinra

Concurrent use of anakinra (an interleukin-1 antagonist) and another TNF-blocker, was associated with a greater proportion of serious infections and neutropenia and no added benefit compared with the TNF-blocker alone in patients with RA. Therefore, the combination of Adalimumab-aaty and anakinra is not recommended [see Drug Interactions (7.2)].

5.8 Heart Failure

Cases of worsening congestive heart failure (CHF) and new onset CHF have been reported with TNF blockers. Cases of worsening CHF have also been observed with adalimumab products. Adalimumab products have not been formally studied in patients with CHF; however, in clinical trials of another TNF blocker, a higher rate of serious CHF-related adverse reactions was observed. Exercise caution when using Adalimumab-aaty in patients who have heart failure and monitor them carefully.

5.9 Autoimmunity

Treatment with adalimumab products may result in the formation of autoantibodies and, rarely, in the development of a lupus-like syndrome or autoimmune hepatitis [see Adverse Reactions (6.1, 6.3)]. If a patient develops symptoms and findings suggestive of a lupus-like syndrome or autoimmune hepatitis following treatment with Adalimumab-aaty, discontinue treatment and evaluate the patient.

5.10 Immunizations

In a placebo-controlled clinical trial of patients with RA, no difference was detected in anti-pneumococcal antibody response between adalimumab and placebo treatment groups when the pneumococcal polysaccharide vaccine and influenza vaccine were administered concurrently with adalimumab. Similar proportions of subjects developed protective levels of anti-influenza antibodies between adalimumab and placebo treatment groups; however, titers in aggregate to influenza antigens were moderately lower in patients receiving adalimumab. The clinical significance of this is unknown. Patients on Adalimumab-aaty may receive concurrent vaccinations, except for live vaccines. No data are available on the secondary transmission of infection by live vaccines in patients receiving adalimumab products.

It is recommended that pediatric patients, if possible, be brought up to date with all immunizations in agreement with current immunization guidelines prior to initiating Adalimumab-aaty therapy. Patients on Adalimumab-aaty may receive concurrent vaccinations, except for live vaccines.

The safety of administering live or live-attenuated vaccines in infants exposed to adalimumab products in utero is unknown. Risks and benefits should be considered prior to vaccinating (live or live-attenuated) exposed infants [see Use in Specific Populations (8.1, 8.4)].

5.11 Increased Risk of Infection When Used with Abatacept

In controlled trials, the concurrent administration of TNF-blockers and abatacept was associated with a greater proportion of serious infections than the use of a TNF-blocker alone; the combination therapy, compared to the use of a TNF-blocker alone, has not demonstrated improved clinical benefit in the treatment of RA. Therefore, the combination of abatacept with TNF-blockers including Adalimumab-aaty is not recommended [see Drug Interactions (7.2)].

6 ADVERSE REACTIONS

The following clinically significant adverse reactions are described elsewhere in the labeling:

- Serious Infections [see Warnings and Precautions (5.1)]
- Malignancies [see Warnings and Precautions (5.2)]
- Hypersensitivity Reactions [see Warnings and Precautions (5.3)]
- Hepatitis B Virus Reactivation [see Warnings and Precautions (5.4)]
- Neurologic Reactions [see Warnings and Precautions (5.5)]
- Hematological Reactions [see Warnings and Precautions (5.6)]
- Heart Failure [see Warnings and Precautions (5.8)]
- Autoimmunity [see Warnings and Precautions (5.9)]

6.1 Clinical Trials Experience

Because clinical trials are conducted under widely varying conditions, adverse reaction rates observed in the clinical trials of a drug cannot be directly compared to rates in the clinical trials of another drug and may not reflect the rates observed in practice.

The most common adverse reaction with adalimumab was injection site reactions. In placebo-controlled trials, 20% of subjects treated with adalimumab developed injection site reactions (erythema and/or itching, hemorrhage, pain or swelling), compared to 14% of subjects receiving placebo. Most injection site reactions were described as mild and generally did not necessitate drug discontinuation.

The proportion of subjects who discontinued treatment due to adverse reactions during the double-blind, placebo-controlled portion of studies in subjects with RA (i.e., Studies RA-I, RA-II, RA-III and RA-IV) was 7% for subjects taking adalimumab and 4% for placebo-treated subjects. The most common adverse reactions leading to discontinuation of adalimumab in these RA studies were clinical flare reaction (0.7%), rash (0.3%) and pneumonia (0.3%).

Infections

In the controlled portions of the 39 global adalimumab clinical trials in adult subjects with RA, PsA, AS, CD, UC, Ps, HS and UV, the rate of serious infections was 4.3 per 100 patient-years in 7973 adalimumab-treated subjects versus a rate of 2.9 per 100 patient-years in 4848 control-treated subjects. Serious infections observed included pneumonia, septic arthritis, prosthetic and post-surgical infections, erysipelas, cellulitis, diverticulitis, and pyelonephritis [see Warnings and Precautions (5.1)].

Tuberculosis and Opportunistic Infections

In 52 global controlled and uncontrolled clinical trials in RA, PsA, AS, CD, UC, Ps, HS and UV that included 24,605 adalimumab-treated subjects, the rate of reported active tuberculosis was 0.20 per 100 patient-years and the rate of positive PPD conversion was 0.09 per 100 patient-years. In a subgroup of 10,113 U.S. and Canadian adalimumab-treated subjects, the rate of reported active TB was 0.05 per 100 patient-years and the rate of positive PPD conversion was 0.07 per 100 patient-years. These trials included reports of miliary, lymphatic, peritoneal, and pulmonary TB. Most of the TB cases occurred within the first eight months after initiation of therapy and may reflect recrudescence of latent disease. In these global clinical trials, cases of serious opportunistic infections have been reported at an overall rate of 0.05 per 100 patient-years. Some cases of serious opportunistic infections and TB have been fatal [see Warnings and Precautions (5.1)].

Autoantibodies

In the rheumatoid arthritis-controlled trials, 12% of subjects treated with adalimumab and 7% of placebo-treated subjects that had negative baseline ANA titers developed positive titers at week 24. Two subjects out of 3046 treated with adalimumab developed clinical signs suggestive of new-onset lupus-like syndrome. The subjects improved following discontinuation of therapy. No subjects developed lupus nephritis or central nervous system symptoms. The impact of long-term treatment with adalimumab products on the development of autoimmune diseases is unknown.

Liver Enzyme Elevations

There have been reports of severe hepatic reactions including acute liver failure in subjects receiving TNF-blockers. In controlled Phase 3 trials of adalimumab (40 mg SC every other week) in subjects with RA, PsA, and AS with control period duration ranging from 4 to 104 weeks, ALT elevations ≥ 3 × ULN occurred in 3.5% of adalimumab-treated subjects and 1.5% of control-treated subjects. Since many of these subjects in these trials were also taking medications that cause liver enzyme elevations (e.g., NSAIDS, MTX), the relationship between adalimumab and the liver enzyme elevations is not clear. In a controlled Phase 3 trial of adalimumab in subjects with polyarticular JIA who were 4 to 17 years, ALT elevations ≥ 3 × ULN occurred in 4.4% of adalimumab-treated subjects and 1.5% of control-treated subjects (ALT more common than AST); liver enzyme test elevations were more frequent among those treated with the combination of adalimumab and MTX than those treated with adalimumab alone. In general, these elevations did not lead to discontinuation of adalimumab treatment. No ALT elevations ≥ 3 × ULN occurred in the open-label study of adalimumab in subjects with polyarticular JIA who were 2 to < 4 years.

In controlled Phase 3 trials of adalimumab (initial doses of 160 mg and 80 mg, or 80 mg and 40 mg on Days 1 and 15, respectively, followed by 40 mg every other week) in adult subjects with Crohn's disease with a control period duration ranging from 4 to 52 weeks, ALT elevations ≥ 3 × ULN occurred in 0.9% of adalimumab-treated subjects and 0.9% of control-treated subjects. In the Phase 3 trial of adalimumab in pediatric subjects with Crohn's disease which evaluated efficacy and safety of two body weight based maintenance dose regimens following body weight based induction therapy up to 52 weeks of treatment, ALT elevations ≥ 3 × ULN occurred in 2.6% (5/192) of subjects, of whom 4 were receiving concomitant immunosuppressants at baseline; none of these subjects discontinued due to abnormalities in ALT tests. In controlled Phase 3 trials of adalimumab (initial doses of 160 mg and 80 mg on Days 1 and 15 respectively, followed by 40 mg every other week) in adult subjects with UC with control period duration ranging from 1 to 52 weeks, ALT elevations ≥ 3 × ULN occurred in 1.5% of adalimumab-treated subjects and 1.0% of control-treated subjects. In controlled Phase 3 trials of adalimumab (initial dose of 80 mg then 40 mg every other week) in subjects with Ps with control period duration ranging from 12 to 24 weeks, ALT elevations ≥ 3 × ULN occurred in 1.8% of adalimumab-treated subjects and 1.8% of control-treated subjects. In controlled trials of adalimumab (initial doses of 160 mg at Week 0 and 80 mg at Week 2, followed by 40 mg every week starting at Week 4), in subjects with HS with a control period duration ranging from 12 to 16 weeks, ALT elevations ≥ 3 × ULN occurred in 0.3% of adalimumab-treated subjects and 0.6% of control-treated subjects. In controlled trials of adalimumab (initial doses of 80 mg at Week 0 followed by 40 mg every other week starting at Week 1) in adult subjects with uveitis with an exposure of 165.4 PYs and 119.8 PYs in adalimumab-treated and control-treated subjects, respectively, ALT elevations ≥ 3 x ULN occurred in 2.4% of adalimumab-treated subjects and 2.4% of control-treated subjects.

Other Adverse Reactions

Rheumatoid Arthritis Clinical Studies

The data described below reflect exposure to adalimumab in 2468 subjects, including 2073 exposed for 6 months, 1497 exposed for greater than one year and 1380 in adequate and well-controlled studies (Studies RA-I, RA-II, RA-III, and RA-IV). Adalimumab was studied primarily in placebo-controlled trials and in long-term follow up studies for up to 36 months duration. The population had a mean age of 54 years, 77% were female, 91% were Caucasian and had moderately to severely active rheumatoid arthritis. Most subjects received 40 mg adalimumab every other week [see Clinical Studies (14.1)].

Table 1 summarizes reactions reported at a rate of at least 5% in subjects treated with adalimumab 40 mg every other week compared to placebo and with an incidence higher than placebo. In Study RA-III, the types and frequencies of adverse reactions in the second year open-label extension were similar to those observed in the one-year double-blind portion.

Table 1. Adverse Reactions Reported by ≥ 5% of Subjects with Adalimumab During Placebo-Controlled Period of Pooled RA Studies (Studies RA-I, RA-II, RA-III, and RA-IV)
 | Adalimumab 40 mg subcutaneous Every Other Week | Placebo
 | (N=705) | (N=690)
Adverse Reaction (Preferred Term)
Respiratory
Upper respiratory infection | 17% | 13%
Sinusitis | 11% | 9%
Flu syndrome | 7% | 6%
Gastrointestinal
Nausea | 9% | 8%
Abdominal pain | 7% | 4%
Laboratory Tests*
Laboratory test abnormal | 8% | 7%
Hypercholesterolemia | 6% | 4%
Hyperlipidemia | 7% | 5%
Hematuria | 5% | 4%
Alkaline phosphatase increased | 5% | 3%
Other
Headache | 12% | 8%
Rash | 12% | 6%
Accidental injury | 10% | 8%
Injection site reaction ** | 8% | 1%
Back pain | 6% | 4%
Urinary tract infection | 8% | 5%
Hypertension | 5% | 3%
* Laboratory test abnormalities were reported as adverse reactions in European trials
** Does not include injection site erythema, itching, hemorrhage, pain or swelling

Less Common Adverse Reactions in Rheumatoid Arthritis Clinical Studies

Other infrequent serious adverse reactions that do not appear in the Warnings and Precautions or Adverse Reaction sections that occurred at an incidence of less than 5% in adalimumab-treated subjects in RA studies (RA-I, RA-II, RA-III, and RA-IV) were:

Body As A Whole: Pain in extremity, pelvic pain, surgery, thorax pain

Cardiovascular System: Arrhythmia, atrial fibrillation, chest pain, coronary artery disorder, heart arrest, hypertensive encephalopathy, myocardial infarct, palpitation, pericardial effusion, pericarditis, syncope, tachycardia

Digestive System: Cholecystitis, cholelithiasis, esophagitis, gastroenteritis, gastrointestinal hemorrhage, hepatic necrosis, vomiting

Endocrine System: Parathyroid disorder

Hemic And Lymphatic System: Agranulocytosis, polycythemia

Metabolic And Nutritional Disorders: Dehydration, healing abnormal, ketosis, paraproteinemia, peripheral edema

Musculo-Skeletal System: Arthritis, bone disorder, bone fracture (not spontaneous), bone necrosis, joint disorder, muscle cramps, myasthenia, pyogenic arthritis, synovitis, tendon disorder

Neoplasia: Adenoma

Nervous System: Confusion, paresthesia, subdural hematoma, tremor

Respiratory System: Asthma, bronchospasm, dyspnea, lung function decreased, pleural effusion

Special Senses: Cataract

Thrombosis: Thrombosis leg

Urogenital System: Cystitis, kidney calculus, menstrual disorder

Juvenile Idiopathic Arthritis Clinical Studies

In general, the adverse reactions in the adalimumab-treated subjects in the polyarticular juvenile idiopathic arthritis (JIA) trials (Studies JIA-I and JIA-II) [see Clinical Studies (14.2)] were similar in frequency and type to those seen in adult subjects [see Warnings and Precautions (5), Adverse Reactions (6)]. Important findings and differences from adults are discussed in the following paragraphs.

In Study JIA-I, adalimumab was studied in 171 subjects who were 4 to 17 years of age, with polyarticular JIA. Severe adverse reactions reported in the study included neutropenia, streptococcal pharyngitis, increased aminotransferases, herpes zoster, myositis, metrorrhagia, and appendicitis. Serious infections were observed in 4% of subjects within approximately 2 years of initiation of treatment with adalimumab and included cases of herpes simplex, pneumonia, urinary tract infection, pharyngitis, and herpes zoster.

In Study JIA-I, 45% of subjects experienced an infection while receiving adalimumab with or without concomitant MTX in the first 16 weeks of treatment. The types of infections reported in adalimumab-treated subjects were generally similar to those commonly seen in polyarticular JIA subjects who are not treated with TNF blockers. Upon initiation of treatment, the most common adverse reactions occurring in this population treated with adalimumab were injection site pain and injection site reaction (19% and 16%, respectively). A less commonly reported adverse event in subjects receiving adalimumab was granuloma annulare which did not lead to discontinuation of adalimumab treatment.

In the first 48 weeks of treatment in Study JIA-I, non-serious hypersensitivity reactions were seen in approximately 6% of subjects and included primarily localized allergic hypersensitivity reactions and allergic rash.

In Study JIA-I, 10% of subjects treated with adalimumab who had negative baseline anti-dsDNA antibodies developed positive titers after 48 weeks of treatment. No subject developed clinical signs of autoimmunity during the clinical trial.

Approximately 15% of subjects treated with adalimumab developed mild-to-moderate elevations of creatine phosphokinase (CPK) in Study JIA-I. Elevations exceeding 5 times the upper limit of normal were observed in several subjects. CPK concentrations decreased or returned to normal in all subjects. Most subjects were able to continue adalimumab without interruption.

In Study JIA-II, adalimumab was studied in 32 subjects who were 2 to < 4 years of age or 4 years of age and older weighing < 15 kg with polyarticular JIA. The safety profile for this population was similar to the safety profile seen in subjects 4 to 17 years of age with polyarticular JIA.

In Study JIA-II, 78% of subjects experienced an infection while receiving adalimumab. These included nasopharyngitis, bronchitis, upper respiratory tract infection, otitis media, and were mostly mild to moderate in severity. Serious infections were observed in 9% of subjects receiving adalimumab in the study and included dental caries, rotavirus gastroenteritis, and varicella.

In Study JIA-II, non-serious allergic reactions were observed in 6% of subjects and included intermittent urticaria and rash, which were all mild in severity.

Psoriatic Arthritis and Ankylosing Spondylitis Clinical Studies

Adalimumab has been studied in 395 subjects with psoriatic arthritis (PsA) in two placebo-controlled trials and in an open label study and in 393 subjects with ankylosing spondylitis (AS) in two placebo-controlled studies [see Clinical Studies (14.3, 14.4)]. The safety profile for subjects with PsA and AS treated with adalimumab 40 mg every other week was similar to the safety profile seen in subjects with RA, adalimumab Studies RA-I through IV.

Crohn's Disease Clinical Studies

Adults: The safety profile of adalimumab in 1478 adult subjects with Crohn's disease from four placebo-controlled and two open-label extension studies [see Clinical Studies (14.5)] was similar to the safety profile seen in subjects with RA.

Pediatric Patients 6 Years to 17 Years: The safety profile of adalimumab in 192 pediatric subjects from one double-blind study (Study PCD-I) and one open-label extension study [see Clinical Studies (14.6)] was similar to the safety profile seen in adult subjects with Crohn's disease.

During the 4-week open label induction phase of Study PCD-I, the most common adverse reactions occurring in the pediatric population treated with adalimumab were injection site pain and injection site reaction (6% and 5%, respectively).

A total of 67% of children experienced an infection while receiving adalimumab in Study PCD-I. These included upper respiratory tract infection and nasopharyngitis.

A total of 5% of children experienced a serious infection while receiving adalimumab in Study PCD-I. These included viral infection, device related sepsis (catheter), gastroenteritis, H1N1 influenza, and disseminated histoplasmosis.

In Study PCD-I, allergic reactions were observed in 5% of children which were all non-serious and were primarily localized reactions.

Ulcerative Colitis Clinical Studies

Adults: The safety profile of adalimumab in 1010 adult subjects with ulcerative colitis (UC) from two placebo-controlled studies and one open-label extension study [see Clinical Studies (14.7)] was similar to the safety profile seen in subjects with RA.

Plaque Psoriasis Clinical Studies

Adalimumab has been studied in 1696 subjects with plaque psoriasis (Ps) in placebo-controlled and open-label extension studies [see Clinical Studies (14.8)]. The safety profile for subjects with Ps treated with adalimumab was similar to the safety profile seen in subjects with RA with the following exceptions. In the placebo-controlled portions of the clinical trials in Ps subjects, adalimumab-treated subjects had a higher incidence of arthralgia when compared to controls (3% vs. 1%).

Hidradenitis Suppurativa Clinical Studies

Adalimumab has been studied in 727 subjects with hidradenitis suppurativa (HS) in three placebo-controlled studies and one open-label extension study [see Clinical Studies (14.9)]. The safety profile for subjects with HS treated with adalimumab weekly was consistent with the known safety profile of adalimumab.

Flare of HS, defined as ≥ 25% increase from baseline in abscesses and inflammatory nodule counts and with a minimum of 2 additional lesions, was documented in 22 (22%) of the 100 subjects who were withdrawn from adalimumab treatment following the primary efficacy timepoint in two studies.

Uveitis Clinical Studies

Adalimumab has been studied in 464 adult subjects with uveitis (UV) in placebo-controlled and open-label extension studies and in 90 pediatric subjects with uveitis (Study PUV-I) [see Clinical Studies (14.10, 14.11)]. The safety profile for subjects with UV treated with adalimumab was similar to the safety profile seen in subjects with RA.

6.2 Immunogenicity

The observed incidence of anti-drug antibodies is highly dependent on the sensitivity and specificity of the assay. Differences in assay methods preclude meaningful comparisons of the incidence of anti-drug antibodies in the studies described below with the incidence of anti-drug antibodies in other studies, including those of adalimumab or of other adalimumab products.

There are two assays that have been used to measure anti-adalimumab antibodies. With the ELISA, antibodies to adalimumab could be detected only when serum adalimumab concentrations were < 2 mcg/mL. The ECL assay can detect anti-adalimumab antibody titers independent of adalimumab concentrations in the serum samples. The incidence of anti-adalimumab antibody (AAA) development in patients treated with adalimumab are presented in Table 2.

Table 2: Anti-Adalimumab Antibody Development Determined by ELISA and ECL Assay in Patients Treated with Adalimumab
Indications |  | Study Duration | Anti-Adalimumab Antibody Incidence by ELISA (n/N) |  | Anti-Adalimumab Antibody Incidence by ECL Assay (n/N)
 |  |  | In all patients who received adalimumab | In patients with serum adalimumab concentrations < 2 mcg/mL
Rheumatoid Arthritisa |  | 6 to 12 months | 5% (58/1062) | NR | NA
Juvenile Idiopathic Arthritis (JIA) | 4 to 17 years of ageb | 48 weeks | 16% (27/171) | NR | NA
 | 2 to 4 years of age or ≥ 4 years of age and weighing < 15 kg | 24 weeks | 7% (1/15)c | NR | NA
Psoriatic Arthritisd |  | 48 weekse | 13% (24/178) | NR | NA
Ankylosing Spondylitis |  | 24 weeks | 9% (16/185) | NR | NA
Adult Crohn’s Disease |  | 56 weeks | 3% (7/269) | 8% (7/86) | NA
Pediatric Crohn’s Disease |  | 52 weeks | 3% (6/182) | 10% (6/58) | NA
Adult Ulcerative Colitis |  | 52 weeks | 5% (19/360) | 21% (19/92) | NA
Plaque Psoriasisf |  | Up to 52 weeksg | 8% (77/920) | 21% (77/372) | NA
Hidradenitis Suppurativa |  | 36 weeks | 7% (30/461) | 28% (58/207)h | 61% (272/445)i
Non-infectious Uveitis |  | 52 weeks | 5% (12/249) | 21% (12/57) | 40% (99/249)j
n: number of patients with anti-adalimumab antibody; NR: not reported; NA: Not applicable (not performed)
a In patients receiving concomitant methotrexate (MTX), the incidence of anti-adalimumab antibody was 1% compared to 12% with adalimumab monotherapy
b In patients receiving concomitant MTX, the incidence of anti-adalimumab antibody was 6% compared to 26% with adalimumab monotherapy
c This patient received concomitant MTX
d In patients receiving concomitant MTX, the incidence of antibody development was 7% compared to 1% in RA
e Subjects enrolled after completing 2 previous studies of 24 weeks or 12 weeks of treatments.
f In plaque psoriasis patients who were on adalimumab monotherapy and subsequently withdrawn from the treatment, the rate of antibodies to adalimumab after retreatment was similar to the rate observed prior to withdrawal
g One 12-week Phase 2 study and one 52-week Phase 3 study
h Among subjects in the 2 Phase 3 studies who stopped adalimumab treatment for up to 24 weeks and in whom adalimumab serum levels subsequently declined to <2 mcg/mL (approximately 22% of total subjects studied)
i No apparent association between antibody development and safety was observed
j No correlation of antibody development to safety or efficacy outcomes was observed

Rheumatoid Arthritis and Psoriatic Arthritis: Subjects in Studies RA-I, RA-II, and RA-III were tested at multiple time points for antibodies to adalimumab using the ELISA during the 6- to 12-month period. No apparent correlation of antibody development to adverse reactions was observed. With monotherapy, subjects receiving every other week dosing may develop antibodies more frequently than those receiving weekly dosing. In subjects receiving the recommended dosage of 40 mg every other week as monotherapy, the ACR 20 response was lower among antibody-positive subjects than among antibody-negative subjects. The long-term immunogenicity of adalimumab products is unknown.

6.3 Postmarketing Experience

The following adverse reactions have been identified during post-approval use of adalimumab products. Because these reactions are reported voluntarily from a population of uncertain size, it is not always possible to reliably estimate their frequency or establish a causal relationship to adalimumab products exposure.

Gastrointestinal disorders: Diverticulitis, large bowel perforations including perforations associated with diverticulitis and appendiceal perforations associated with appendicitis, pancreatitis

General disorders and administration site conditions: Pyrexia

Hepato-biliary disorders: Liver failure, hepatitis, autoimmune hepatitis

Immune system disorders: Sarcoidosis

Neoplasms benign, malignant and unspecified (including cysts and polyps): Merkel Cell Carcinoma (neuroendocrine carcinoma of the skin)

Nervous system disorders: Demyelinating disorders (e.g., optic neuritis, Guillain-Barré syndrome), cerebrovascular accident

Respiratory disorders: Interstitial lung disease, including pulmonary fibrosis, pulmonary embolism

Skin reactions: Stevens Johnson Syndrome, cutaneous vasculitis, erythema multiforme, new or worsening psoriasis (all sub-types including pustular and palmoplantar), alopecia, lichenoid skin reaction

Vascular disorders: Systemic vasculitis, deep vein thrombosis

7 DRUG INTERACTIONS

7.1 Methotrexate

Adalimumab has been studied in rheumatoid arthritis (RA) patients taking concomitant methotrexate (MTX). Although MTX reduced the apparent clearance of adalimumab, the data do not suggest the need for dose adjustment of either Adalimumab-aaty or MTX [see Clinical Pharmacology (12.3)].

7.2 Biological Products

In clinical studies in patients with RA, an increased risk of serious infections has been observed with the combination of TNF blockers with anakinra or abatacept, with no added benefit; therefore, use of Adalimumab-aaty with abatacept or anakinra is not recommended in patients with RA [see Warnings and Precautions (5.7, 5.11)]. A higher rate of serious infections has also been observed in patients with RA treated with rituximab who received subsequent treatment with a TNF blocker. There is insufficient information regarding the concomitant use of Adalimumab-aaty and other biologic products for the treatment of RA, PsA, AS, CD, UC, Ps, HS and UV. Concomitant administration of Adalimumab-aaty with other biologic DMARDS (e.g., anakinra and abatacept) or other TNF blockers is not recommended based upon the possible increased risk for infections and other potential pharmacological interactions.

7.3 Live Vaccines

Avoid the use of live vaccines with Adalimumab-aaty [see Warnings and Precautions (5.10)].

7.4 Cytochrome P450 Substrates

The formation of CYP450 enzymes may be suppressed by increased concentrations of cytokines (e.g., TNFα, IL-6) during chronic inflammation. It is possible for products that antagonize cytokine activity, such as adalimumab products, to influence the formation of CYP450 enzymes. Upon initiation or discontinuation of Adalimumab-aaty in patients being treated with CYP450 substrates with a narrow therapeutic index, monitoring of the effect (e.g., warfarin) or drug concentration (e.g., cyclosporine or theophylline) is recommended and the individual dose of the drug product may be adjusted as needed.

8 USE IN SPECIFIC POPULATIONS

8.1 Pregnancy

Risk Summary

Available studies with use of adalimumab during pregnancy do not reliably establish an association between adalimumab and major birth defects. Clinical data are available from the Organization of Teratology Information Specialists (OTIS)/MotherToBaby Pregnancy Registry in pregnant women with rheumatoid arthritis (RA) or Crohn's disease (CD) treated with adalimumab. Registry results showed a rate of 10% for major birth defects with first trimester use of adalimumab in pregnant women with RA or CD and a rate of 7.5% for major birth defects in the disease-matched comparison cohort. The lack of pattern of major birth defects is reassuring and differences between exposure groups may have impacted the occurrence of birth defects (see Data).

Adalimumab is actively transferred across the placenta during the third trimester of pregnancy and may affect immune response in the in-utero exposed infant (see Clinical Considerations). In an embryo-fetal perinatal development study conducted in cynomolgus monkeys, no fetal harm or malformations were observed with intravenous administration of adalimumab during organogenesis and later in gestation, at doses that produced exposures up to approximately 373 times the maximum recommended human dose (MRHD) of 40 mg subcutaneous without methotrexate (see Data).

The estimated background risk of major birth defects and miscarriage for the indicated populations is unknown. All pregnancies have a background risk of birth defect, loss, or other adverse outcomes. In the U.S. general population, the estimated background risk of major birth defects and miscarriage in clinically recognized pregnancies is 2-4% and 15-20%, respectively.

Clinical Considerations

Disease-associated maternal and embryo/fetal risk

Published data suggest that the risk of adverse pregnancy outcomes in women with RA or inflammatory bowel disease (IBD) is associated with increased disease activity. Adverse pregnancy outcomes include preterm delivery (before 37 weeks of gestation), low birth weight (less than 2500 g) infants, and small for gestational age at birth.

Fetal/Neonatal Adverse Reactions

Monoclonal antibodies are increasingly transported across the placenta as pregnancy progresses, with the largest amount transferred during the third trimester [see Data]. Risks and benefits should be considered prior to administering live or live-attenuated vaccines to infants exposed to adalimumab products in utero [see Use in Specific Populations (8.4)].

Data

Human Data

A prospective cohort pregnancy exposure registry conducted by OTIS/MotherToBaby in the U.S. and Canada between 2004 and 2016 compared the risk of major birth defects in live-born infants of 221 women (69 RA, 152 CD) treated with adalimumab during the first trimester and 106 women (74 RA, 32 CD) not treated with adalimumab.

The proportion of major birth defects among live-born infants in the adalimumab-treated and untreated cohorts was 10% (8.7% RA, 10.5% CD) and 7.5% (6.8% RA, 9.4% CD), respectively. The lack of pattern of major birth defects is reassuring and differences between exposure groups may have impacted the occurrence of birth defects. This study cannot reliably establish whether there is an association between adalimumab and major birth defects because of methodological limitations of the registry, including small sample size, the voluntary nature of the study, and the non-randomized design.

In an independent clinical study conducted in ten pregnant women with IBD treated with adalimumab, adalimumab concentrations were measured in maternal serum as well as in cord blood (n=10) and infant serum (n=8) on the day of birth. The last dose of adalimumab was given between 1 and 56 days prior to delivery. Adalimumab concentrations were 0.16-19.7 mcg/mL in cord blood, 4.28-17.7 mcg/mL in infant serum, and 0-16.1 mcg/mL in maternal serum. In all but one case, the cord blood concentration of adalimumab was higher than the maternal serum concentration, suggesting adalimumab actively crosses the placenta. In addition, one infant had serum concentrations at each of the following: 6 weeks (1.94 mcg/mL), 7 weeks (1.31 mcg/mL), 8 weeks (0.93 mcg/mL), and 11 weeks (0.53 mcg/mL), suggesting adalimumab can be detected in the serum of infants exposed in utero for at least 3 months from birth.

Animal Data

In an embryo-fetal perinatal development study, pregnant cynomolgus monkeys received adalimumab from gestation days 20 to 97 at doses that produced exposures up to 373 times that achieved with the MRHD without methotrexate (on an AUC basis with maternal IV doses up to 100 mg/kg/week). Adalimumab did not elicit harm to the fetuses or malformations.

8.2 Lactation

Risk Summary

Limited data from case reports in the published literature describe the presence of adalimumab in human milk at infant doses of 0.1% to 1% of the maternal serum concentration. Published data suggest that the systemic exposure to a breastfed infant is expected to be low because adalimumab is a large molecule and is degraded in the gastrointestinal tract. However, the effects of local exposure in the gastrointestinal tract are unknown. There are no reports of adverse effects of adalimumab products on the breastfed infant and no effects on milk production. The developmental and health benefits of breastfeeding should be considered along with the mother's clinical need for Adalimumab-aaty and any potential adverse effects on the breastfed child from Adalimumab-aaty or from the underlying maternal condition.

8.4 Pediatric Use

The safety and effectiveness of Adalimumab-aaty have not been established in pediatric patients with psoriatic arthritis, ankylosing spondylitis, or plaque psoriasis.

The safety and effectiveness of Adalimumab-aaty have been established for:

- reducing signs and symptoms of moderately to severely active polyarticular JIA in pediatric patients 2 years of age and older.
- the treatment of moderately to severely active Crohn's disease in pediatric patients 6 years of age and older.
- the treatment of moderate to severe hidradenitis suppurativa in patients 12 years of age and older.
- the treatment of non-infectious intermediate, posterior, and panuveitis in pediatric patients 2 years of age and older.

A pediatric assessment for Adalimumab-aaty demonstrates that Adalimumab-aaty is safe and effective for pediatric patients in an indication for which Humira (adalimumab) is approved. However, Adalimumab-aaty is not approved for such indication due to marketing exclusivity for Humira (adalimumab).

Due to their inhibition of TNFα, adalimumab products administered during pregnancy could affect immune response in the in utero-exposed newborn and infant. Data from eight infants exposed to adalimumab in utero suggest adalimumab crosses the placenta [see Use in Specific Populations (8.1)]. The clinical significance of elevated adalimumab concentrations in infants is unknown. The safety of administering live or live-attenuated vaccines in exposed infants is unknown. Risks and benefits should be considered prior to vaccinating (live or live-attenuated) exposed infants.

Post-marketing cases of lymphoma, including hepatosplenic T-cell lymphoma and other malignancies, some fatal, have been reported among children, adolescents, and young adults who received treatment with TNF-blockers including adalimumab products [see Warnings and Precautions (5.2)].

Juvenile Idiopathic Arthritis

The safety and effectiveness of Adalimumab-aaty for the treatment of moderately to severely active polyarticular JIA have been established in pediatric patients 2 years of age and older. Use for this indication is supported by evidence from an adequate and well-controlled study (Study JIA) of adalimumab in patients 4 to 17 years of age [see Clinical Studies (14.2)] and a safety study (Study JIA-II) of adalimumab in patients 2 to < 4 years of age where the safety profile was similar to patients 4 to 17 years of age [see Adverse Reactions (6.1)]. Adalimumab products have not been studied in patients with polyarticular JIA less than 2 years of age or in patients with a weight below 10 kg.

The safety of adalimumab in pediatric patients in the polyarticular JIA trials was generally similar to that observed in adults with certain exceptions [see Adverse Reactions (6.1)].

The safety and effectiveness of Adalimumab-aaty have not been established in pediatric patients with JIA less than 2 years of age.

Pediatric Crohn's Disease

The safety and effectiveness of Adalimumab-aaty for the treatment of moderately to severely active Crohn's disease have been established in pediatric patients 6 years of age and older. Use of Adalimumab-aaty for this indication is supported by evidence from adequate and well-controlled studies in adults with additional data from a randomized, double-blind, 52-week clinical study of two dose concentrations of adalimumab in 192 pediatric patients (6 years to 17 years of age) [see Adverse Reactions (6.1), Clinical Pharmacology (12.2, 12.3), Clinical Studies (14.6)]. The adverse reaction profile in patients 6 years to 17 years of age was similar to adults.

The safety and effectiveness of Adalimumab-aaty have not been established in pediatric patients with Crohn's disease less than 6 years of age.

Pediatric Uveitis

The safety and effectiveness of Adalimumab-aaty for the treatment of non-infectious, intermediate, posterior, and panuveitis have been established in pediatric patients 2 years of age and older. Use of Adalimumab-aaty for this indication is supported by evidence from adequate and well-controlled studies of adalimumab in adults and a 2:1 randomized, controlled clinical study of adalimumab in 90 pediatric patients [see Clinical Studies (14.11)]. The safety and effectiveness of Adalimumab-aaty have not been established in pediatric patients with uveitis less than 2 years of age.

Hidradenitis Suppurativa

Use of Adalimumab-aaty in pediatric patients 12 years of age and older for the treatment of moderate to severe HS is supported by evidence from adequate and well-controlled studies of adalimumab in adult HS patients. Additional population pharmacokinetic modeling and simulation predicted that weight-based dosing of adalimumab in pediatric patients 12 years of age and older can provide generally similar exposure to adult HS patients. The course of HS is sufficiently similar in adult and adolescent patients to allow extrapolation of data from adult to adolescent patients. The recommended dosage in pediatric patients 12 years of age or older is based on body weight [see Dosage and Administration (2.7), Clinical Pharmacology (12.3), and Clinical Studies (14.9)].

The safety and effectiveness of Adalimumab-aaty have not been established in patients less than 12 years of age with HS.

8.5 Geriatric Use

In clinical studies of RA (Studies RA-I, RA-II, RA-III, and RA-IV), a total of 519 subjects 65 years of age and older, including 107 subjects 75 years of age and older, received adalimumab. No overall difference in effectiveness was observed between these subjects and younger adult subjects.

The frequency of serious infection and malignancy among adalimumab treated subjects 65 years of age and older was higher than for those less than 65 years of age. Consider the benefits and risks of Adalimumab-aaty in patients 65 years of age and older. In patients treated with Adalimumab-aaty, closely monitor for the development of infection or malignancy [see Warnings and Precautions (5.1, 5.2)].

10 OVERDOSAGE

Doses up to 10 mg/kg have been administered to patients in clinical trials without evidence of dose-limiting toxicities. In case of overdosage, it is recommended that the patient be monitored for any signs or symptoms of adverse reactions or effects and appropriate symptomatic treatment instituted immediately.

Consider contacting the Poison Help line (1-800-222-1222) or medical toxicologist for additional overdose management recommendations.

11 DESCRIPTION

Adalimumab-aaty is a tumor necrosis factor blocker. Adalimumab-aaty is a recombinant human IgG1 monoclonal antibody created using phage display technology resulting in an antibody with human derived heavy and light chain variable regions and human IgG1:k constant regions. Adalimumab-aaty is produced by recombinant DNA technology in a mammalian cell (Chinese Hamster Ovary (CHO)) expression system and is purified by a process that includes specific viral inactivation and removal steps. It consists of 1330 amino acids and has a molecular weight of approximately 148 kilodaltons.

Adalimumab-aaty injection is supplied as a sterile, preservative-free solution for subcutaneous administration. The drug product is supplied as either a single-dose, auto-injector (Adalimumab-aaty AI), as a single-dose, 1 mL prefilled syringe with safety guard, or a single-dose, 1 mL prefilled syringe. Enclosed within the auto-injector is a single-dose, 1 mL prefilled syringe. The solution of Adalimumab-aaty is clear to opalescent, and colorless to pale brown, with a pH of about 5.2.

Each 80 mg/0.8 mL prefilled syringe or prefilled syringe with safety guard or auto-injector delivers 0.8 mL (80 mg) of drug product. Each 0.8 mL of Adalimumab-aaty contains adalimumab-aaty (80 mg), acetic acid (0.13 mg), glycine (15.02 mg), polysorbate 80 (0.8 mg), sodium acetate (0.48 mg) and Water for Injection, USP.

Each 40 mg/0.4 mL prefilled syringe or prefilled syringe with safety guard or auto-injector delivers 0.4 mL (40 mg) of drug product. Each 0.4 mL of Adalimumab-aaty contains adalimumab-aaty (40 mg), acetic acid (0.06 mg), glycine (7.51 mg), polysorbate 80 (0.4 mg), sodium acetate (0.24 mg) and Water for Injection, USP.

Each 20 mg/0.2 mL prefilled syringe delivers 0.2 mL (20 mg) of drug product. Each 0.2 mL of Adalimumab-aaty contains adalimumab-aaty (20 mg), acetic acid (0.03 mg), glycine (3.75 mg), polysorbate 80 (0.2 mg), sodium acetate (0.12 mg) and Water for Injection, USP.

12 CLINICAL PHARMACOLOGY

12.1 Mechanism of Action

Adalimumab products bind specifically to TNF-alpha and block its interaction with the p55 and p75 cell surface TNF receptors. Adalimumab products also lyse surface TNF expressing cells in vitro in the presence of complement. Adalimumab products do not bind or inactivate lymphotoxin (TNF-beta). TNF is a naturally occurring cytokine that is involved in normal inflammatory and immune responses. Elevated concentrations of TNF are found in the synovial fluid of patients with RA, JIA, PsA, and AS and play an important role in both the pathologic inflammation and the joint destruction that are hallmarks of these diseases. Increased concentrations of TNF are also found in psoriasis plaques. In Ps, treatment with Adalimumab-aaty may reduce the epidermal thickness and infiltration of inflammatory cells. The relationship between these pharmacodynamic activities and the mechanism(s) by which adalimumab products exert their clinical effects is unknown.

Adalimumab products also modulate biological responses that are induced or regulated by TNF, including changes in the concentrations of adhesion molecules responsible for leukocyte migration (ELAM-1, VCAM-1, and ICAM-1 with an IC50 of 1-2 × 10^-10 M).

12.2 Pharmacodynamics

After treatment with adalimumab, a decrease in concentrations of acute phase reactants of inflammation (C-reactive protein [CRP] and erythrocyte sedimentation rate [ESR]) and serum cytokines (IL-6) was observed compared to baseline in patients with rheumatoid arthritis. A decrease in CRP concentrations was also observed in patients with Crohn's disease, ulcerative colitis and hidradenitis suppurativa. Serum concentrations of matrix metalloproteinases (MMP-1 and MMP-3) that produce tissue remodeling responsible for cartilage destruction were also decreased after adalimumab administration.

12.3 Pharmacokinetics

The pharmacokinetics of adalimumab were linear over the dose range of 0.5 to 10 mg/kg following administration of a single intravenous dose (adalimumab products are not approved for intravenous use). Following 20, 40, and 80 mg every other week and every week subcutaneous administration, adalimumab mean serum trough concentrations at steady state increased approximately proportionally with dose in RA patients. The mean terminal half-life was approximately 2 weeks, ranging from 10 to 20 days across studies. Healthy subjects and patients with RA displayed similar adalimumab pharmacokinetics.

Adalimumab exposure in patients treated with 80 mg every other week is estimated to be comparable with that in patients treated with 40 mg every week.

Absorption

The average absolute bioavailability of adalimumab following a single 40 mg subcutaneous dose was 64%. The mean time to reach the maximum concentration was 5.5 days (131 ± 56 hours) and the maximum serum concentration was 4.7 ± 1.6 mcg/mL in healthy subjects following a single 40 mg subcutaneous administration of adalimumab.

Distribution

The distribution volume (Vss) ranged from 4.7 to 6.0 L following intravenous administration of doses ranging from 0.25 to 10 mg/kg in RA patients.

Elimination

The single dose pharmacokinetics of adalimumab in RA patients were determined in several studies with intravenous doses ranging from 0.25 to 10 mg/kg. The systemic clearance of adalimumab is approximately 12 mL/hr. In long-term studies with dosing more than two years, there was no evidence of changes in clearance over time in RA patients.

Patient Population

Rheumatoid Arthritis and Ankylosing Spondylitis: In patients receiving 40 mg adalimumab every other week, adalimumab mean steady-state trough concentrations were approximately 5 mcg/mL and 8 to 9 mcg/mL, without and with MTX concomitant treatment, respectively. Adalimumab concentrations in the synovial fluid from five rheumatoid arthritis patients ranged from 31 to 96% of those in serum. The pharmacokinetics of adalimumab in patients with AS were similar to those in patients with RA.

Psoriatic Arthritis: In patients receiving 40 mg every other week, adalimumab mean steady-state trough concentrations were 6 to 10 mcg/mL and 8.5 to 12 mcg/mL, without and with MTX concomitant treatment, respectively.

Plaque Psoriasis: Adalimumab mean steady-state trough concentration was approximately 5 to 6 mcg/mL during adalimumab 40 mg every other week treatment.

Adult Uveitis: Adalimumab mean steady concentration was approximately 8 to 10 mcg/mL during adalimumab 40 mg every other week treatment.

Adult Hidradenitis Suppurativa: Adalimumab trough concentrations were approximately 7 to 8 mcg/mL at Week 2 and Week 4, respectively, after receiving 160 mg on Week 0 followed by 80 mg on Week 2. Mean steady-state trough concentrations at Week 12 through Week 36 were approximately 7 to 11 mcg/mL during adalimumab 40 mg every week treatment.

Adult Crohn's Disease: Adalimumab mean trough concentrations were approximately 12 mcg/mL at Week 2 and Week 4 after receiving 160 mg on Week 0 followed by 80 mg on Week 2. Mean steady-state trough concentrations were 7 mcg/mL at Week 24 and Week 56 during adalimumab 40 mg every other week treatment.

Adult Ulcerative Colitis: Adalimumab mean trough concentrations were approximately 12 mcg/mL at Week 2 and Week 4 after receiving 160 mg on Week 0 followed by 80 mg on Week 2. Mean steady-state trough concentrations were approximately 8 mcg/mL and 15 mcg/mL at Week 52 after receiving a dose of adalimumab 40 mg every other week and 40 mg every week, respectively.

Anti-Drug Antibody Effects on Pharmacokinetics

Rheumatoid Arthritis: A trend toward higher apparent clearance of adalimumab in the presence of anti-adalimumab antibodies was identified.

Hidradenitis Suppurativa: In subjects with moderate to severe HS, antibodies to adalimumab were associated with reduced serum adalimumab concentrations. In general, the extent of reduction in serum adalimumab concentrations is greater with increasing titers of antibodies to adalimumab.

Specific Populations

Geriatric Patients: A lower clearance with increasing age was observed in patients with RA aged 40 to > 75 years.

Pediatric Patients:

Juvenile Idiopathic Arthritis:

- 4 years to 17 years of age: The adalimumab mean steady-state trough concentrations were 6.8 mcg/mL and 10.9 mcg/mL in patients weighing < 30 kg receiving 20 mg adalimumab subcutaneously every other week as monotherapy or with concomitant MTX, respectively. The adalimumab mean steady-state trough concentrations were 6.6 mcg/mL and 8.1 mcg/mL in patients weighing ≥ 30 kg receiving 40 mg adalimumab subcutaneously every other week as monotherapy or with MTX concomitant treatment, respectively.
- 2 years to < 4 years of age or 4 years of age and older weighing < 15 kg: The adalimumab mean steady-state trough adalimumab concentrations were 6.0 mcg/mL and 7.9 mcg/mL in patients receiving adalimumab subcutaneously every other week as monotherapy or with MTX concomitant treatment, respectively.

Pediatric Hidradenitis Suppurativa: Adalimumab concentrations in adolescent patients with HS receiving the recommended dosage regimens are predicted to be similar to those observed in adult subjects with HS based on population pharmacokinetic modeling and simulation.

Pediatric Crohn's Disease: Adalimumab mean ± SD concentrations were 15.7±6.5 mcg/mL at Week 4 following 160 mg at Week 0 and 80 mg at Week 2, and 10.5±6.0 mcg/mL at Week 52 following 40 mg every other week dosing in patients weighing ≥ 40 kg. Adalimumab mean ± SD concentrations were 10.6±6.1 mcg/mL at Week 4 following dosing 80 mg at Week 0 and 40 mg at Week 2, and 6.9±3.6 mcg/mL at Week 52 following 20 mg every other week dosing in patients weighing < 40 kg.

Male and Female Patients: No gender-related pharmacokinetic differences were observed after correction for a patient's body weight. Healthy subjects and patients with rheumatoid arthritis displayed similar adalimumab pharmacokinetics.

Patients with Renal or Hepatic Impairment: No pharmacokinetic data are available in patients with hepatic or renal impairment.

Rheumatoid factor or CRP concentrations: Minor increases in apparent clearance were predicted in RA patients receiving doses lower than the recommended dose and in RA patients with high rheumatoid factor or CRP concentrations. These increases are not likely to be clinically important.

Drug Interaction Studies:

Methotrexate: MTX reduced adalimumab apparent clearance after single and multiple dosing by 29% and 44% respectively, in patients with RA [see Drug Interactions (7.1)].

13 NONCLINICAL TOXICOLOGY

13.1 Carcinogenesis, Mutagenesis, Impairment of Fertility

Long-term animal studies of adalimumab products have not been conducted to evaluate the carcinogenic potential or its effect on fertility.

14 CLINICAL STUDIES

14.1 Clinical Studies in Rheumatoid Arthritis

The efficacy and safety of adalimumab were assessed in five randomized, double-blind studies in subjects ≥ 18 years of age with active rheumatoid arthritis (RA) diagnosed according to American College of Rheumatology (ACR) criteria. Subjects had at least 6 swollen and 9 tender joints. Adalimumab was administered subcutaneously in combination with methotrexate (MTX) (12.5 to 25 mg, Studies RA-I, RA-III and RA-V) or as monotherapy (Studies RA-II and RA-V) or with other disease-modifying anti-rheumatic drugs (DMARDs) (Study RA-IV).

Study RA-I evaluated 271 subjects who had failed therapy with at least one but no more than four DMARDs and had inadequate response to MTX. Doses of 20, 40 or 80 mg of adalimumab or placebo were given every other week for 24 weeks.

Study RA-II evaluated 544 subjects who had failed therapy with at least one DMARD. Doses of placebo, 20 or 40 mg of adalimumab were given as monotherapy every other week or weekly for 26 weeks.

Study RA-III evaluated 619 subjects who had an inadequate response to MTX. Subjects received placebo, 40 mg of adalimumab every other week with placebo injections on alternate weeks, or 20 mg of adalimumab weekly for up to 52 weeks. Study RA-III had an additional primary endpoint at 52 weeks of inhibition of disease progression (as detected by X-ray results). Upon completion of the first 52 weeks, 457 subjects enrolled in an open-label extension phase in which 40 mg of adalimumab was administered every other week for up to 5 years.

Study RA-IV assessed safety in 636 subjects who were either DMARD-naive or were permitted to remain on their pre-existing rheumatologic therapy provided that therapy was stable for a minimum of 28 days. Subjects were randomized to 40 mg of adalimumab or placebo every other week for 24 weeks.

Study RA-V evaluated 799 subjects with moderately to severely active RA of less than 3 years duration who were ≥ 18 years old and MTX naïve. Subjects were randomized to receive either MTX (optimized to 20 mg/week by week 8), adalimumab 40 mg every other week or adalimumab/MTX combination therapy for 104 weeks. Subjects were evaluated for signs and symptoms, and for radiographic progression of joint damage. The median disease duration among subjects enrolled in the study was 5 months. The median MTX dose achieved was 20 mg.

Clinical Response

The percent of adalimumab treated subjects achieving ACR 20, 50 and 70 responses in Studies RA-II and III are shown in Table 3.

Table 3. ACR Responses in Studies RA-II and RA-III (Percent of Subjects)
 | Study RA-II Monotherapy (26 weeks) |  |  | Study RA-III Methotrexate Combination (24 and 52 weeks)
Response | Placebo | Adalimumab 40 mg every other week | Adalimumab 40 mg weekly | Placebo/MTX | Adalimumab/MTX 40 mg every other week
 | N=110 | N=113 | N=103 | N=200 | N=207
ACR20
Month 6 | 19% | 46%* | 53%* | 30% | 63%*
Month 12 | NA | NA | NA | 24% | 59%*
ACR50
Month 6 | 8% | 22%* | 35%* | 10% | 39%*
Month 12 | NA | NA | NA | 10% | 42%*
ACR70
Month 6 | 2% | 12%* | 18%* | 3% | 21%*
Month 12 | NA | NA | NA | 5% | 23%*
* p<0.01, adalimumab vs. placebo

The results of Study RA-I were similar to Study RA-III; subjects receiving adalimumab 40 mg every other week in Study RA-I also achieved ACR 20, 50 and 70 response rates of 65%, 52% and 24%, respectively, compared to placebo responses of 13%, 7% and 3% respectively, at 6 months (p<0.01).

The results of the components of the ACR response criteria for Studies RA-II and RA-III are shown in Table 4. ACR response rates and improvement in all components of ACR response were maintained to week 104. Over the 2 years in Study RA-III, 20% of adalimumab subjects receiving 40 mg every other week achieved a major clinical response, defined as maintenance of an ACR 70 response over a 6-month period. ACR responses were maintained in similar proportions of subjects for up to 5 years with continuous adalimumab treatment in the open-label portion of Study RA-III.

Table 4. Components of ACR Response in Studies RA-II and RA-III
 | Study RA-II |  |  |  | Study RA-III
Parameter (median) | Placebo N=110 |  | Adalimumaba N=113 |  | Placebo/MTX N=200 |  | Adalimumaba/MTX N=207
 | Baseline | Wk 26 | Baseline | Wk 26 | Baseline | Wk 24 | Baseline | Wk 24
Number of tender joints (0-68) | 35 | 26 | 31 | 16* | 26 | 15 | 24 | 8*
Number of swollen joints (0-66) | 19 | 16 | 18 | 10* | 17 | 11 | 18 | 5*
Physician global assessmentb | 7.0 | 6.1 | 6.6 | 3.7* | 6.3 | 3.5 | 6.5 | 2.0*
Patient global assessmentb | 7.5 | 6.3 | 7.5 | 4.5* | 5.4 | 3.9 | 5.2 | 2.0*
Painb | 7.3 | 6.1 | 7.3 | 4.1* | 6.0 | 3.8 | 5.8 | 2.1*
Disability index (HAQ)c | 2.0 | 1.9 | 1.9 | 1.5* | 1.5 | 1.3 | 1.5 | 0.8*
CRP (mg/dL) | 3.9 | 4.3 | 4.6 | 1.8* | 1.0 | 0.9 | 1.0 | 0.4*
a 40 mg adalimumab administered every other week
b Visual analogue scale; 0 = best, 10 = worst
c Disability Index of the Health Assessment Questionnaire; 0 = best, 3 = worst, measures the patient’s ability to perform the following: dress/groom, arise, eat, walk, reach, grip, maintain hygiene, and maintain daily activity
* p<0.001, adalimumab vs. placebo, based on mean change from baseline

The time course of ACR 20 response for Study RA-III is shown in Figure 1.

In Study RA-III, 85% of subjects with ACR 20 responses at week 24 maintained the response at 52 weeks. The time course of ACR 20 response for Study RA-I and Study RA-II were similar.

Figure 1. Study RA-III ACR 20 Responses over 52 Weeks

In Study RA-IV, 53% of subjects treated with adalimumab 40 mg every other week plus standard of care had an ACR 20 response at week 24 compared to 35% on placebo plus standard of care (p<0.001). No unique adverse reactions related to the combination of adalimumab and other DMARDs were observed.

In Study RA-V with MTX naïve subjects with recent onset RA, the combination treatment with adalimumab plus MTX led to greater percentages of subjects achieving ACR responses than either MTX monotherapy or adalimumab monotherapy at Week 52 and responses were sustained at Week 104 (see Table 5).

Table 5. ACR Response in Study RA-V (Percent of Subjects)
Response | MTXb N=257 | Adalimumabc N=274 | Adalimumab/MTX N=268
ACR20
Week 52 | 63% | 54% | 73%
Week 104 | 56% | 49% | 69%
ACR50
Week 52 | 46% | 41% | 62%
Week 104 | 43% | 37% | 59%
ACR70
Week 52 | 27% | 26% | 46%
Week 104 | 28% | 28% | 47%
Major Clinical Responsea | 28% | 25% | 49%
a Major clinical response is defined as achieving an ACR70 response for a continuous six month period
b p<0.05, adalimumab/MTX vs. MTX for ACR 20
p<0.001, adalimumab/MTX vs. MTX for ACR 50 and 70, and Major Clinical Response
c p<0.001, adalimumab/MTX vs. adalimumab

At Week 52, all individual components of the ACR response criteria for Study RA-V improved in the adalimumab/MTX group and improvements were maintained to Week 104.

Radiographic Response

In Study RA-III, structural joint damage was assessed radiographically and expressed as change in Total Sharp Score (TSS) and its components, the erosion score and Joint Space Narrowing (JSN) score, at month 12 compared to baseline. At baseline, the median TSS was approximately 55 in the placebo and 40 mg every other week groups. The results are shown in Table 6. Adalimumab/MTX treated subjects demonstrated less radiographic progression than subjects receiving MTX alone at 52 weeks.

Table 6. Radiographic Mean Changes Over 12 Months in Study RA-III
 | Placebo/MTX | Adalimumab/MTX 40 mg every other week | Placebo/MTX-Adalimumab/MTX (95% Confidence Interval*) | P-value**
Total Sharp score | 2.7 | 0.1 | 2.6 (1.4, 3.8) | <0.001
Erosion score | 1.6 | 0.0 | 1.6 (0.9, 2.2) | <0.001
JSN score | 1.0 | 0.1 | 0.9 (0.3, 1.4) | 0.002
* 95% confidence intervals for the differences in change scores between MTX and adalimumab.
** Based on rank analysis

In the open-label extension of Study RA-III, 77% of the original subjects treated with any dose of adalimumab were evaluated radiographically at 2 years. Subjects maintained inhibition of structural damage, as measured by the TSS. Fifty-four percent had no progression of structural damage as defined by a change in the TSS of zero or less. Fifty-five percent (55%) of subjects originally treated with 40 mg adalimumab every other week have been evaluated radiographically at 5 years. Subjects had continued inhibition of structural damage with 50% showing no progression of structural damage defined by a change in the TSS of zero or less.

In Study RA-V, structural joint damage was assessed as in Study RA-III. Greater inhibition of radiographic progression, as assessed by changes in TSS, erosion score and JSN was observed in the adalimumab/MTX combination group as compared to either the MTX or adalimumab monotherapy group at Week 52 as well as at Week 104 (see Table 7).

Table 7. Radiographic Mean Change* in Study RA-V
 |  | MTXa N=257 | Adalimumaba,b N=274 | Adalimumab/MTX N=268
52 Weeks | Total Sharp score | 5.7 (4.2, 7.3) | 3.0 (1.7, 4.3) | 1.3 (0.5, 2.1)
 | Erosion score | 3.7 (2.7, 4.8) | 1.7 (1.0, 2.4) | 0.8 (0.4, 1.2)
 | JSN score | 2.0 (1.2, 2.8) | 1.3 (0.5, 2.1) | 0.5 (0.0, 1.0)
104 Weeks | Total Sharp score | 10.4 (7.7, 13.2) | 5.5 (3.6, 7.4) | 1.9 (0.9, 2.9)
 | Erosion score | 6.4 (4.6, 8.2) | 3.0 (2.0, 4.0) | 1.0 (0.4, 1.6)
 | JSN score | 4.1 (2.7, 5.4) | 2.6 (1.5, 3.7) | 0.9 (0.3, 1.5)
* mean (95% confidence interval)
a p<0.001, adalimumab/MTX vs. MTX at 52 and 104 weeks and for adalimumab/MTX vs. adalimumab at 104 weeks
b p<0.01, for adalimumab/MTX vs. adalimumab at 52 weeks

Physical Function Response

In studies RA-I through IV, adalimumab showed significantly greater improvement than placebo in the disability index of Health Assessment Questionnaire (HAQ-DI) from baseline to the end of study, and significantly greater improvement than placebo in the health-outcomes as assessed by The Short Form Health Survey (SF 36). Improvement was seen in both the Physical Component Summary (PCS) and the Mental Component Summary (MCS).

In Study RA-III, the mean (95% CI) improvement in HAQ-DI from baseline at week 52 was 0.60 (0.55, 0.65) for the adalimumab subjects and 0.25 (0.17, 0.33) for placebo/MTX (p<0.001) subjects. Sixty-three percent of adalimumab-treated subjects achieved a 0.5 or greater improvement in HAQ-DI at week 52 in the double-blind portion of the study. Eighty-two percent of these subjects maintained that improvement through week 104 and a similar proportion of subjects maintained this response through week 260 (5 years) of open-label treatment. Mean improvement in the SF-36 was maintained through the end of measurement at week 156 (3 years).

In Study RA-V, the HAQ-DI and the physical component of the SF-36 showed greater improvement (p<0.001) for the adalimumab/MTX combination therapy group versus either the MTX monotherapy or the adalimumab monotherapy group at Week 52, which was maintained through Week 104.

14.2 Clinical Studies in Juvenile Idiopathic Arthritis

The safety and efficacy of adalimumab was assessed in two studies (Studies JIA-I and JIA-II) in subjects with active polyarticular juvenile idiopathic arthritis (JIA).

Study JIA-I

The safety and efficacy of adalimumab were assessed in a multicenter, randomized, withdrawal, double-blind, parallel-group study in 171 subjects who were 4 to 17 years of age with polyarticular JIA. In the study, the subjects were stratified into two groups: MTX-treated or non-MTX-treated. All subjects had to show signs of active moderate or severe disease despite previous treatment with NSAIDs, analgesics, corticosteroids, or DMARDS. Subjects who received prior treatment with any biologic DMARDS were excluded from the study.

The study included four phases: an open-label lead in phase (OL-LI; 16 weeks), a double-blind randomized withdrawal phase (DB; 32 weeks), an open-label extension phase (OLE-BSA; up to 136 weeks), and an open-label fixed dose phase (OLE-FD; 16 weeks). In the first three phases of the study, adalimumab was administered based on body surface area at a dose of 24 mg/m^2 up to a maximum total body dose of 40 mg subcutaneously (SC) every other week. In the OLE-FD phase, the subjects were treated with 20 mg of adalimumab SC every other week if their weight was less than 30 kg and with 40 mg of adalimumab SC every other week if their weight was 30 kg or greater. Subjects remained on stable doses of NSAIDs and or prednisone (≤ 0.2 mg/kg/day or 10 mg/day maximum).

Subjects demonstrating a Pediatric ACR 30 response at the end of OL-LI phase were randomized into the double blind (DB) phase of the study and received either adalimumab or placebo every other week for 32 weeks or until disease flare. Disease flare was defined as a worsening of ≥ 30% from baseline in ≥ 3 of 6 Pediatric ACR core criteria, ≥ 2 active joints, and improvement of > 30% in no more than 1 of the 6 criteria. After 32 weeks or at the time of disease flare during the DB phase, subjects were treated in the open-label extension phase based on the BSA regimen (OLE-BSA), before converting to a fixed dose regimen based on body weight (OLE-FD phase).

Study JIA-I Clinical Response

At the end of the 16-week OL-LI phase, 94% of the subjects in the MTX stratum and 74% of the subjects in the non-MTX stratum were Pediatric ACR 30 responders. In the DB phase significantly fewer subjects who received adalimumab experienced disease flare compared to placebo, both without MTX (43% vs. 71%) and with MTX (37% vs. 65%). More subjects treated with adalimumab continued to show pediatric ACR 30/50/70 responses at Week 48 compared to subjects treated with placebo. Pediatric ACR responses were maintained for up to two years in the OLE phase in subjects who received adalimumab throughout the study.

Study JIA-II

Adalimumab was assessed in an open-label, multicenter study in 32 subjects who were 2 to < 4 years of age or 4 years of age and older weighing < 15 kg with moderately to severely active polyarticular JIA. Most subjects (97%) received at least 24 weeks of adalimumab treatment dosed 24 mg/m^2 up to a maximum of 20 mg every other week as a single SC injection up to a maximum of 120 weeks duration. During the study, most subjects used concomitant MTX, with fewer reporting use of corticosteroids or NSAIDs. The primary objective of the study was evaluation of safety [see Adverse Reactions (6.1)].

14.3 Clinical Studies in Psoriatic Arthritis

The safety and efficacy of adalimumab was assessed in two randomized, double-blind, placebo-controlled studies in 413 subjects with psoriatic arthritis (PsA). Upon completion of both studies, 383 subjects enrolled in an open-label extension study, in which 40 mg adalimumab was administered every other week.

Study PsA-I enrolled 313 adult subjects with moderately to severely active PsA (> 3 swollen and > 3 tender joints) who had an inadequate response to NSAID therapy in one of the following forms: (1) distal interphalangeal (DIP) involvement (N=23); (2) polyarticular arthritis (absence of rheumatoid nodules and presence of plaque psoriasis) (N=210); (3) arthritis mutilans (N=1); (4) asymmetric PsA (N=77); or (5) AS-like (N=2). Subjects on MTX therapy (158 of 313 subjects) at enrollment (stable dose of ≤ 30 mg/week for > 1 month) could continue MTX at the same dose. Doses of adalimumab 40 mg or placebo every other week were administered during the 24-week double-blind period of the study.

Compared to placebo, treatment with adalimumab resulted in improvements in the measures of disease activity (see Tables 8 and 9). Among subjects with PsA who received adalimumab, the clinical responses were apparent in some subjects at the time of the first visit (two weeks) and were maintained up to 88 weeks in the ongoing open-label study. Similar responses were seen in subjects with each of the subtypes of psoriatic arthritis, although few subjects were enrolled with the arthritis mutilans and ankylosing spondylitis-like subtypes. Responses were similar in subjects who were or were not receiving concomitant MTX therapy at baseline.

Subjects with psoriatic involvement of at least three percent body surface area (BSA) were evaluated for Psoriatic Area and Severity Index (PASI) responses. At 24 weeks, the proportions of subjects achieving a 75% or 90% improvement in the PASI were 59% and 42% respectively, in the adalimumab group (N=69), compared to 1% and 0% respectively, in the placebo group (N=69) (p<0.001). PASI responses were apparent in some subjects at the time of the first visit (two weeks). Responses were similar in subjects who were or were not receiving concomitant MTX therapy at baseline.

Table 8. ACR Response in Study PsA-I (Percent of Subjects)
 | Placebo N=162 | Adalimumab* N=151
ACR20
Week 12 | 14% | 58%
Week 24 | 15% | 57%
ACR50
Week 12 | 4% | 36%
Week 24 | 6% | 39%
ACR70
Week 12 | 1% | 20%
Week 24 | 1% | 23%
* p<0.001 for all comparisons between adalimumab and placebo

Table 9. Components of Disease Activity in Study PsA-I
 | Placebo N= 162 |  | Adalimumab* N=151
Parameter: median | Baseline | 24 weeks | Baseline | 24 weeks
Number of tender jointsa | 23.0 | 17.0 | 20.0 | 5.0
Number of swollen jointsb | 11.0 | 9.0 | 11.0 | 3.0
Physician global assessmentc | 53.0 | 49.0 | 55.0 | 16.0
Patient global assessmentc | 49.5 | 49.0 | 48.0 | 20.0
Painc | 49.0 | 49.0 | 54.0 | 20.0
Disability index (HAQ)d | 1.0 | 0.9 | 1.0 | 0.4
CRP (mg/dL)e | 0.8 | 0.7 | 0.8 | 0.2
* p<0.001 for adalimumab vs. placebo comparisons based on median changes
a Scale 0-78
b Scale 0-76
c Visual analog scale; 0=best, 100=worst
d Disability Index of the Health Assessment Questionnaire; 0=best, 3=worst; measures the patient’s ability to perform the following: dress/groom, arise, eat, walk, reach, grip, maintain hygiene, and maintain daily activity.
e Normal range: 0-0.287 mg/dL

Similar results were seen in an additional, 12-week study in 100 subjects with moderate to severe psoriatic arthritis who had suboptimal response to DMARD therapy as manifested by ≥ 3 tender joints and ≥ 3 swollen joints at enrollment.

Radiographic Response

Radiographic changes were assessed in the PsA studies. Radiographs of hands, wrists, and feet were obtained at baseline and Week 24 during the double-blind period when subjects were on adalimumab or placebo and at Week 48 when all subjects were on open-label adalimumab. A modified Total Sharp Score (mTSS), which included distal interphalangeal joints (i.e., not identical to the TSS used for rheumatoid arthritis), was used by readers blinded to treatment group to assess the radiographs.

Adalimumab-treated subjects demonstrated greater inhibition of radiographic progression compared to placebo-treated subjects and this effect was maintained at 48 weeks (see Table 10).

Table 10. Change in Modified Total Sharp Score in Psoriatic Arthritis
 | Placebo N=141 | Adalimumab N=133
 | Week 24 | Week 24 | Week 48
Baseline mean | 22.1 | 23.4 | 23.4
Mean Change ± SD | 0.9 ± 3.1 | -0.1 ± 1.7 | -0.2 ± 4.9*
* <0.001 for the difference between adalimumab, Week 48 and Placebo, Week 24 (primary analysis)

Physical Function Response

In Study PsA-I, physical function and disability were assessed using the HAQ Disability Index (HAQ-DI) and the SF-36 Health Survey. Subjects treated with 40 mg of adalimumab every other week showed greater improvement from baseline in the HAQ-DI score (mean decreases of 47% and 49% at Weeks 12 and 24 respectively) in comparison to placebo (mean decreases of 1% and 3% at Weeks 12 and 24 respectively). At Weeks 12 and 24, subjects treated with adalimumab showed greater improvement from baseline in the SF-36 Physical Component Summary score compared to subjects treated with placebo, and no worsening in the SF-36 Mental Component Summary score. Improvement in physical function based on the HAQ-DI was maintained for up to 84 weeks through the open-label portion of the study.

14.4 Clinical Studies in Ankylosing Spondylitis

The safety and efficacy of adalimumab 40 mg every other week was assessed in 315 adult subjects in a randomized, 24 week double-blind, placebo-controlled study in subjects with active ankylosing spondylitis (AS) who had an inadequate response to glucocorticoids, NSAIDs, analgesics, methotrexate or sulfasalazine. Active AS was defined as subjects who fulfilled at least two of the following three criteria: (1) a Bath AS disease activity index (BASDAI) score 4 cm, (2) a visual analog score (VAS) for total back pain 40 mm, and (3) morning stiffness 1 hour. The blinded period was followed by an open-label period during which subjects received adalimumab 40 mg every other week subcutaneously for up to an additional 28 weeks.

Improvement in measures of disease activity was first observed at Week 2 and maintained through 24 weeks as shown in Figure 2 and Table 11.

Responses of subjects with total spinal ankylosis (n=11) were similar to those without total ankylosis.

Figure 2. ASAS 20 Response By Visit, Study AS-I

At 12 weeks, the ASAS 20/50/70 responses were achieved by 58%, 38%, and 23%, respectively, of subjects receiving adalimumab, compared to 21%, 10%, and 5% respectively, of subjects receiving placebo (p<0.001). Similar responses were seen at Week 24 and were sustained in subjects receiving open-label adalimumab for up to 52 weeks.

A greater proportion of subjects treated with adalimumab (22%) achieved a low level of disease activity at 24 weeks (defined as a value < 20 [on a scale of 0 to 100 mm] in each of the four ASAS response parameters) compared to subjects treated with placebo (6%).

Table 11. Components of Ankylosing Spondylitis Disease Activity
 | Placebo N=107 |  | Adalimumab N=208
 | Baseline mean | Week 24 mean | Baseline mean | Week 24 mean
ASAS 20 Response Criteria*
Patient's Global Assessment of Disease Activitya* | 65 | 60 | 63 | 38
Total back pain* | 67 | 58 | 65 | 37
Inflammationb* | 6.7 | 5.6 | 6.7 | 3.6
BASFIc* | 56 | 51 | 52 | 34
BASDAId score* | 6.3 | 5.5 | 6.3 | 3.7
BASMIe score* | 4.2 | 4.1 | 3.8 | 3.3
Tragus to wall (cm) | 15.9 | 15.8 | 15.8 | 15.4
Lumbar flexion (cm) | 4.1 | 4.0 | 4.2 | 4.4
Cervical rotation (degrees) | 42.2 | 42.1 | 48.4 | 51.6
Lumbar side flexion (cm) | 8.9 | 9.0 | 9.7 | 11.7
Intermalleolar distance (cm) | 92.9 | 94.0 | 93.5 | 100.8
CRPf* | 2.2 | 2.0 | 1.8 | 0.6
a Percent of subjects with at least a 20% and 10-unit improvement measured on a Visual Analog Scale (VAS) with 0 = “none” and 100 = “severe”
b mean of questions 5 and 6 of BASDAI (defined in ‘d’)
c Bath Ankylosing Spondylitis Functional Index
d Bath Ankylosing Spondylitis Disease Activity Index
e Bath Ankylosing Spondylitis Metrology Index
f C-Reactive Protein (mg/dL)
* statistically significant for comparisons between adalimumab and placebo at Week 24

A second randomized, multicenter, double-blind, placebo-controlled study of 82 subjects with ankylosing spondylitis showed similar results.

Subjects treated with adalimumab achieved improvement from baseline in the Ankylosing Spondylitis Quality of Life Questionnaire (ASQoL) score (-3.6 vs. -1.1) and in the Short Form Health Survey (SF-36) Physical Component Summary (PCS) score (7.4 vs. 1.9) compared to placebo-treated subjects at Week 24.

14.5 Clinical Studies in Adults with Crohn's Disease

The safety and efficacy of multiple doses of adalimumab were assessed in adult subjects with moderately to severely active Crohn's disease, CD, (Crohn's Disease Activity Index (CDAI) ≥ 220 and ≤ 450) in randomized, double-blind, placebo-controlled studies. Concomitant stable doses of aminosalicylates, corticosteroids, and/or immunomodulatory agents were permitted, and 79% of subjects continued to receive at least one of these medications.

Induction of clinical remission (defined as CDAI < 150) was evaluated in two studies. In Study CD-I, 299 TNF-blocker naïve subjects were randomized to one of four treatment groups: the placebo group received placebo at Weeks 0 and 2, the 160/80 group received 160 mg adalimumab at Week 0 and 80 mg at Week 2, the 80/40 group received 80 mg at Week 0 and 40 mg at Week 2, and the 40/20 group received 40 mg at Week 0 and 20 mg at Week 2. Clinical results were assessed at Week 4.

In the second induction study, Study CD-II, 325 subjects who had lost response to, or were intolerant to, previous infliximab therapy were randomized to receive either 160 mg adalimumab at Week 0 and 80 mg at Week 2, or placebo at Weeks 0 and 2. Clinical results were assessed at Week 4.

Maintenance of clinical remission was evaluated in Study CD-III. In this study, 854 subjects with active disease received open-label adalimumab, 80 mg at week 0 and 40 mg at Week 2. Subjects were then randomized at Week 4 to 40 mg adalimumab every other week, 40 mg adalimumab every week, or placebo. The total study duration was 56 weeks. Subjects in clinical response (decrease in CDAI ≥ 70) at Week 4 were stratified and analyzed separately from those not in clinical response at Week 4.

Induction of Clinical Remission

A greater percentage of the subjects treated with 160/80 mg adalimumab achieved induction of clinical remission versus placebo at Week 4 regardless of whether the subjects were TNF blocker naïve (CD-I), or had lost response to or were intolerant to infliximab (CD-II) (see Table 12).

Table 12. Induction of Clinical Remission in Studies CD-I and CD-II (Percent of Subjects)
 | CD-I |  | CD-II
 | Placebo N=74 | Adalimumab 160/80 mg N=76 | Placebo N=166 | Adalimumab 160/80 mg N=159
Week 4
Clinical remission | 12% | 36%* | 7% | 21%*
Clinical response | 34% | 58%** | 34% | 52%**
Clinical remission is CDAI score < 150; clinical response is decrease in CDAI of at least 70 points.
* p<0.001 for adalimumab vs. placebo pairwise comparison of proportions
** p<0.01 for adalimumab vs. placebo pairwise comparison of proportions

Maintenance of Clinical Remission

In Study CD-III at Week 4, 58% (499/854) of subjects were in clinical response and were assessed in the primary analysis. At Weeks 26 and 56, greater proportions of subjects who were in clinical response at Week 4 achieved clinical remission in the adalimumab 40 mg every other week maintenance group compared to subjects in the placebo maintenance group (see Table 13). The group that received adalimumab therapy every week did not demonstrate significantly higher remission rates compared to the group that received adalimumab every other week.

Table 13. Maintenance of Clinical Remission in CD-III (Percent of Subjects)
 | Placebo | 40 mg Adalimumab every other week
 | N=170 | N=172
Week 26
Clinical remission | 17% | 40%*
Clinical response | 28% | 54%*
Week 56
Clinical remission | 12% | 36%*
Clinical response | 18% | 43%*
Clinical remission is CDAI score < 150; clinical response is decrease in CDAI of at least 70 points.
* p<0.001 for adalimumab vs. placebo pairwise comparisons of proportions

Of those in response at Week 4 who attained remission during the study, subjects in the adalimumab every other week group maintained remission for a longer time than subjects in the placebo maintenance group. Among subjects who were not in response by Week 12, therapy continued beyond 12 weeks did not result in significantly more responses.

14.6 Clinical Studies in Pediatric Subjects with Crohn's Disease

A randomized, double-blind, 52-week clinical study of 2 dose concentrations of adalimumab (Study PCD-I) was conducted in 192 pediatric subjects (6 to 17 years of age) with moderately to severely active Crohn's disease (defined as Pediatric Crohn's Disease Activity Index (PCDAI) score > 30). Enrolled subjects had over the previous two-year period an inadequate response to corticosteroids or an immunomodulator (i.e., azathioprine, 6-mercaptopurine, or methotrexate). Subjects who had previously received a TNF blocker were allowed to enroll if they had previously had loss of response or intolerance to that TNF blocker.

Subjects received open-label induction therapy at a dose based on their body weight (≥ 40 kg and < 40 kg). Subjects weighing ≥ 40 kg received 160 mg (at Week 0) and 80 mg (at Week 2). Subjects weighing < 40 kg received 80 mg (at Week 0) and 40 mg (at Week 2). At Week 4, subjects within each body weight category (≥ 40 kg and < 40 kg) were randomized 1:1 to one of two maintenance dose regimens (high dose and low dose). The high dose was 40 mg every other week for subjects weighing ≥ 40 kg and 20 mg every other week for subjects weighing < 40 kg. The low dose was 20 mg every other week for subjects weighing ≥ 40 kg and 10 mg every other week for subjects weighing < 40 kg.

Concomitant stable dosages of corticosteroids (prednisone dosage ≤ 40 mg/day or equivalent) and immunomodulators (azathioprine, 6-mercaptopurine, or methotrexate) were permitted throughout the study.

At Week 12, subjects who experienced a disease flare (increase in PCDAI of ≥ 15 from Week 4 and absolute PCDAI > 30) or who were non-responders (did not achieve a decrease in the PCDAI of ≥ 15 from baseline for 2 consecutive visits at least 2 weeks apart) were allowed to dose-escalate (i.e., switch from blinded every other week dosing to blinded every week dosing); subjects who dose-escalated were considered treatment failures.

At baseline, 38% of subjects were receiving corticosteroids, and 62% of subjects were receiving an immunomodulator. Forty-four percent (44%) of subjects had previously lost response or were intolerant to a TNF blocker. The median baseline PCDAI score was 40.

Of the 192 subjects total, 188 subjects completed the 4 week induction period, 152 subjects completed 26 weeks of treatment, and 124 subjects completed 52 weeks of treatment. Fifty-one percent (51%) (48/95) of subjects in the low maintenance dose group dose-escalated, and 38% (35/93) of subjects in the high maintenance dose group dose-escalated.

At Week 4, 28% (52/188) of subjects were in clinical remission (defined as PCDAI ≤ 10).

The proportions of subjects in clinical remission (defined as PCDAI ≤ 10) and clinical response (defined as reduction in PCDAI of at least 15 points from baseline) were assessed at Weeks 26 and 52.

At both Weeks 26 and 52, the proportion of subjects in clinical remission and clinical response was numerically higher in the high dose group compared to the low dose group (Table 14). The recommended maintenance regimen is 20 mg every other week for subjects weighing < 40 kg and 40 mg every other week for subjects weighing ≥ 40 kg. Every week dosing is not the recommended maintenance dosing regimen [see Dosage and Administration (2.3)].

Table 14. Clinical Remission and Clinical Response in Study PCD-I
 | Low Maintenance Dose† (20 or 10 mg every other week) N = 95 | High Maintenance Dose# (40 or 20 mg every other week) N = 93
Week 26
Clinical Remission‡ | 28% | 39%
Clinical Response§ | 48% | 59%
Week 52
Clinical Remission‡ | 23% | 33%
Clinical Response§ | 28% | 42%
† The low maintenance dose was 20 mg every other week for subjects weighing ≥ 40 kg and 10 mg every other week for subjects weighing < 40 kg.
# The high maintenance dose was 40 mg every other week for subjects weighing ≥ 40 kg and 20 mg every other week for subjects weighing < 40 kg.
‡ Clinical remission defined as PCDAI ≤ 10.
§ Clinical response defined as reduction in PCDAI of at least 15 points from baseline.

14.7 Clinical Studies in Adults with Ulcerative Colitis

The safety and efficacy of adalimumab were assessed in adult subjects with moderately to severely active ulcerative colitis (Mayo score 6 to 12 on a 12-point scale, with an endoscopy subscore of 2 to 3 on a scale of 0 to 3) despite concurrent or prior treatment with immunosuppressants such as corticosteroids, azathioprine, or 6-MP in two randomized, double-blind, placebo-controlled clinical studies (Studies UC-I and UC-II). Both studies enrolled TNF-blocker naïve subjects, but Study UC-II also allowed entry of subjects who lost response to or were intolerant to TNF-blockers. Forty percent (40%) of subjects enrolled in Study UC-II had previously used another TNF-blocker.

Concomitant stable doses of aminosalicylates and immunosuppressants were permitted. In Studies UC-I and II, subjects were receiving aminosalicylates (69%), corticosteroids (59%) and/or azathioprine or 6-MP (37%) at baseline. In both studies, 92% of subjects received at least one of these medications.

Induction of clinical remission (defined as Mayo score ≤ 2 with no individual subscores > 1) at Week 8 was evaluated in both studies. Clinical remission at Week 52 and sustained clinical remission (defined as clinical remission at both Weeks 8 and 52) were evaluated in Study UC-II.

In Study UC-I, 390 TNF-blocker naïve subjects were randomized to one of three treatment groups for the primary efficacy analysis. The placebo group received placebo at Weeks 0, 2, 4 and 6. The 160/80 group received 160 mg adalimumab at Week 0 and 80 mg at Week 2, and the 80/40 group received 80 mg adalimumab at Week 0 and 40 mg at Week 2. After Week 2, subjects in both adalimumab treatment groups received 40 mg every other week.

In Study UC-II, 518 subjects were randomized to receive either adalimumab 160 mg at Week 0, 80 mg at Week 2, and 40 mg every other week starting at Week 4 through Week 50, or placebo starting at Week 0 and every other week through Week 50. Corticosteroid taper was permitted starting at Week 8.

In both Studies UC-I and UC-II, a greater percentage of the subjects treated with 160/80 mg of adalimumab compared to subjects treated with placebo achieved induction of clinical remission. In Study UC-II, a greater percentage of the subjects treated with 160/80 mg of adalimumab compared to subjects treated with placebo achieved sustained clinical remission (clinical remission at both Weeks 8 and 52) (Table 15).

Table 15. Induction of Clinical Remission in Studies UC-I and UC-II and Sustained Clinical Remission in Study UC-II (Percent of Subjects)
 | Study UC-I |  |  | Study UC-II
 | Placebo N=130 | Adalimumab 160/80 mg N=130 | Treatment Difference (95% CI) | Placebo N=246 | Adalimumab 160/80 mg N=248 | Treatment Difference (95% CI)
Induction of Clinical Remission (Clinical Remission at Week 8) | 9.2% | 18.5% | 9.3%* (0.9%,17.6%) | 9.3% | 16.5% | 7.2%* (1.2%,12.9%)
Sustained Clinical Remission (Clinical Remission at both Weeks 8 and 52) | N/A | N/A | N/A | 4.1% | 8.5% | 4.4%* (0.1%, 8.6%)
Clinical remission is defined as Mayo score ≤ 2 with no individual subscores > 1.
CI=Confidence interval
* p<0.05 for adalimumab vs. placebo pairwise comparison of proportions

In Study UC-I, there was no statistically significant difference in clinical remission observed between the adalimumab 80/40 mg group and the placebo group at Week 8.

In Study UC-II, 17.3% (43/248) in the adalimumab group were in clinical remission at Week 52 compared to 8.5% (21/246) in the placebo group (treatment difference: 8.8%; 95% confidence interval (CI): [2.8%, 14.5%]; p<0.05).

In the subgroup of subjects in Study UC-II with prior TNF-blocker use, the treatment difference for induction of clinical remission appeared to be lower than that seen in the whole study population, and the treatment differences for sustained clinical remission and clinical remission at Week 52 appeared to be similar to those seen in the whole study population. The subgroup of subjects with prior TNF-blocker use achieved induction of clinical remission at 9% (9/98) in the adalimumab group versus 7% (7/101) in the placebo group and sustained clinical remission at 5% (5/98) in the adalimumab group versus 1% (1/101) in the placebo group. In the subgroup of subjects with prior TNF-blocker use, 10% (10/98) were in clinical remission at Week 52 in the adalimumab group versus 3% (3/101) in the placebo group.

14.8 Clinical Studies in Plaque Psoriasis

The safety and efficacy of adalimumab were assessed in randomized, double-blind, placebo-controlled studies in 1696 adult subjects with moderate to severe chronic plaque psoriasis (Ps) who were candidates for systemic therapy or phototherapy.

Study Ps-I evaluated 1212 subjects with chronic Ps with ≥ 10% body surface area (BSA) involvement, Physician's Global Assessment (PGA) of at least moderate disease severity, and Psoriasis Area and Severity Index (PASI) ≥ 12 within three treatment periods. In period A, subjects received placebo or adalimumab at an initial dose of 80 mg at Week 0 followed by a dose of 40 mg every other week starting at Week 1. After 16 weeks of therapy, subjects who achieved at least a PASI 75 response at Week 16, defined as a PASI score improvement of at least 75% relative to baseline, entered period B and received open-label 40 mg adalimumab every other week. After 17 weeks of open label therapy, subjects who maintained at least a PASI 75 response at Week 33 and were originally randomized to active therapy in period A were re-randomized in period C to receive 40 mg adalimumab every other week or placebo for an additional 19 weeks. Across all treatment groups the mean baseline PASI score was 19 and the baseline Physician's Global Assessment score ranged from "moderate" (53%) to "severe" (41%) to "very severe" (6%).

Study Ps-II evaluated 99 subjects randomized to adalimumab and 48 subjects randomized to placebo with chronic plaque psoriasis with ≥ 10% BSA involvement and PASI ≥ 12. Subjects received placebo, or an initial dose of 80 mg adalimumab at Week 0 followed by 40 mg every other week starting at Week 1 for 16 weeks. Across all treatment groups the mean baseline PASI score was 21 and the baseline PGA score ranged from "moderate" (41%) to "severe" (51%) to "very severe" (8%).

Studies Ps-I and II evaluated the proportion of subjects who achieved "clear" or "minimal" disease on the 6-point PGA scale and the proportion of subjects who achieved a reduction in PASI score of at least 75% (PASI 75) from baseline at Week 16 (see Table 16 and 17).

Additionally, Study Ps-I evaluated the proportion of subjects who maintained a PGA of "clear" or "minimal" disease or a PASI 75 response after Week 33 and on or before Week 52.

Table 16. Efficacy Results at 16 Weeks in Study Ps-I Number of Subjects (%)
 | Adalimumab 40 mg every other week | Placebo
 | N = 814 | N = 398
PGA: Clear or minimal* | 506 (62%) | 17 (4%)
PASI 75 | 578 (71%) | 26 (7%)
* Clear = no plaque elevation, no scale, plus or minus hyperpigmentation or diffuse pink or red coloration
Minimal = possible but difficult to ascertain whether there is slight elevation of plaque above normal skin, plus or minus surface dryness with some white coloration, plus or minus up to red coloration

Table 17. Efficacy Results at 16 Weeks in Study Ps-II Number of Subjects (%)
 | Adalimumab 40 mg every other week | Placebo
 | N = 99 | N = 48
PGA: Clear or minimal* | 70 (71%) | 5 (10%)
PASI 75 | 77 (78%) | 9 (19%)
* Clear = no plaque elevation, no scale, plus or minus hyperpigmentation or diffuse pink or red coloration
Minimal = possible but difficult to ascertain whether there is slight elevation of plaque above normal skin, plus or minus surface dryness with some white coloration, plus or minus up to red coloration

Additionally, in Study Ps-I, subjects on adalimumab who maintained a PASI 75 were re-randomized to adalimumab (N = 250) or placebo (N = 240) at Week 33. After 52 weeks of treatment with adalimumab, more subjects on adalimumab maintained efficacy when compared to subjects who were re-randomized to placebo based on maintenance of PGA of "clear" or "minimal" disease (68% vs. 28%) or a PASI 75 (79% vs. 43%).

A total of 347 stable responders participated in a withdrawal and retreatment evaluation in an open-label extension study. Median time to relapse (decline to PGA "moderate" or worse) was approximately 5 months. During the withdrawal period, no subject experienced transformation to either pustular or erythrodermic psoriasis. A total of 178 subjects who relapsed re-initiated treatment with 80 mg of adalimumab, then 40 mg every other week beginning at week 1. At week 16, 69% (123/178) of subjects had a response of PGA "clear" or "minimal".

A randomized, double-blind study (Study Ps-III) compared the efficacy and safety of adalimumab versus placebo in 217 adult subjects. Subjects in the study had to have chronic plaque psoriasis of at least moderate severity on the PGA scale, fingernail involvement of at least moderate severity on a 5-point Physician's Global Assessment of Fingernail Psoriasis (PGA-F) scale, a Modified Nail Psoriasis Severity Index (mNAPSI) score for the target-fingernail of ≥ 8, and either a BSA involvement of at least 10% or a BSA involvement of at least 5% with a total mNAPSI score for all fingernails of ≥ 20. Subjects received an initial dose of 80 mg adalimumab followed by 40 mg every other week (starting one week after the initial dose) or placebo for 26 weeks followed by open-label adalimumab treatment for an additional 26 weeks. This study evaluated the proportion of subjects who achieved "clear" or "minimal" assessment with at least a 2-grade improvement on the PGA-F scale and the proportion of subjects who achieved at least a 75% improvement from baseline in the mNAPSI score (mNAPSI 75) at Week 26.

At Week 26, a higher proportion of subjects in the adalimumab group than in the placebo group achieved the PGA-F endpoint. Furthermore, a higher proportion of subjects in the adalimumab group than in the placebo group achieved mNAPSI 75 at Week 26 (see Table 18).

Table 18. Efficacy Results at 26 Weeks
Endpoint | Adalimumab 40 mg every other week* N=109 | Placebo N=108
PGA-F: ≥ 2-grade improvement and clear or minimal | 49% | 7%
mNAPSI 75 | 47% | 3%
* Subjects received 80 mg of adalimumab at Week 0, followed by 40 mg every other week starting at Week 1.

Nail pain was also evaluated and improvement in nail pain was observed in Study Ps-III.

14.9 Clinical Studies in Hidradenitis Suppurativa

Two randomized, double-blind, placebo-controlled studies (Studies HS-I and II) evaluated the safety and efficacy of adalimumab in a total of 633 adult subjects with moderate to severe hidradenitis suppurativa (HS) with Hurley Stage II or III disease and with at least 3 abscesses or inflammatory nodules. In both studies, subjects received placebo or adalimumab at an initial dose of 160 mg at Week 0, 80 mg at Week 2, and 40 mg every week starting at Week 4 and continued through Week 11. Subjects used topical antiseptic wash daily. Concomitant oral antibiotic use was allowed in Study HS-II.

Both studies evaluated Hidradenitis Suppurativa Clinical Response (HiSCR) at Week 12. HiSCR was defined as at least a 50% reduction in total abscess and inflammatory nodule count with no increase in abscess count and no increase in draining fistula count relative to baseline (see Table 19). Reduction in HS-related skin pain was assessed using a Numeric Rating Scale in subjects who entered the study with an initial baseline score of 3 or greater on a 11-point scale.

In both studies, a higher proportion of adalimumab- than placebo-treated subjects achieved HiSCR (see Table 19).

Table 19. Efficacy Results at 12 Weeks in Subjects with Moderate to Severe Hidradenitis Suppurativa
 | HS Study I |  | HS Study II*
 | Placebo | Adalimumab 40 mg Weekly | Placebo | Adalimumab 40 mg Weekly
Hidradenitis Suppurativa Clinical Response (HiSCR) | N = 154 40 (26%) | N = 153 64 (42%) | N = 163 45 (28%) | N = 163 96 (59%)
* 19.3% of subjects in Study HS-II continued baseline oral antibiotic therapy during the study.

In both studies, from Week 12 to Week 35 (Period B), subjects who had received adalimumab were re-randomized to 1 of 3 treatment groups (adalimumab 40 mg every week, adalimumab 40 mg every other week, or placebo). Subjects who had been randomized to placebo were assigned to receive adalimumab 40 mg every week (Study HS-I) or placebo (Study HS-II).

During Period B, flare of HS, defined as ≥ 25% increase from baseline in abscesses and inflammatory nodule counts and with a minimum of 2 additional lesions, was documented in 22 (22%) of the 100 subjects who were withdrawn from adalimumab treatment following the primary efficacy timepoint in two studies.

14.10 Clinical Studies in Adults with Uveitis

The safety and efficacy of adalimumab were assessed in adult subjects with non-infectious intermediate, posterior and panuveitis excluding subjects with isolated anterior uveitis, in two randomized, double-masked, placebo-controlled studies (UV I and II). Subjects received placebo or adalimumab at an initial dose of 80 mg followed by 40 mg every other week starting one week after the initial dose. The primary efficacy endpoint in both studies was ´time to treatment failure´.

Treatment failure was a multi-component outcome defined as the development of new inflammatory chorioretinal and/or inflammatory retinal vascular lesions, an increase in anterior chamber (AC) cell grade or vitreous haze (VH) grade or a decrease in best corrected visual acuity (BCVA).

Study UV I evaluated 217 subjects with active uveitis while being treated with corticosteroids (oral prednisone at a dose of 10 to 60 mg/day). All subjects received a standardized dose of prednisone 60 mg/day at study entry followed by a mandatory taper schedule, with complete corticosteroid discontinuation by Week 15.

Study UV II evaluated 226 subjects with inactive uveitis while being treated with corticosteroids (oral prednisone 10 to 35 mg/day) at baseline to control their disease. Subjects subsequently underwent a mandatory taper schedule, with complete corticosteroid discontinuation by Week 19.

Clinical Response

Results from both studies demonstrated statistically significant reduction of the risk of treatment failure in subjects treated with adalimumab versus subjects receiving placebo. In both studies, all components of the primary endpoint contributed cumulatively to the overall difference between adalimumab and placebo groups (Table 20).

Table 20. Time to Treatment Failure in Studies UV I and UV II
 | UV I |  |  | UV II
 | Placebo (N = 107) | Adalimumab (N = 110) | HR [95% CI]a | Placebo (N = 111) | Adalimumab (N = 115) | HR [95% CI]a
Failureb n (%) | 84 (78.5) | 60 (54.5) | 0.50 [0.36, 0.70] | 61 (55.0) | 45 (39.1) | 0.57 [0.39, 0.84]
Median Time to Failure (Months) [95% CI] | 3.0 [2.7, 3.7] | 5.6 [3.9, 9.2] | N/A | 8.3 [4.8, 12.0] | NEc | N/A
b HR of adalimumab versus placebo from proportional hazards regression with treatment as factor.
b Treatment failure at or after Week 6 in Study UV I, or at or after Week 2 in Study UV II, was counted as event. Subjects who discontinued the study were censored at the time of dropping out.
c NE = not estimable. Fewer than half of at-risk subjects had an event.

Figure 3: Kaplan-Meier Curves Summarizing Time to Treatment Failure on or after Week6 (Study UV I) or Week 2 (Study UV II)

Study UV I

Study UV II

Note: P# = Placebo (Number of Events/Number at Risk); A# = Adalimumab (Number of Events/Number at Risk).

14.11 Clinical Studies in Pediatric Subjects with Uveitis

The safety and efficacy of adalimumab were assessed in a randomized, double-masked, placebo-controlled study of 90 pediatric subjects from 2 to < 18 years of age with active JIA-associated non-infectious uveitis (PUV-I). Subjects received either placebo or 20 mg adalimumab (if < 30 kg) or 40 mg adalimumab (if 30 kg) every other week in combination with a dose of methotrexate. Concomitant dosages of corticosteroids were permitted at study entry followed by a mandatory reduction in topical corticosteroids within 3 months.

The primary endpoint was time to treatment failure. The criteria determining treatment failure were worsening or sustained non-improvement in ocular inflammation, or worsening of ocular co-morbidities.

Clinical Response

Adalimumab significantly decreased the risk of treatment failure by 75% relative to placebo (HR = 0.25 [95% CI: 0.12, 0.49]) (Table 21).

Table 21. Analysis Results of Time to Treatment Failure (Study PUV-I)
 | Placebo (N=30) | Adalimumab (N=60) | HR (95% CI)a
Failure (n[%]) | 18 (60%) | 16 (26.7%) | 0.25 (0.12, 0.49)
Median Time to Failure (Weeks) (95% CI)b | 24.1 (12.4, 81.0) | NEc
a HR of adalimumab versus placebo from proportional hazards regression with treatment as factor.
b Estimated based on Kaplan-Meier curve.
c NE = not estimable. Fewer than half of at-risk subjects had an event.

Figure 4: Kaplan-Meier Curves Summarizing Time to Treatment Failure (Study PUV-I)

Study PUV-I

Note: P# = Placebo (Number of Events/Number at Risk); A# = Adalimumab (Number of Events/Number at Risk).

15 REFERENCES

1. National Cancer Institute. Surveillance, Epidemiology, and End Results Database (SEER) Program. SEER Incidence Crude Rates, 17 Registries, 2000-2007.

16 HOW SUPPLIED/STORAGE AND HANDLING

Adalimumab-aaty is supplied as a preservative-free, sterile, clear to opalescent, and colorless to pale brown solution for subcutaneous administration. The following packaging configurations are available.

- Adalimumab-aaty AI Carton - 40 mg/0.4 mL (1 Count)
  Adalimumab-aaty is supplied in a carton containing two alcohol preps and one dose tray. The dose tray consists of a single-dose prefilled auto-injector, containing a 1 mL prefilled syringe with a fixed thin wall, ½ inch needle, providing 40 mg/0.4 mL of Adalimumab-aaty. The NDC number is 72606-022-09.
- Adalimumab-aaty AI Carton - 40 mg/0.4 mL (2 Count)
  Adalimumab-aaty is supplied in a carton containing two alcohol preps and two dose trays. Each dose tray consists of a single-dose prefilled auto-injector, containing a 1 mL prefilled syringe with a fixed thin wall, ½ inch needle, providing 40 mg/0.4 mL of Adalimumab-aaty. The NDC number is 72606-022-10.
- Adalimumab-aaty AI Carton - 40 mg/0.4 mL (4 Count)
  Adalimumab-aaty is supplied in a carton containing four alcohol preps and four dose trays. Each dose tray consists of a single-dose prefilled auto-injector, containing a 1 mL prefilled syringe with a fixed thin wall, ½ inch needle, providing 40 mg/0.4 mL of Adalimumab-aaty. The NDC number is 72606-022-11.
- Adalimumab-aaty AI Carton - 40 mg/0.4 mL (6 Count)
  Adalimumab-aaty is supplied in a carton containing six alcohol preps and six dose trays. Each dose tray consists of a single-dose prefilled auto-injector, containing a 1 mL prefilled syringe with a fixed thin wall, ½ inch needle, providing 40 mg/0.4 mL of Adalimumab-aaty. The NDC number is 72606-022-12.
- Prefilled Syringe with Safety Guard Carton - 40 mg/0.4 mL (1 Count)
  Adalimumab-aaty is supplied in a carton containing two alcohol preps and one dose tray. The dose tray consists of a single-dose prefilled syringe with safety guard, containing a 1 mL prefilled syringe with a fixed thin wall, ½ inch needle, providing 40 mg/0.4 mL of Adalimumab-aaty. The NDC number is 72606-022-05.
- Prefilled Syringe with Safety Guard Carton - 40 mg/0.4 mL (2 Count)
  Adalimumab-aaty is supplied in a carton containing two alcohol preps and two dose trays. Each dose tray consists of a single-dose prefilled syringe with safety guard, containing a 1 mL prefilled syringe with a fixed thin wall, ½ inch needle, providing 40 mg/0.4 mL of Adalimumab-aaty. The NDC number is 72606-022-06.
- Prefilled Syringe with Safety Guard Carton - 40 mg/0.4 mL (4 Count)
  Adalimumab-aaty is supplied in a carton containing four alcohol preps and four dose trays. Each dose tray consists of a single-dose prefilled syringe with safety guard, containing a 1 mL prefilled syringe with a fixed thin wall, ½ inch needle, providing 40 mg/0.4 mL of Adalimumab-aaty. The NDC number is 72606-022-07.
- Prefilled Syringe with Safety Guard Carton - 40 mg/0.4 mL (6 Count)
  Adalimumab-aaty is supplied in a carton containing six alcohol preps and six dose trays. Each dose tray consists of a single-dose prefilled syringe with safety guard, containing a 1 mL prefilled syringe with a fixed thin wall, ½ inch needle, providing 40 mg/0.4 mL of Adalimumab-aaty. The NDC number is 72606-022-08.
- Prefilled Syringe Carton - 40 mg/0.4 mL (1 Count)
  Adalimumab-aaty is supplied in a carton containing two alcohol preps and one dose tray. The dose tray consists of a single-dose prefilled syringe, containing a 1 mL prefilled syringe with a fixed thin wall, ½ inch needle, providing 40 mg/0.4 mL of Adalimumab-aaty. The NDC number is 72606-022-01.
- Prefilled Syringe Carton - 40 mg/0.4 mL (2 Count)
  Adalimumab-aaty is supplied in a carton containing two alcohol preps and two dose trays. Each dose tray consists of a single-dose prefilled syringe, containing a 1 mL prefilled syringe with a fixed thin wall, ½ inch needle, providing 40 mg/0.4 mL of Adalimumab-aaty. The NDC number is 72606-022-02.
- Prefilled Syringe Carton - 40 mg/0.4 mL (4 Count)
  Adalimumab-aaty is supplied in a carton containing four alcohol preps and four dose trays. Each dose tray consists of a single-dose prefilled syringe, containing a 1 mL prefilled syringe with a fixed thin wall, ½ inch needle, providing 40 mg/0.4 mL of Adalimumab-aaty. The NDC number is 72606-022-03.
- Prefilled Syringe Carton - 40 mg/0.4 mL (6 Count)
  Adalimumab-aaty is supplied in a carton containing six alcohol preps and six dose trays. Each dose tray consists of a single-dose prefilled syringe, containing a 1 mL prefilled syringe with a fixed thin wall, ½ inch needle, providing 40 mg/0.4 mL of Adalimumab-aaty. The NDC number is 72606-022-04.
- Adalimumab-aaty AI Carton - 80 mg/0.8 mL (1 Count)
  Adalimumab-aaty is supplied in a carton containing two alcohol preps and one dose tray. The dose tray consists of a single-dose prefilled auto-injector, containing a 1 mL prefilled syringe with a fixed thin wall, ½ inch needle, providing 80 mg/0.8 mL of Adalimumab-aaty. The NDC number is 72606-040-04.
- Adalimumab-aaty AI Carton - 80 mg/0.8 mL (2 Count)
  Adalimumab-aaty is supplied in a carton containing two alcohol preps and two dose trays. Each dose tray consists of a single-dose prefilled auto-injector, containing a 1 mL prefilled syringe with a fixed thin wall, ½ inch needle, providing 80 mg/0.8 mL of Adalimumab-aaty. The NDC number is 72606-040-05.
- Prefilled Syringe with Safety Guard Carton - 80 mg/0.8 mL (1 Count)
  Adalimumab-aaty is supplied in a carton containing two alcohol preps and one dose tray. The dose tray consists of a single-dose prefilled syringe with safety guard, containing a 1 mL prefilled syringe with a fixed thin wall, ½ inch needle, providing 80 mg/0.8 mL of Adalimumab-aaty. The NDC number is 72606-040-02.
- Prefilled Syringe with Safety Guard Carton - 80 mg/0.8 mL (2 Count)
  Adalimumab-aaty is supplied in a carton containing two alcohol preps and two dose trays. Each dose tray consists of a single-dose prefilled syringe with safety guard, containing a 1 mL prefilled syringe with a fixed thin wall, ½ inch needle, providing 80 mg/0.8 mL of Adalimumab-aaty. The NDC number is 72606-040-03.
- Prefilled Syringe Carton - 80 mg/0.8 mL (1 Count)
  Adalimumab-aaty is supplied in a carton containing two alcohol preps and one dose tray. The dose tray consists of a single-dose prefilled syringe, containing a 1 mL prefilled syringe with a fixed thin wall, ½ inch needle, providing 80 mg/0.8 mL of Adalimumab-aaty. The NDC number is 72606-040-01.
- Prefilled Syringe Carton - 20 mg/0.2 mL (2 Count)
  Adalimumab-aaty is supplied in a carton containing two alcohol preps and two dose trays. Each dose tray consists of a single-dose prefilled syringe, containing a 1 mL prefilled syringe with a fixed thin wall, ½ inch needle, providing 20 mg/0.2 mL of Adalimumab-aaty. The NDC number is 72606-041-01.
- Adalimumab-aaty AI 80 mg/0.8 mL - Crohn's Disease, Ulcerative Colitis or HIdradenitis Suppurativa Starter Package (3 Count)
  Adalimumab-aaty is supplied in a carton containing four alcohol preps and three dose trays (Crohn’s Disease Starter Package). Each dose tray consists of a single-dose prefilled auto-injector, containing a 1 mL prefilled syringe with a fixed thin wall, ½ inch needle, providing 80 mg/0.8 mL of Adalimumab aaty. The NDC number is 72606-040-06.

Storage and Stability

Do not use beyond the expiration date on the container. Adalimumab-aaty must be refrigerated at 36°F to 46°F (2°C to 8°C). DO NOT FREEZE. Do not use if frozen even if it has been thawed.

Store in original carton until time of administration to protect from light. Do not shake.

If needed, for example when traveling, Adalimumab-aaty may be stored at room temperature up to a maximum of 77°F (25°C) for a period of up to 31 days, with protection from light. Adalimumab-aaty should be discarded if not used within the 31-day period. Record the date when Adalimumab-aaty is first removed from the refrigerator in the spaces provided on the carton and dose pack.

Do not store Adalimumab-aaty in extreme heat or cold.

17 PATIENT COUNSELING INFORMATION

Advise the patient or caregiver to read the FDA-approved patient labeling (Medication Guide and Instructions for Use).

Infections

Inform patients that Adalimumab-aaty may lower the ability of their immune system to fight infections. Instruct patients of the importance of contacting their doctor if they develop any symptoms of infection, including tuberculosis, invasive fungal infections, and reactivation of hepatitis B virus infections [see Warnings and Precautions (5.1, 5.2, 5.4)].

Malignancies

Counsel patients about the risk of malignancies while receiving Adalimumab-aaty [see Warnings and Precautions (5.2)].

Hypersensitivity Reactions

Advise patients to seek immediate medical attention if they experience any symptoms of severe hypersensitivity reactions. [see Warnings and Precautions (5.3)].

Other Medical Conditions

Advise patients to report any signs of new or worsening medical conditions such as congestive heart failure, neurological disease, autoimmune disorders, or cytopenias. Advise patients to report any symptoms suggestive of a cytopenia such as bruising, bleeding, or persistent fever [see Warnings and Precautions (5.5, 5.6, 5.8, 5.9)].

Instructions on Injection Technique

Inform patients that the first injection is to be performed under the supervision of a qualified health care professional. If a patient or caregiver is to administer Adalimumab-aaty, instruct them in injection techniques and assess their ability to inject subcutaneously to ensure the proper administration of Adalimumab-aaty [see Instructions for Use].

For patients who will use the Adalimumab-aaty AI, tell them that they:

- May hear a 1st loud "click" when they place the auto-injector straight on their skin and push the entire device down firmly. The click means the start of the injection.
- Must keep holding the Adalimumab-aaty AI against their skin until all of the medicine is injected.
- Will know that the injection has finished when the blue plunger rod fills the medication window and stops moving. Also they may hear a 2nd loud "click" several seconds after starting the injection. Then, count slowly to 5 to ensure full dose has been given.

Instruct patients to dispose of their used needles and syringes or used auto-injector in a FDA-cleared sharps disposal container immediately after use. Instruct patients not to dispose of loose needles and syringes or auto-injector in their household trash. Instruct patients that if they do not have a FDA-cleared sharps disposal container, they may use a household container that is made of a heavy-duty plastic, can be closed with a tight-fitting and puncture-resistant lid without sharps being able to come out, upright and stable during use, leak-resistant, and properly labeled to warn of hazardous waste inside the container.

Instruct patients that when their sharps disposal container is almost full, they will need to follow their community guidelines for the correct way to dispose of their sharps disposal container. Instruct patients that there may be state or local laws regarding disposal of used needles and syringes. Refer patients to the FDA's website at http://www.fda.gov/safesharpsdisposal for more information about safe sharps disposal, and for specific information about sharps disposal in the state that they live in.

Instruct patients not to dispose of their used sharps disposal container in their household trash unless their community guidelines permit this. Instruct patients not to recycle their used sharps disposal container.

Adalimumab-aaty

Manufactured by:
CELLTRION, Inc.
23, Academy-ro, Yeonsu-gu,
Incheon, 22014, Republic of Korea
US License Number 1996

Distributed by:
CELLTRION USA, Inc.
One Evertrust Plaza Suite 1207
Jersey City, NJ 07302

MEDICATION GUIDE
Adalimumab-aaty (ada-LIM-u-mab aaty)
injection, for subcutaneous use
This product is YUFLYMA (adalimumab-aaty).

Read the Medication Guide that comes with Adalimumab-aaty before you start taking it and each time you get a refill. There may be new information. This Medication Guide does not take the place of talking with your doctor about your medical condition or treatment.

What is the most important information I should know about Adalimumab-aaty?
Adalimumab-aaty is a medicine that affects your immune system. Adalimumab-aaty can lower the ability of your immune system to fight infections. Serious infections have happened in people taking adalimumab products. These serious infections include tuberculosis (TB) and infections caused by viruses, fungi or bacteria that have spread throughout the body. Some people have died from these infections.

- Your doctor should test you for TB before starting Adalimumab-aaty.
- Your doctor should check you closely for signs and symptoms of TB during treatment with Adalimumab-aaty.

You should not start taking Adalimumab-aaty if you have any kind of infection unless your doctor says it is okay.
Before starting Adalimumab-aaty, tell your doctor if you:

- think you have an infection or have symptoms of infection such as:

- fever, sweats, or chills
- muscle aches
- cough
- shortness of breath
- blood in phlegm

- warm, red, or painful skin or sores on your body
- diarrhea or stomach pain
- burning when you urinate or urinate more often than normal
- feel very tired
- weight loss

- are being treated for an infection.
- get a lot of infections or have infections that keep coming back.
- have diabetes.
- have TB, or have been in close contact with someone with TB.
- were born in, lived in, or traveled to countries where there is more risk for getting TB. Ask your doctor if you are not sure.
- live or have lived in certain parts of the country (such as the Ohio and Mississippi River valleys) where there is an increased risk for getting certain kinds of fungal infections (histoplasmosis, coccidioidomycosis, or blastomycosis). These infections may happen or become more severe if you use Adalimumab-aaty. Ask your doctor if you do not know if you have lived in an area where these infections are common.
- have or have had hepatitis B.
- use the medicine ORENCIA® (abatacept), KINERET® (anakinra), RITUXAN® (rituximab), IMURAN® (azathioprine), or PURINETHOL® (6–mercaptopurine, 6-MP).
- are scheduled to have major surgery.

After starting Adalimumab-aaty, call your doctor right away if you have an infection, or any sign of an infection.
Adalimumab-aaty can make you more likely to get infections or make any infection that you may have worse.
Cancer

- For children and adults taking Tumor Necrosis Factor (TNF)-blockers, including Adalimumab-aaty, the chances of getting cancer may increase.
- There have been cases of unusual cancers in children, teenagers, and young adults using TNF-blockers.
- People with rheumatoid arthritis (RA), especially more serious RA, may have a higher chance for getting a kind of cancer called lymphoma.
- If you use TNF blockers including Adalimumab-aaty, your chance of getting two types of skin cancer may increase (basal cell cancer and squamous cell cancer of the skin). These types of cancer are generally not life-threatening if treated. Tell your doctor if you have a bump or open sore that does not heal.
- Some people receiving TNF blockers including Adalimumab-aaty developed a rare type of cancer called hepatosplenic T-cell lymphoma. This type of cancer often results in death. Most of these people were male teenagers or young men. Also, most people were being treated for Crohn's disease or ulcerative colitis with another medicine called IMURAN® (azathioprine) or PURINETHOL® (6-mercaptopurine, 6–MP).

What is Adalimumab-aaty?
Adalimumab-aaty is a medicine called a Tumor Necrosis Factor (TNF) blocker. Adalimumab-aaty is used:

- To reduce the signs and symptoms of:
  - moderate to severe RA in adults. Adalimumab-aaty can be used alone, with methotrexate, or with certain other medicines.
  - moderate to severe polyarticular juvenile idiopathic arthritis (JIA) in children 2 years and older. Adalimumab-aaty can be used alone or with methotrexate.
  - psoriatic arthritis (PsA) in adults. Adalimumab-aaty can be used alone or with certain other medicines.
  - ankylosing spondylitis (AS) in adults.
  - moderate to severe hidradenitis suppurativa (HS) in people 12 years and older.
- To treat moderate to severe Crohn's disease (CD) in adults and children 6 years of age and older.
- To treat moderate to severe ulcerative colitis (UC) in adults. It is not known if adalimumab products are effective in people who stopped responding to or could not tolerate TNF-blocker medicines.
- To treat moderate to severe chronic (lasting a long time) plaque psoriasis (Ps) in adults who have the condition in many areas of their body and who may benefit from taking injections or pills (systemic therapy) or phototherapy (treatment using ultraviolet light alone or with pills).
- To treat non-infectious intermediate, posterior, and panuveitis in adults and children 2 years of age and older.

What should I tell my doctor before taking Adalimumab-aaty?
Adalimumab-aaty may not be right for you. Before starting Adalimumab-aaty, tell your doctor about all of your medical conditions, including if you:

- have an infection. See "What is the most important information I should know about Adalimumab-aaty?"
- have or have had cancer.
- have any numbness or tingling or have a disease that affects your nervous system such as multiple sclerosis or Guillain-Barré syndrome.
- have or had heart failure.
- have recently received or are scheduled to receive a vaccine. You may receive vaccines, except for live vaccines while using Adalimumab-aaty. Children should be brought up to date with all vaccines before starting Adalimumab-aaty.
- are allergic to Adalimumab-aaty or to any of its ingredients. See the end of this Medication Guide for a list of ingredients in Adalimumab-aaty.
- are pregnant or plan to become pregnant, breastfeeding or plan to breastfeed. You and your doctor should decide if you should take Adalimumab-aaty while you are pregnant or breastfeeding.
- have a baby and you were using Adalimumab-aaty during your pregnancy. Tell your baby's doctor before your baby receives any vaccines.

Tell your doctor about all the medicines you take, including prescription and over-the-counter medicines, vitamins, and herbal supplements.
Especially tell your doctor if you use:

- ORENCIA® (abatacept), KINERET® (anakinra), REMICADE® (infliximab), ENBREL® (etanercept), CIMZIA® (certolizumab pegol) or SIMPONI® (golimumab), because you should not use Adalimumab-aaty while you are also using one of these medicines.
- RITUXAN® (rituximab). Your doctor may not want to give you Adalimumab-aaty if you have received RITUXAN® (rituximab) recently.
- IMURAN® (azathioprine) or PURINETHOL® (6–mercaptopurine, 6-MP).

Keep a list of your medicines with you to show your doctor and pharmacist each time you get a new medicine.

How should I take Adalimumab-aaty?

- Adalimumab-aaty is given by an injection under the skin. Your doctor will tell you how often to take an injection of Adalimumab-aaty. This is based on your condition to be treated. Do not inject Adalimumab-aaty more often than you were prescribed.
- See the Instructions for Use inside the carton for complete instructions for the right way to prepare and inject Adalimumab-aaty.
- Make sure you have been shown how to inject Adalimumab-aaty before you do it yourself. You can call your doctor or 1-877-888-4231 if you have any questions about giving yourself an injection. Someone you know can also help you with your injection after they have been shown how to prepare and inject Adalimumab-aaty.
- Do not try to inject Adalimumab-aaty yourself until you have been shown the right way to give the injections. If your doctor decides that you or a caregiver may be able to give your injections of Adalimumab-aaty at home, you should receive training on the right way to prepare and inject Adalimumab-aaty.
- Do not miss any doses of Adalimumab-aaty unless your doctor says it is okay. If you forget to take Adalimumab-aaty, inject a dose as soon as you remember. Then, take your next dose at your regular scheduled time. This will put you back on schedule. In case you are not sure when to inject Adalimumab-aaty, call your doctor or pharmacist.
- If you take more Adalimumab-aaty than you were told to take, call your doctor.

What are the possible side effects of Adalimumab-aaty?
Adalimumab-aaty can cause serious side effects, including:
See "What is the most important information I should know about Adalimumab-aaty?"

- Serious Infections.
  Your doctor will examine you for TB and perform a test to see if you have TB. If your doctor feels that you are at risk for TB, you may be treated with medicine for TB before you begin treatment with Adalimumab-aaty and during treatment with Adalimumab-aaty. Even if your TB test is negative your doctor should carefully monitor you for TB infections while you are taking Adalimumab-aaty. People who had a negative TB skin test before receiving adalimumab products have developed active TB. Tell your doctor if you have any of the following symptoms while taking or after taking Adalimumab-aaty:

- cough that does not go away
- low grade fever

- weight loss
- loss of body fat and muscle (wasting)

- Hepatitis B infection in people who carry the virus in their blood.
  If you are a carrier of the hepatitis B virus (a virus that affects the liver), the virus can become active while you use Adalimumab-aaty. Your doctor should do blood tests before you start treatment, while you are using Adalimumab-aaty, and for several months after you stop treatment with Adalimumab-aaty. Tell your doctor if you have any of the following symptoms of a possible hepatitis B infection:

- muscle aches
- feel very tired
- dark urine
- skin or eyes look yellow
- little or no appetite
- vomiting

- clay-colored bowel movements
- fever
- chills
- stomach discomfort
- skin rash

- Allergic reactions. Allergic reactions can happen in people who use Adalimumab-aaty. Call your doctor or get medical help right away if you have any of these symptoms of a serious allergic reaction:

- hives
- trouble breathing

- swelling of your face, eyes, lips or mouth

- Nervous system problems. Signs and symptoms of a nervous system problem include: numbness or tingling, problems with your vision, weakness in your arms or legs, and dizziness.
- Blood problems. Your body may not make enough of the blood cells that help fight infections or help to stop bleeding. Symptoms include a fever that does not go away, bruising or bleeding very easily, or looking very pale.
- New heart failure or worsening of heart failure you already have. Call your doctor right away if you get new worsening symptoms of heart failure while taking Adalimumab-aaty, including:

- shortness of breath
- sudden weight gain

- swelling of your ankles or feet

- Immune reactions including a lupus-like syndrome. Symptoms include chest discomfort or pain that does not go away, shortness of breath, joint pain, or a rash on your cheeks or arms that gets worse in the sun. Symptoms may improve when you stop Adalimumab-aaty.
- Liver Problems. Liver problems can happen in people who use TNF-blocker medicines. These problems can lead to liver failure and death. Call your doctor right away if you have any of these symptoms:

- feel very tired
- poor appetite or vomiting

- skin or eyes look yellow
- pain on the right side of your stomach (abdomen)

- Psoriasis. Some people using adalimumab products had new psoriasis or worsening of psoriasis they already had. Tell your doctor if you develop red scaly patches or raised bumps that are filled with pus. Your doctor may decide to stop your treatment with Adalimumab-aaty.

Call your doctor or get medical care right away if you develop any of the above symptoms. Your treatment with Adalimumab-aaty may be stopped.
The most common side effects of Adalimumab-aaty include:

- injection site reactions: redness, rash, swelling, itching, or bruising. These symptoms usually will go away within a few days. Call your doctor right away if you have pain, redness or swelling around the injection site that does not go away within a few days or gets worse.
- upper respiratory infections (including sinus infections)
- headaches
- rash

These are not all the possible side effects with Adalimumab-aaty. Tell your doctor if you have any side effect that bothers you or that does not go away. Ask your doctor or pharmacist for more information.
Call your doctor for medical advice about side effects. You may report side effects to the FDA at 1-800-FDA-1088.

How should I store Adalimumab-aaty?

- Store Adalimumab-aaty in the refrigerator at 36°F to 46°F (2°C to 8°C). Store Adalimumab-aaty in the original carton until use to protect it from light. Do not shake.
- Do not freeze Adalimumab-aaty. Do not use Adalimumab-aaty if frozen, even if it has been thawed.
- Refrigerated Adalimumab-aaty may be used until the expiration date printed on the Adalimumab-aaty carton, dose pack, auto-injector or prefilled syringe. Do not use Adalimumab-aaty after the expiration date.
- If needed, for example when you are traveling, you may also store Adalimumab-aaty at room temperature up to 77°F (25°C) for up to 31 days. Store Adalimumab-aaty in the original carton until use to protect it from light.
- Throw away Adalimumab-aaty if it has been kept at room temperature and not been used within 31 days.
- Record the date you first remove Adalimumab-aaty from the refrigerator in the spaces provided on the carton and dose pack.
- Do not store Adalimumab-aaty in extreme heat or cold.
- Do not use an auto-injector or prefilled syringe if the liquid is cloudy, discolored, or has flakes or particles in it.
- Do not drop or crush Adalimumab-aaty. The prefilled syringe is glass.

Keep Adalimumab-aaty, injection supplies, and all other medicines out of the reach of children.

General information about the safe and effective use of Adalimumab-aaty
Medicines are sometimes prescribed for purposes other than those listed in a Medication Guide. Do not use Adalimumab-aaty for a condition for which it was not prescribed. Do not give Adalimumab-aaty to other people, even if they have the same condition. It may harm them.
This Medication Guide summarizes the most important information about Adalimumab-aaty. If you would like more information, talk with your doctor. You can ask your doctor or pharmacist for information about Adalimumab-aaty that is written for health professionals.

What are the ingredients in Adalimumab-aaty?
Active ingredient: adalimumab-aaty
Adalimumab-aaty AI 40 mg/0.4 mL, Adalimumab-aaty 40 mg/0.4 mL prefilled syringe with safety guard, and Adalimumab-aaty 40 mg/0.4 mL prefilled syringe, Adalimumab-aaty AI 80 mg/0.8 mL, Adalimumab-aaty 80 mg/0.8 mL prefilled syringe with safety guard, Adalimumab-aaty 80 mg/0.8 mL prefilled syringe, and Adalimumab-aaty 20 mg/0.2 mL prefilled syringe:
Inactive ingredients: acetic acid, glycine, polysorbate 80, sodium acetate, and Water for Injection, USP.
Manufactured by: CELLTRION, Inc., 23, Academy-ro, Yeonsu-gu, Incheon, 22014, Republic of Korea
US License Number 1996
Distributed by: CELLTRION USA, Inc., One Evertrust Plaza, Suite 1207, Jersey City, NJ 07302, USA

This Medication Guide has been approved by the U.S. Food and Drug Administration.

Revised: 10/2025

INSTRUCTIONS FOR USE Adalimumab-aaty (ada-LIM-u-mab aaty) injection, for subcutaneous use 80 mg/0.8 mL, 40 mg/0.4 mL Single-Dose Auto-injector This product is YUFLYMA (adalimumab-aaty).

For subcutaneous use only

Read and follow the Instructions for Use that come with your Adalimumab-aaty Auto-injector before you start using it and each time you get a refill. There may be new information. This information does not take the place of talking to your doctor about your medical condition or treatment.

Figure A: Parts of Adalimumab-aaty Auto-injector

Important Information

- Use the Auto-injector only if your doctor has trained you on the right way to prepare for and to give an injection.
- Ask your doctor how often you will need to give an injection.
- Do not shake the Auto-injector at any time.
- Do not remove the Cap until you are ready to inject.
- Do not share the Auto-injector with anyone.

How to store the Auto-injector

- Store the Auto-injector in a refrigerator between 36°F to 46°F (2°C to 8°C).
- Keep the Auto-injector in the original carton until use to protect it from light.
- Do not use an Auto-injector that has been left in direct sunlight.
- Do not freeze the Auto-injector. If the Auto-injector has been frozen, do not use the Auto-injector even if it is thawed.
- If needed, you may store the Auto-injector at room temperature up to 77°F (25°C) for up to 31 days.
- After the Auto-injector has reached room temperature, do not put it back in the refrigerator.
- Keep the Auto-injector and all medicines out of the reach of children.

Read Instructions on All Pages Before Using the Adalimumab-aaty Auto-injector

Prepare for Injection

1.Gather the supplies for the injection.1a. Prepare a clean, flat surface, such as a table or countertop, in a well-lit area.1b. Remove 1 Auto-injector from the carton stored in your refrigerator.1c. Make sure you have the following supplies:-Auto-injector-1 Alcohol swabNot included in the carton:-1 Cotton ball or gauze-1 Adhesive bandage-FDA-cleared sharps disposal container

2.Inspect the Auto-injector.2a. Make sure you have the correct medicine (Adalimumab-aaty) and dosage.2b. Check the expiration date on the label of the Auto-injector (see Figure B).2c. Look at the Auto-injector and make sure it is not cracked or damaged.

- Do not use the Auto-injector if;-it is cracked or damaged.-the expiration date has passed.

Figure B

3.Inspect the Medicine.3a. Look through the Window and make sure that the liquid is clear, colorless to pale brown, and free of particles (see Figure C).

- Do not use the Auto-injector if the liquid is the discolored (yellow or dark brown), cloudy, or contains particles in it.
- You may see air bubbles in the liquid. This is normal.

Figure C

4.Wait 15 to 30 minutes.4a. Leave the Auto-injector at room temperature 68°F to 77°F (20°C to 25°C) for 15 to 30 minutes to allow it to warm up (see Figure D).

- Do not warm the Auto-injector using heat sources such as hot water or a microwave.

Figure D

5.Choose an injection site (see Figure E).5a. You may inject into:-the front of your thighs.-your abdomen except for the 2 in (5 cm) around the belly button (navel).

- Do not inject into skin that is within 2 in (5 cm) of your belly button (navel), or is red, hard, tender, damaged, bruised, or scarred.
- If you have psoriasis, do not inject directly into any raised, thick, red or scaly skin patches or lesions on your skin.
- Do not inject through your clothes.

5b. Rotate the injection site each time you give an injection.

- Do not inject the same injection site each time you give an injection.
- Each new injection site should be at least 1.2 in (3 cm) away from the injection site you used before.

Figure E

6.Wash your hands.6a. Wash your hands with soap and water and dry them thoroughly (see Figure F).

Figure F

7.Clean the injection site.7a. Clean the injection site with an alcohol swab using a circular motion (see Figure G).7b. Let the skin dry before injecting.

- Do not blow on or touch the injection site again before giving the injection.

Figure G

Give the Injection8.Remove the Cap.8a. Hold the Auto-injector by the injector body with the Cap on top using one hand. Gently pull the Cap straight off with the other hand.

- Do not recap the Auto-injector.
- Do not remove the Cap until you are ready to inject.
- Do not touch the Needle or Needle Cover. Doing so may result in a needle stick injury because the Needle is inside the Needle Cover.

Figure H

8b. Dispose of the Cap in an FDA cleared sharps container (see Step 12 and Figure H).

9.Place the Auto-injector on the injection site.9a. Hold the Auto-injector so that you can see the Window.9b. Without pinching or stretching the skin, place the Auto-injector over the injection site at a 90-degree angle (see Figure I).

Figure I

10.Give the injection (see Figure J).10a. Press the Auto-injector firmly against the skin.

- When the injection starts you will hear the 1st loud "click" and the blue Plunger Rod will begin to fill the Window.

10b. Keep holding the Auto-injector firmly against the skin and listen for the 2nd loud "click." This can take up to 10 seconds.

- Do not change the position of the Auto-injector after the injection has started.

10c. After you hear the 2nd loud "click" continue to keep holding the Auto-injector firmly against the skin and count slowly to 5 to make sure you inject the full dose.10d. Look at the Auto-injector and make sure that the blue Plunger Rod is filling the Window completely.

Figure J

11.Remove the Auto-injector from your skin.11a. Remove the Auto-injector from your skin (see Figure K).

- After you remove the Auto-injector from the injection site, the needle will be automatically covered (see Figure L).
- If the Window has not turned completely blue or if the medicine is still injecting, this means you have not received a full dose. Call your doctor immediately.
- You may see grey stopper in the Window. This is normal.
- Some bleeding may occur.
- Do not reuse the Auto-injector.
- Do not rub the injection site.

Figure K

Figure L

After the Injection

12.Dispose of the Auto-injector.12a. Put the used Auto-injector in a FDA-cleared sharps disposal container right away after use (see Figure M).

- Do not throw away (dispose of) the Auto-injector in your household trash.
- If you do not have an FDA-cleared sharps disposal container, you may use a household container that is:-made of a heavy-duty plastic,-can be closed with a tight-fitting, puncture-resistant lid, without sharps being able to come out,-upright and stable during use,-leak-resistant, and-properly labeled to warn of hazardous waste inside the container.

Figure M

- When your sharps disposal container is almost full, you will need to follow your community guidelines for the right way to dispose of it. There may be state or local laws about how you should throw away used needles and syringes. For more information about safe sharps disposal, and for specific information about sharps disposal in the state that you live in, go to the FDA's website at: http://www.fda.gov/safesharpsdisposal.
- Do not dispose of your used sharps disposal container in your household trash unless your community guidelines permit this. Do not recycle your used sharps disposal container.

13.Care for the injection site.13a. Treat the injection site by gently pressing, not rubbing, a cotton ball or gauze to the site and apply an adhesive bandage, if necessary.

Manufactured by: CELLTRION, Inc., 23, Academy-ro, Yeonsu-gu, Incheon, 22014, Republic of Korea
US License Number 1996

Distributed by: CELLTRION USA, Inc., One Evertrust Plaza Suite 1207, Jersey City, NJ 07302

This Instructions for Use has been approved by the U.S. Food and Drug Administration.

Issued: 12/2024

INSTRUCTIONS FOR USE Adalimumab-aaty (ada-LIM-u-mab aaty) injection for subcutaneous use 80 mg/0.8 mL, 40 mg/0.4 mL Single-Dose Prefilled Syringe with Safety Guard This product is YUFLYMA (adalimumab-aaty).

For subcutaneous use only

Read and follow the Instructions for Use that come with your Adalimumab-aaty Prefilled Syringe before you start using it and each time you get a refill. There may be new information. This information does not take the place of talking to your doctor about your medical condition or treatment.

Figure A: Parts of Adalimumab-aaty Prefilled Syringe with Safety Guard

Important Information

- Use the Prefilled Syringe with Needle Guard only if your doctor has trained you on the right way to prepare for and to give an injection.
- Ask your doctor how often you will need to give an injection.
- Do not shake the Prefilled Syringe at any time.
- Do not remove the Cap until you are ready to inject.
- Do not share the Prefilled Syringe with anyone.
- Only use each Prefilled Syringe for one injection.
- Do not pull back on the plunger rod at any time.

How to store the Prefilled Syringe

- Store the Prefilled Syringe in a refrigerator between 36°F to 46°F (2°C to 8°C).
- Keep the Prefilled Syringe in the original carton to protect it from light.
- Do not use a Prefilled Syringe that has been left in direct sunlight.
- Do not freeze the Prefilled Syringe. If the Prefilled Syringe has been frozen, do not use the Prefilled Syringe even if it is thawed.
- If needed, you may store the Prefilled Syringe at room temperature up to 77°F (25°C) for up to 31 days.
- After the Prefilled Syringe has reached room temperature, do not put it back in the refrigerator.
- Keep the Prefilled Syringe and all medicines out of the reach of children.

Read Instructions on All Pages Before Using the Adalimumab-aaty Prefilled Syringe

Prepare for Injection

1.Gather the supplies for the injection.1a.Prepare a clean, flat surface, such as a table or countertop, in a well-lit area.1b. Remove 1 Prefilled Syringe from the carton stored in your refrigerator.

- Hold the Prefilled Syringe body when removing it from the carton. Do not touch the plunger rod.

1c. Make sure you have the following supplies:-Prefilled Syringe-1 Alcohol swabNot included in the carton:-1 Cotton ball or gauze-1 Adhesive bandage-FDA-cleared sharps disposal container

2.Inspect the Prefilled Syringe.2a. Make sure you have the correct medicine (Adalimumab-aaty) and dosage.2b. Check the expiration date on the label of the Prefilled Syringe (see Figure B).2c. Look at the Prefilled Syringe and make sure it is not cracked or damaged.

- Do not use the Prefilled Syringe if;-it is cracked or damaged.-the expiration date has passed.

Figure B

3.Inspect the Medicine.3a. Look at the Medicine and confirm that the liquid is clear, colorless to pale brown, and free of particles
(see Figure C).

- Do not use the Prefilled Syringe if the liquid is the discolored (yellow or dark brown), cloudy, or contains particles in it.
- You may see air bubbles in the liquid. This is normal.

Figure C

4.Wait 15 to 30 minutes.4a. Leave the Prefilled Syringe at room temperature 68°F to 77°F (20°C to 25°C) for 15 to 30 minutes to allow it to warm up (see Figure D).

- Do not warm the Prefilled Syringe using heat sources such as hot water or a microwave.

Figure D

5.Choose an injection site (see Figure E).5a. You may inject into:-the front of your thighs.-your abdomen except for the 2 in (5 cm) around the belly button (navel).

- Do not inject into skin that is within 2 in (5 cm) of your belly button (navel), or is red, hard, tender, damaged, bruised, or scarred.
- If you have psoriasis, do not inject directly into any raised, thick, red or scaly skin patches or lesions on your skin.
- Do not inject through your clothes.

5b. Rotate the injection site each time you give an injection. Each new injection site should be at least 1.2 in (3 cm) away from the injection site you used before.

Figure E

6.Wash your hands.6a. Wash your hands with soap and water and dry them thoroughly (see Figure F).

Figure F

7.Clean the injection site.7a. Clean the injection site with an alcohol swab using a circular motion (see Figure G).7b. Let the skin dry before injecting.

- Do not blow on or touch the injection site again before giving the injection.

Figure G

Give the Injection8.Remove the Cap.8a. Hold the Prefilled Syringe by the injector body with the Cap on top using one hand. Gently pull the Cap straight off with the other hand.

- Do not pull back on the plunger rod at any time.
- Do not recap the Prefilled Syringe.
- Do not remove the Cap until you are ready to inject.
- Do not touch the Needle. Doing so may result in a needle stick injury.

8b. Dispose of the Cap in an FDA cleared sharps container (see Step 12 and Figure H).

Figure H

9.Insert the Prefilled Syringe into the injection site.9a. Gently pinch a fold of skin at the injection site with one hand.9b. With a quick and "dart-like" motion, insert the Needle completely into the fold of the skin at a 45-degree angle (see Figure I).

- Do not change the position of the Prefilled Syringe after the injection has started.

Figure I

10.Give the injection.10a. After the Needle is inserted, release the pinch.10b. Slowly push the Plunger all the way down until all of the liquid is injected and the Syringe is empty
(see Figure J).

Figure J

11.Remove the Prefilled Syringe from the injection site.11a. After the Prefilled Syringe is empty, slowly lift your thumb from the Plunger until Needle is completely covered by the Needle Guard (see Figure K).

- Some bleeding may occur.
- Do not reuse the Prefilled Syringe.
- Do not touch or recap the needle.
- Do not rub the injection site.

Figure K

After the Injection

12.Dispose of the Prefilled Syringe.12a. Put the used Prefilled Syringe in a FDA-cleared sharps disposal container right away after use (see Figure L).

- Do not throw away (dispose of) the Prefilled Syringe in your household trash.
- If you do not have an FDA-cleared sharps disposal container, you may use a household container that is:-made of a heavy-duty plastic,-can be closed with a tight-fitting, puncture-resistant lid, without sharps being able to come out,-upright and stable during use,-leak-resistant, and-properly labeled to warn of hazardous waste inside the container.

Figure L

- When your sharps disposal container is almost full, you will need to follow your community guidelines for the right way to dispose of it. There may be state or local laws about how you should throw away used needles and syringes. For more information about safe sharps disposal, and for specific information about sharps disposal in the state that you live in, go to the FDA's website at: http://www.fda.gov/safesharpsdisposal.
- Do not dispose of your used sharps disposal container in your household trash unless your community guidelines permit this. Do not recycle your used sharps disposal container.

13.Care for the injection site.13a. Treat the injection site by gently pressing, not rubbing, a cotton ball or gauze to the site and apply an adhesive bandage, if necessary.

Manufactured by: CELLTRION, Inc., 23, Academy-ro, Yeonsu-gu, Incheon, 22014, Republic of Korea
US License Number 1996

Distributed by: CELLTRION USA, Inc., One Evertrust Plaza Suite 1207, Jersey City, NJ 07302

This Instructions for Use has been approved by the U.S. Food and Drug Administration.

Issued: 12/2024

INSTRUCTIONS FOR USE Adalimumab-aaty (ada-LIM-u-mab aaty) injection, for subcutaneous use 80 mg/0.8 mL, 40 mg/0.4 mL, 20 mg/0.2 mL Single-Dose Prefilled Syringe This product is YUFLYMA (adalimumab-aaty).

For subcutaneous use only

Read and follow the Instructions for Use that come with your Adalimumab-aaty Prefilled Syringe before you start using it and each time you get a refill. There may be new information. This information does not take the place of talking to your doctor about your medical condition or treatment.

Figure A: Parts of Adalimumab-aaty Prefilled Syringe

Important Information

- Use the Prefilled Syringe only if your doctor has trained you on the right way to prepare for and to give an injection.
- Ask your doctor how often you will need to give an injection.
- Do not shake the Prefilled Syringe at any time.
- Do not remove the Cap until you are ready to inject.
- Do not share the Prefilled Syringe with anyone.
- Do not pull back on the plunger rod at any time.

How to store the Prefilled Syringe

- Store the Prefilled Syringe in a refrigerator between 36°F to 46°F (2°C to 8°C).
- Keep the Prefilled Syringe in the original carton to protect it from light.
- Do not use a Prefilled Syringe that has been left in direct sunlight.
- Do not freeze the Prefilled Syringe. If the Prefilled Syringe has been frozen, do not use the Prefilled Syringe even if it is thawed.
- If needed, you may store the Prefilled Syringe at room temperature up to 77°F (25°C) for up to 31 days.
- After the Prefilled Syringe has reached room temperature, do not put it back in the refrigerator.
- Keep the Prefilled Syringe and all medicines out of the reach of children.

Read Instructions on All Pages Before Using the Adalimumab-aaty Prefilled Syringe

Prepare for Injection

1.Gather the supplies for the injection.1a. Prepare a clean, flat surface, such as a table or countertop, in a well-lit area.1b. Remove 1 Prefilled Syringe from the carton stored in your refrigerator.

- Hold the Prefilled Syringe body when removing it from the carton. Do not touch the plunger rod.

1c. Make sure you have the following supplies:-Prefilled Syringe-1 Alcohol swabNot included in the carton:-1 Cotton ball or gauze-1 Adhesive bandage-FDA-cleared sharps disposal container

2.Inspect the Prefilled Syringe.2a. Make sure you have the correct medicine (Adalimumab-aaty) and dosage.2b. Check the expiration date on the label of the Prefilled Syringe (see Figure B)2c. Look at the Prefilled Syringe and make sure it is not cracked or damaged.

- Do not use the Prefilled Syringe if;-it is cracked or damaged.-the expiration date has passed.

Figure B

3.Inspect the Medicine.3a. Look at the Medicine and confirm that the liquid is clear, colorless to pale brown, and free of particles (see Figure C).

- Do not use the Prefilled Syringe if the liquid is the discolored (yellow or dark brown), cloudy, or contains particles in it.
- You may see air bubbles in the liquid. This is normal.

Figure C

4.Wait 15 to 30 minutes.4a. Leave the Prefilled Syringe at room temperature 68°F to 77°F (20°C to 25°C) for 15 to 30 minutes to allow it to warm up (see Figure D).

- Do not warm the Prefilled Syringe using heat sources such as hot water or a microwave.

Figure D

5.Choose an injection site (see Figure E).5a. You may inject into:-the front of your thighs.-your abdomen except for the 2 in (5 cm) around the belly button (navel).

- Do not inject into skin that is within 2 in (5 cm) of your belly button (navel), or is red, hard, tender, damaged, bruised, or scarred.
- If you have psoriasis, do not inject directly into any raised, thick, red or scaly skin patches or lesions on your skin.
- Do not inject through your clothes.

5b. Rotate the injection site each time you give an injection. Each new injection site should be at least 1.2 in (3 cm) away from the injection site you used before.

Figure E

6.Wash your hands.6a. Wash your hands with soap and water and dry them thoroughly (see Figure F).

Figure F

7.Clean the injection site.7a. Clean the injection site with an alcohol swab using a circular motion (see Figure G).7b. Let the skin dry before injecting.

- Do not blow on or touch the injection site again before giving the injection.

Figure G

Give the Injection8.Remove the Cap.8a. Hold the Prefilled Syringe by the injector body with the Cap on top using one hand. Gently pull the Cap straight off with the other hand.

- Do not pull back on the plunger rod at any time.
- Do not recap the Prefilled Syringe.
- Do not remove the Cap until you are ready to inject.
- Do not touch the Needle. Doing so may result in a needle stick injury.

8b. Dispose of the Cap in an FDA cleared sharps container (see Step 12 and Figure H).

Figure H

9.Insert the Prefilled Syringe into the injection site.9a. Gently pinch a fold of skin at the injection site with one hand.9b. With a quick and "dart-like" motion, insert the Needle completely into the fold of the skin at a 45-degree angle (see Figure I).

- Do not change the position of the Prefilled Syringe after the injection has started.

Figure I

10.Give the injection.10a. After the Needle is inserted, release the pinch.10b. Slowly push the Plunger all the way down until all of the liquid is injected and the Syringe is empty (see Figure J).

Figure J

11.Remove the Prefilled Syringe from the injection site.11a. After the Prefilled Syringe is empty, remove the Prefilled Syringe from your skin (see Figure K).

- Some bleeding may occur.
- Do not reuse the Prefilled Syringe.
- Do not touch the Needle.
- Do not rub the injection site.

Figure K

After the Injection

12.Dispose of the Prefilled Syringe.12a. Put the used Prefilled Syringe in a FDA-cleared sharps disposal container right away after use (see Figure L).

- Do not throw away (dispose of) the Prefilled Syringe in your household trash.
- If you do not have an FDA-cleared sharps disposal container, you may use a household container that is:-made of a heavy-duty plastic,-can be closed with a tight-fitting, puncture-resistant lid, without sharps being able to come out,-upright and stable during use,-leak-resistant, and-properly labeled to warn of hazardous waste inside the container.

Figure L

- When your sharps disposal container is almost full, you will need to follow your community guidelines for the right way to dispose of it. There may be state or local laws about how you should throw away used needles and syringes. For more information about safe sharps disposal, and for specific information about sharps disposal in the state that you live in, go to the FDA's website at: http://www.fda.gov/safesharpsdisposal.
- Do not dispose of your used sharps disposal container in your household trash unless your community guidelines permit this. Do not recycle your used sharps disposal container.

13.Care for the injection site.13a. Treat the injection site by gently pressing, not rubbing, a cotton ball or gauze to the site and apply an adhesive bandage, if necessary.

Manufactured by: CELLTRION, Inc., 23, Academy-ro, Yeonsu-gu, Incheon, 22014, Republic of Korea
US License Number 1996

Distributed by: CELLTRION USA, Inc., One Evertrust Plaza Suite 1207, Jersey City, NJ 07302

This Instructions for Use has been approved by the U.S. Food and Drug Administration.

Issued: 12/2024

PRINCIPAL DISPLAY PANEL - 40 mg/0.4 mL Auto-injector Label

NDC 72606-022-09
Rx only

Adalimumab-aaty 40 mg/0.4 mL
injection

Subcutaneous use

CELLTRION Inc.

LM-0000-00

Lot: Exp:

- PRINCIPAL DISPLAY PANEL - 40 mg/0.4 mL Auto-injector Carton 1PK

1 Single-dose Auto-injector

Rx only

Adalimumab-aaty 40 mg/0.4 mL

FOR SUBCUTANEOUS USE ONLY

1 auto-injector + 2 alcohol preps

NDC 72606-022-09

CELLTRION Inc.

- PRINCIPAL DISPLAY PANEL - 40 mg/0.4 mL Auto-injector Carton 2PK

2 Single-dose Auto-injector

Rx only

Adalimumab-aaty 40 mg/0.4 mL

FOR SUBCUTANEOUS USE ONLY

2 auto-injector + 2 alcohol preps

NDC 72606-022-10

CELLTRION Inc.

- PRINCIPAL DISPLAY PANEL - 40 mg/0.4 mL Auto-injector Carton 4PK

4 Single-dose Auto-injector

Rx only

Adalimumab-aaty 40 mg/0.4 mL

FOR SUBCUTANEOUS USE ONLY

4 auto-injector + 4 alcohol preps

NDC 72606-022-11

CELLTRION Inc.

- PRINCIPAL DISPLAY PANEL - 40 mg/0.4 mL Auto-injector Carton 6PK

6 Single-dose Auto-injector

Rx only

Adalimumab-aaty 40 mg/0.4 mL

FOR SUBCUTANEOUS USE ONLY

6 auto-injector + 6 alcohol preps

NDC 72606-022-12

CELLTRION Inc.

PRINCIPAL DISPLAY PANEL - 40 mg/0.4 mL Syringe Label- with Guard

Lot:
EXP:

NDC 72606-022-05
Rx only

Adalimumab-aaty 40 mg/0.4 mL
injection

Subcutaneous use

CELLTRION Inc.

LM000000-00000

PRINCIPAL DISPLAY PANEL - 40 mg/0.4 mL Syringe Carton - with Guard

- 40 mg/0.4 mL Syringe Carton - with Guard 1PK

1 Single-dose Prefilled Syringe with Safety Guard

Rx only

Adalimumab-aaty 40 mg/0.4 mL

FOR SUBCUTANEOUS USE ONLY

1 prefilled syringe with safety guard + 2 alcohol preps

NDC 72606-022-05

CELLTRION Inc.

- 40 mg/0.4 mL Syringe Carton - with Guard 2PK

2 Single-dose Prefilled Syringe with Safety Guard

Rx only

Adalimumab-aaty 40 mg/0.4 mL

FOR SUBCUTANEOUS USE ONLY

2 prefilled syringe with safety guard + 2 alcohol preps

NDC 72606-022-06

CELLTRION Inc.

- 40 mg/0.4 mL Syringe Carton - with Guard 4PK

4 Single-dose Prefilled Syringe with Safety Guard

Rx only

Adalimumab-aaty 40 mg/0.4 mL

FOR SUBCUTANEOUS USE ONLY

4 prefilled syringe with safety guard + 4 alcohol preps

NDC 72606-022-07

CELLTRION Inc.

- 40 mg/0.4 mL Syringe Carton - with Guard 6PK

6 Single-dose Prefilled Syringe with Safety Guard

Rx only

Adalimumab-aaty 40 mg/0.4 mL

FOR SUBCUTANEOUS USE ONLY

6 prefilled syringe with safety guard + 6 alcohol preps

NDC 72606-022-08

CELLTRION Inc.

PRINCIPAL DISPLAY PANEL - 40 mg/0.4 mL Syringe Label

Lot:
EXP:

NDC 72606-022-01
Rx only

Adalimumab-aaty 40 mg/0.4 mL
injection

Subcutaneous use

CELLTRION Inc.

LM000000-00000

PRINCIPAL DISPLAY PANEL - 40 mg/0.4 mL Syringe Carton

- 40 mg/0.4 mL Syringe Carton 1PK

1 Single-dose Prefilled Syringe
Rx only Adalimumab-aaty 40 mg/0.4 mL

FOR SUBCUTANEOUS USE ONLY

1 prefilled syringe + 2 alcohol preps

NDC 72606-022-01

CELLTRION Inc.

- 40 mg/0.4 mL Syringe Carton 2PK

2 Single-dose Prefilled Syringe
Rx only Adalimumab-aaty 40 mg/0.4 mL

FOR SUBCUTANEOUS USE ONLY

2 prefilled syringe + 2 alcohol preps

NDC 72606-022-02

CELLTRION Inc.

- 40 mg/0.4 mL Syringe Carton 4PK

4 Single-dose Prefilled Syringe
Rx only Adalimumab-aaty 40 mg/0.4 mL

FOR SUBCUTANEOUS USE ONLY

4 prefilled syringe + 4 alcohol preps

NDC 72606-022-03

CELLTRION Inc.

- 40 mg/0.4 mL Syringe Carton 6PK

6 Single-dose Prefilled Syringe
Rx only Adalimumab-aaty 40 mg/0.4 mL

FOR SUBCUTANEOUS USE ONLY

6 prefilled syringe + 6 alcohol preps

NDC 72606-022-04

CELLTRION Inc.

PRINCIPAL DISPLAY PANEL - 80 mg/0.8 mL Auto-injector Label

NDC 72606-040-04
Rx only

Adalimumab-aaty 80 mg/0.8 mL
injection

Subcutaneous use

CELLTRION Inc.

LM-0000-00

Lot: Exp:

- PRINCIPAL DISPLAY PANEL - 80 mg/0.8 mL Auto-injector Carton 1PK

1 Single-dose Auto-injector

Rx only

Adalimumab-aaty 80 mg/0.8 mL

FOR SUBCUTANEOUS USE ONLY

1 auto-injector + 2 alcohol preps

NDC 72606-040-04

CELLTRION Inc.

- PRINCIPAL DISPLAY PANEL - 80 mg/0.8 mL Auto-injector Carton 2PK

2 Single-dose Auto-injector

Rx only

Adalimumab-aaty 80 mg/0.8 mL

FOR SUBCUTANEOUS USE ONLY

2 auto-injector + 2 alcohol preps

NDC 72606-040-05

CELLTRION Inc.

PRINCIPAL DISPLAY PANEL - 80 mg/0.8 mL Syringe Label- with Guard

Lot:
EXP:

NDC 72606-040-02
Rx only

Adalimumab-aaty 80 mg/0.8 mL
injection

Subcutaneous use

CELLTRION Inc.

LM000000-00000

PRINCIPAL DISPLAY PANEL - 80 mg/0.8 mL Syringe Carton - with Guard

- 80 mg/0.8 mL Syringe Carton - with Guard 1PK

1 Single-dose Prefilled Syringe with Safety Guard

Rx only

Adalimumab-aaty 80 mg/0.8 mL

FOR SUBCUTANEOUS USE ONLY

1 prefilled syringe with safety guard + 2 alcohol preps

NDC 72606-040-02

CELLTRION Inc.

- 80 mg/0.8 mL Syringe Carton - with Guard 2PK

2 Single-dose Prefilled Syringe with Safety Guard

Rx only

Adalimumab-aaty 80 mg/0.8 mL

FOR SUBCUTANEOUS USE ONLY

2 prefilled syringe with safety guard + 2 alcohol preps

NDC 72606-040-03

CELLTRION Inc.

PRINCIPAL DISPLAY PANEL - 80 mg/0.8 mL Syringe Label

Lot:
EXP:

NDC 72606-040-01
Rx only

Adalimumab-aaty 80 mg/0.8 mL
injection

Subcutaneous use

CELLTRION Inc.

LM000000-00000

PRINCIPAL DISPLAY PANEL - 80 mg/0.8 mL Syringe Carton

- 80 mg/0.8 mL Syringe Carton 1PK

1 Single-dose Prefilled Syringe
Rx only Adalimumab-aaty 80 mg/0.8 mL

FOR SUBCUTANEOUS USE ONLY

1 prefilled syringe + 2 alcohol preps

NDC 72606-040-01

CELLTRION Inc.

PRINCIPAL DISPLAY PANEL - 20 mg/0.2 mL Syringe Label

Lot:
EXP:

NDC 72606-041-01
Rx only

Adalimumab-aaty 20 mg/0.2 mL
injection

Subcutaneous use

CELLTRION Inc.

LM000000-00000

PRINCIPAL DISPLAY PANEL - 20 mg/0.2 mL Syringe Carton

- 20 mg/0.2 mL Syringe Carton 2PK

2 Single-dose Prefilled Syringes
Rx only Adalimumab-aaty 20 mg/0.2 mL
FOR SUBCUTANEOUS USE ONLY

2 prefilled syringes + 2 alcohol preps

NDC 72606-041-01

CELLTRION Inc.

PRINCIPAL DISPLAY PANEL - Kit Carton (STARTER PACKAGE - 80 mg/0.8 mL Auto-injector)

TARTER PACKAGE 80 mg/0.8 mL Auto-injector Carton

NDC 72606-040-06

Rx only

Adalimumab-aaty

injection

80 mg/0.8 mL

FOR SUBCUTANEOUS USE ONLY

ATTENTION: Dispense the enclosed

Medication Guide to each patient

STARTER PACKAGE

CROHN'S DISEASE

Each carton contains 3 single-dose Auto-injector.

4 alohol preps, 1 Medication Guide.

1 Prescribing Information, and 1 Instriction for Use

3 Single-dose

Auto-Injector

CELLTRION